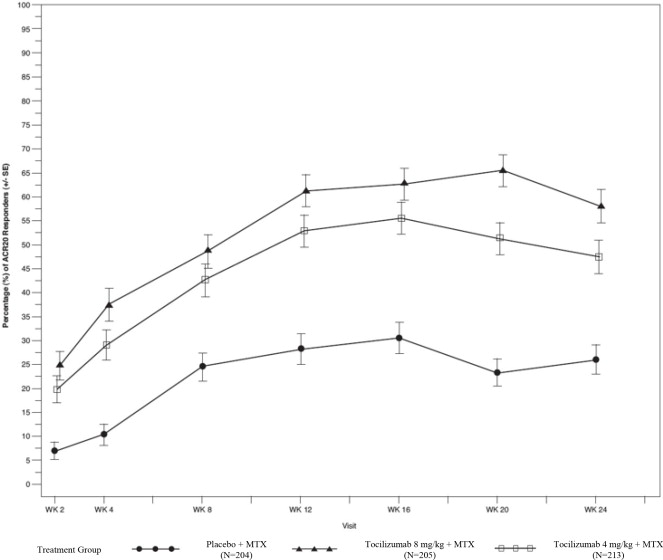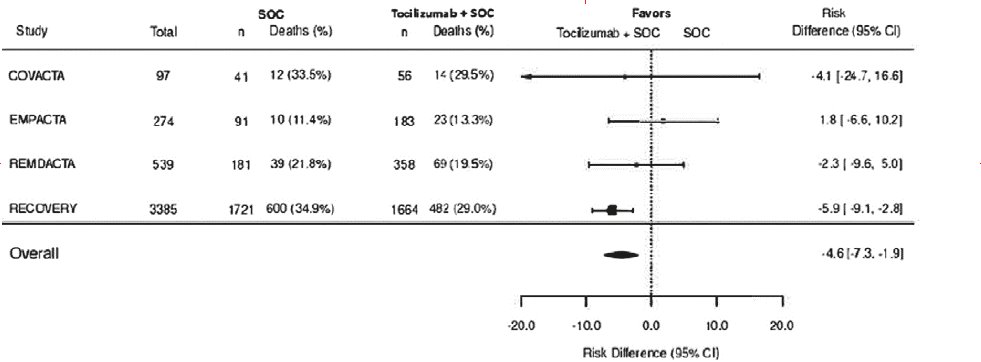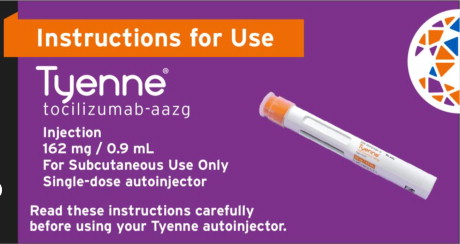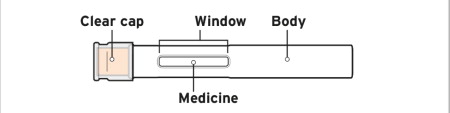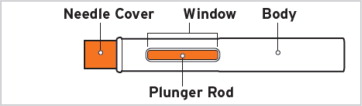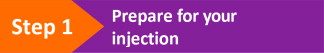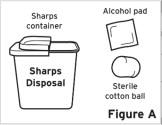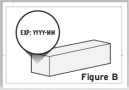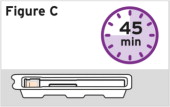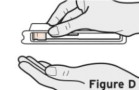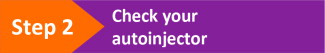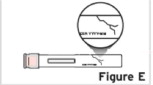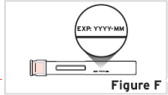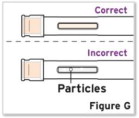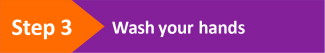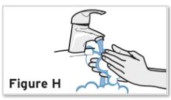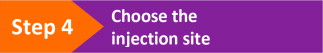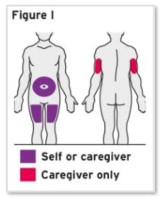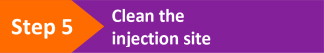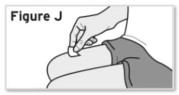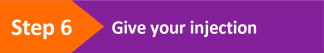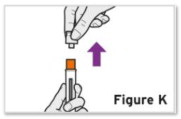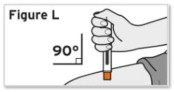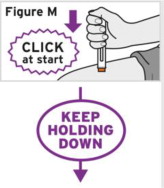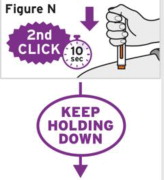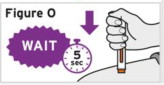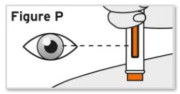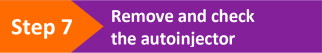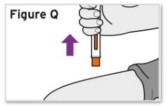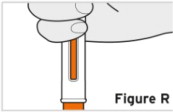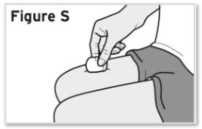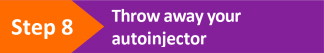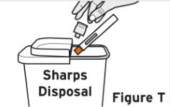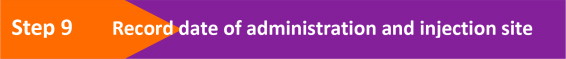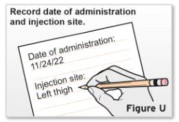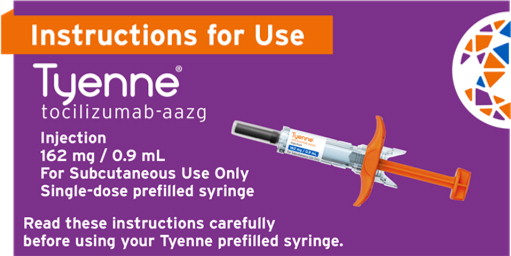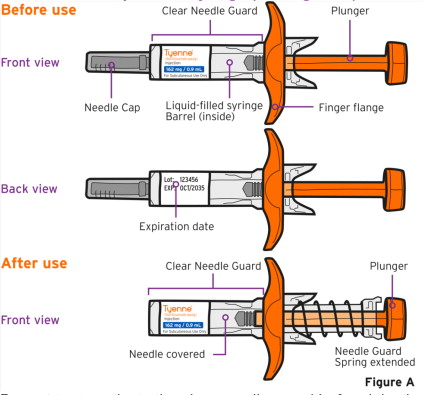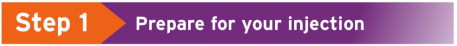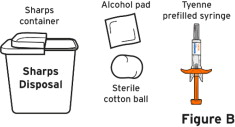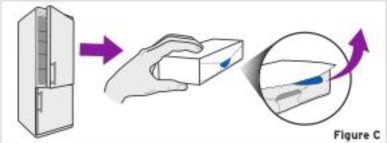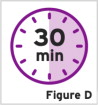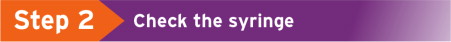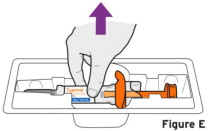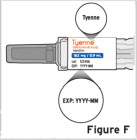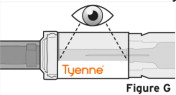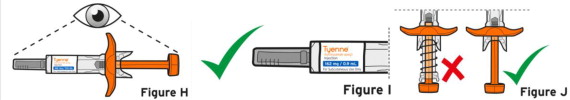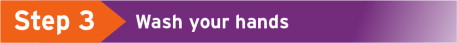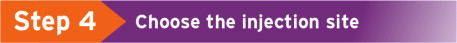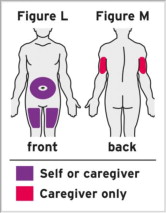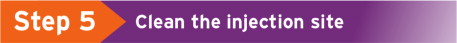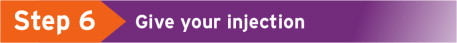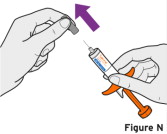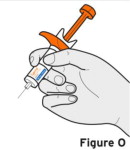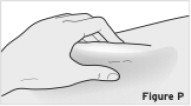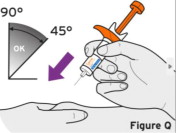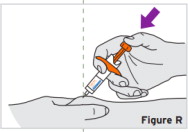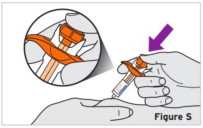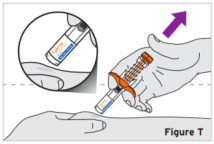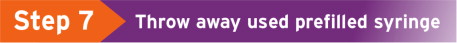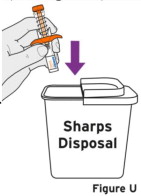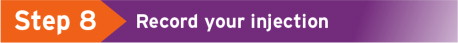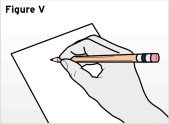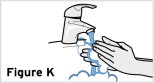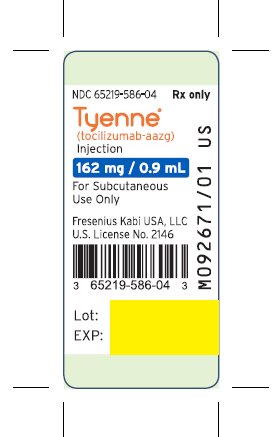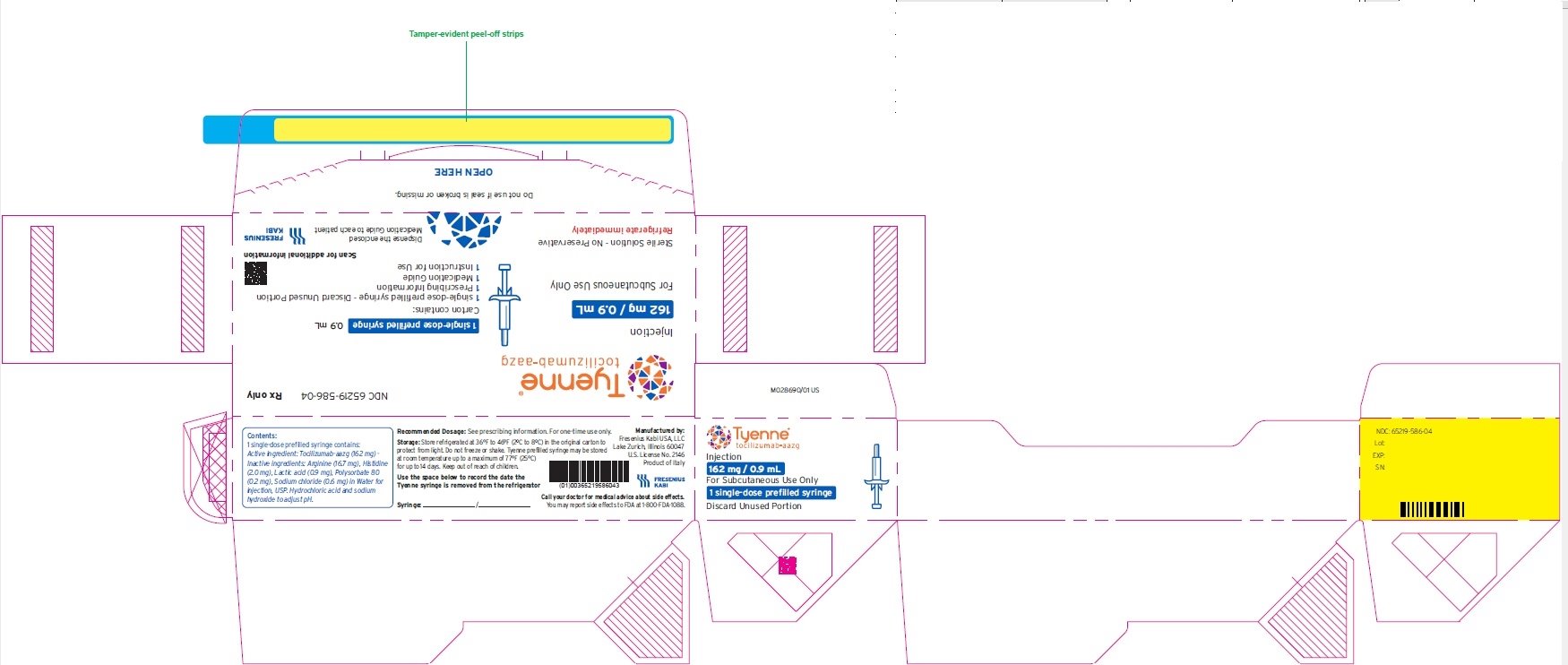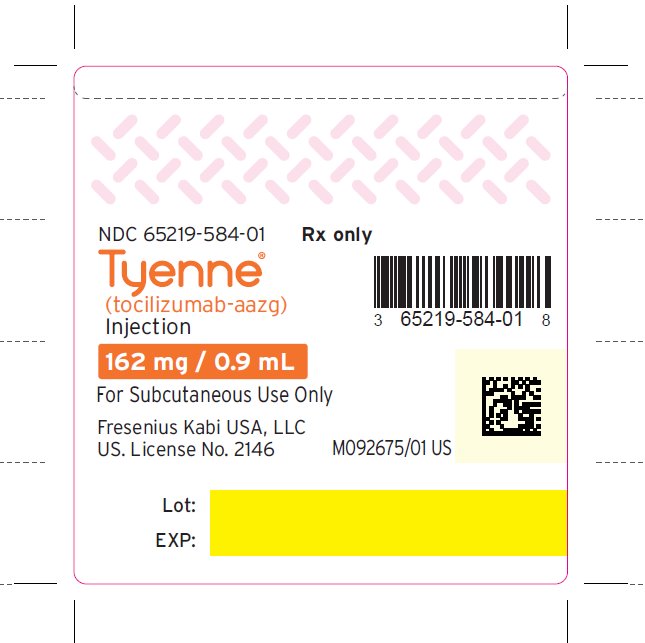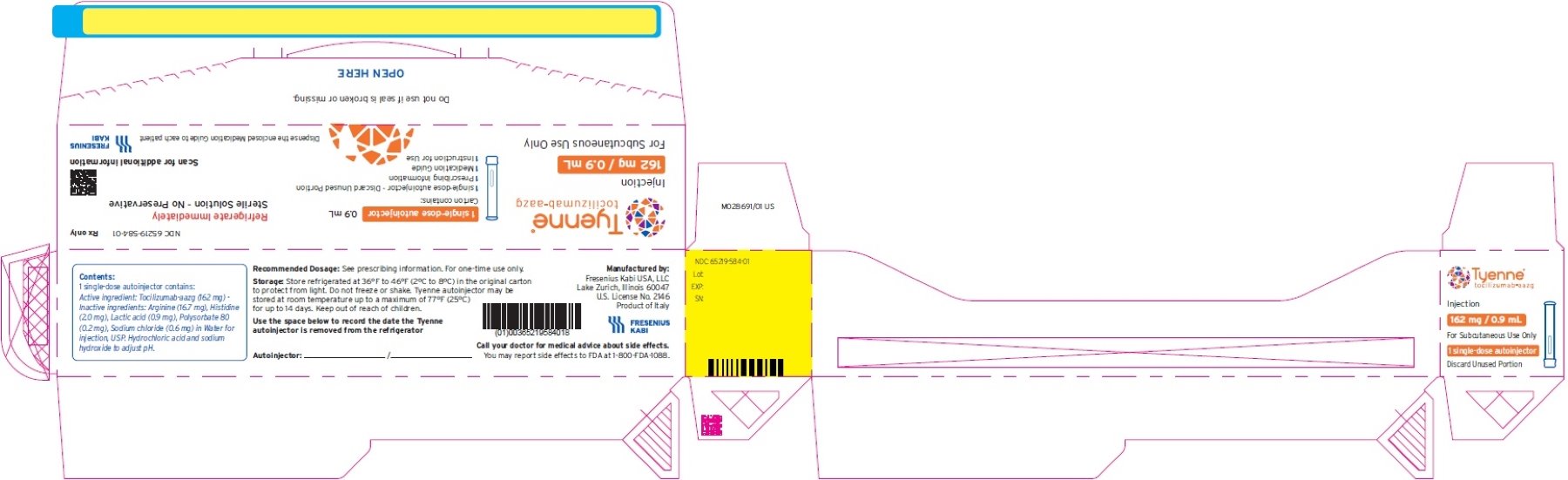 DRUG LABEL: TYENNE
NDC: 65219-586 | Form: INJECTION, SOLUTION
Manufacturer: Fresenius Kabi USA, LLC
Category: prescription | Type: HUMAN PRESCRIPTION DRUG LABEL
Date: 20251126

ACTIVE INGREDIENTS: TOCILIZUMAB 162 mg/0.9 mL
INACTIVE INGREDIENTS: Arginine; Histidine; Lactic acid, L-; Polysorbate 80; Sodium chloride; Water; Hydrochloric acid; Sodium hydroxide

HIGHLIGHTS OF PRESCRIBING INFORMATION

These highlights do not include all the information needed to use TYENNE safely and effectively. See full prescribing information for TYENNE.
TYENNE® (tocilizumab-aazg) injection, for intravenous or subcutaneous use
Initial U.S. Approval: 2024
TYENNE® (tocilizumab-aazg) is biosimilar [Biosimilar means that the biological product is approved based on data demonstrating that it is highly similar to an FDA-approved biological product, known as a reference product, and that there are no clinically meaningful differences between the biosimilar product and the reference product. Biosimilarity of TYENNE has been demonstrated for the condition(s) of use (e.g., indication(s), dosing regimen(s), strength(s), dosage form(s), and route(s) of administration) described in its Full Prescribing Information.] to ACTEMRA® (tocilizumab).

RECENT MAJOR CHANGES

Indications and Usage (1.5, 1.6) 02/2025

Dosage and Administration (2.1, 2.6, 2.7) 02/2025

Warnings and Precautions (5.1, 5.3, 5.4) 02/2025

Warnings and Precautions (5.6) 12/2024

WARNING: RISK OF SERIOUS INFECTIONS

See full prescribing information for complete boxed warning.

- Serious infections leading to hospitalization or death including tuberculosis (TB), bacterial, invasive fungal, viral, and other opportunistic infections have occurred in patients receiving tocilizumab products. (5.1)
- If a serious infection develops, interrupt TYENNE until the infection is controlled. (5.1)
- Perform test for latent TB (except patients with COVID-19); if positive, start treatment for TB prior to starting TYENNE. (5.1)
- Monitor all patients for active TB during treatment, even if initial latent TB test is negative. (5.1)

1 INDICATIONS AND USAGE

TYENNE® (tocilizumab-aazg) is an interleukin-6 (IL-6) receptor antagonist indicated for treatment of:

Rheumatoid Arthritis (RA) (1.1)

- Adult patients with moderately to severely active rheumatoid arthritis who have had an inadequate response to one or more Disease-Modifying Anti-Rheumatic Drugs (DMARDs).

Giant Cell Arteritis (GCA) (1.2)

- Adult patients with giant cell arteritis.

Polyarticular Juvenile Idiopathic Arthritis (PJIA) (1.3)

- Patients 2 years of age and older with active polyarticular juvenile idiopathic arthritis.

Systemic Juvenile Idiopathic Arthritis (SJIA) (1.4)

- Patients 2 years of age and older with active systemic juvenile idiopathic arthritis.

Cytokine Release Syndrome (CRS) (1.5)

- Adults and pediatric patients 2 years of age and older with chimeric antigen receptor (CAR) T cell-induced severe or life-threatening cytokine release syndrome.

Coronavirus Disease 2019 (COVID-19) (1.6)

- Hospitalized adult patients with coronavirus disease 2019 (COVID-19) who are receiving systemic corticosteroids and require supplemental oxygen, non-invasive or invasive mechanical ventilation, or extracorporeal membrane oxygenation (ECMO).

2 DOSAGE AND ADMINISTRATION

For RA, pJIA and sJIA, TYENNE may be used alone or in combination with methotrexate; and in RA, other non-biologic DMARDs may be used. (2)

General Administration and Dosing Information (2.1)

- RA, GCA, PJIA and SJIA – It is recommended that TYENNE not be initiated in patients with an absolute neutrophil count (ANC) below 2,000 per mm^3, platelet count below 100,000 per mm^3, or ALT or AST above 1.5 times the upper limit of normal (ULN) (5.3, 5.4).
- COVID-19 – It is recommended that TYENNE not be initiated in patients with an absolute neutrophil count (ANC) below 1,000 per mm^3, platelet count below 50,000 mm^3, or ALT or AST above 10 times ULN (5.3, 5.4).
- In RA, CRS or COVID-19 patients, TYENNE doses exceeding 800 mg per infusion are not recommended. (2.2, 2.9, 12.3)
- In GCA patients, TYENNE doses exceeding 600 mg per infusion are not recommended. (2.3, 12.3)

Rheumatoid Arthritis (2.2)

Recommended Adult Intravenous Dosage:

When used in combination with non-biologic DMARDs or as monotherapy the recommended starting dose is 4 mg per kg every 4 weeks followed by an increase to 8 mg per kg every 4 weeks based on clinical response.

Recommended Adult Subcutaneous Dosage:

Patients less than 100 kg weight | 162 mg administered subcutaneously every other week, followed by an increase to every week based on clinical response
Patients at or above 100 kg weight | 162 mg administered subcutaneously every week

Giant Cell Arteritis (2.3)

Recommended Adult Intravenous Dosage: The recommended dose is 6 mg per kg every 4 weeks in combination with a tapering course of glucocorticoids. TYENNE can be used alone following discontinuation of glucocorticoids.

Recommended Adult Subcutaneous Dosage: The recommended dose is 162 mg given once every week as a subcutaneous injection, in combination with a tapering course of glucocorticoids.

A dose of 162 mg given once every other week as a subcutaneous injection, in combination with a tapering course of glucocorticoids, may be prescribed based on clinical considerations.

TYENNE can be used alone following discontinuation of glucocorticoids.

Polyarticular Juvenile Idiopathic Arthritis (2.4)

Recommended Intravenous PJIA Dosage Every 4 Weeks
Patients less than 30 kg weight | 10 mg per kg
Patients at or above 30 kg weight | 8 mg per kg

Recommended Subcutaneous PJIA Dosage
Patients less than 30 kg weight | 162 mg once every three weeks
Patients at or above 30 kg weight | 162 mg once every two weeks

Systemic Juvenile Idiopathic Arthritis (2.5)

Recommended Intravenous SJIA Dosage Every 2 Weeks
Patients less than 30 kg weight | 12 mg per kg
Patients at or above 30 kg weight | 8 mg per kg

Recommended Subcutaneous SJIA Dosage
Patients less than 30 kg weight | 162 mg every two weeks
Patients at or above 30 kg weight | 162 mg every week

Cytokine Release Syndrome (2.6)

Recommended Intravenous CRS Dosage
Patients less than 30 kg weight | 12 mg per kg
Patients at or above 30 kg weight | 8 mg per kg
Alone or in combination with corticosteroids.

Coronavirus Disease 2019 (2.7)

The recommended dosage of TYENNE for adult patients with COVID-19 is 8 mg per kg administered by a 60-minute intravenous infusion.

Administration of Intravenous formulation (2.8)

- For patients with RA, GCA, COVID-19, CRS, PJIA, SJIA patients at or above 30 kg, dilute to 100 mL in 0.9% or 0.45% Sodium Chloride Injection, USP for intravenous infusion using aseptic technique.
- For PJIA, SJIA and CRS patients less than 30 kg, dilute to 50 mL in 0.9% or 0.45% Sodium Chloride Injection, USP for intravenous infusion using aseptic technique.
- Administer as a single intravenous drip infusion over 1 hour; do not administer as bolus or push.

Administration of Subcutaneous formulation (2.9)

- Follow the Instructions for Use for prefilled syringe and prefilled autoinjector

Dose Modifications (2.10)

Recommended for management of certain dose-related laboratory changes including elevated liver enzymes, neutropenia, and thrombocytopenia.

3 DOSAGE FORMS AND STRENGTHS

Intravenous Infusion

Injection: 80 mg/4 mL (20 mg/mL), 200 mg/10 mL (20 mg/mL), 400 mg/20 mL (20 mg/mL) in single-dose vials for further dilution prior to intravenous infusion (3)

Subcutaneous Injection

Injection: 162 mg/0.9 mL in a single-dose prefilled syringe or single-dose prefilled autoinjector (3)

4 CONTRAINDICATIONS

Known hypersensitivity to tocilizumab products. (4)

5 WARNINGS AND PRECAUTIONS

- Serious Infections – do not administer TYENNE during an active infection, including localized infections. If a serious infection develops, interrupt TYENNE until the infection is controlled. (5.1)
- Gastrointestinal (GI) perforation-use with caution in patients who may be at increased risk. (5.2)
- Hepatotoxicity- Monitor patients for signs and symptoms of hepatic injury. Modify or discontinue TYENNE if abnormal liver tests persist or worsen or if clinical signs and symptoms of liver disease develop. (2.10, 5.3)
- Laboratory monitoring-recommended due to potential consequences of treatment-related changes in neutrophils, platelets, lipids, and liver function tests. (2.10, 5.4)
- Hypersensitivity reactions, including anaphylaxis and death and serious cutaneous reactions including Drug Reaction with Eosinophilia and Systemic Symptoms (DRESS) - discontinue TYENNE, treat promptly, and monitor until reaction resolves (5.6)
- Live vaccines-Avoid use with TYENNE (5.9, 7.3)

6 ADVERSE REACTIONS

Most common adverse reactions (incidence of at least 5%): upper respiratory tract infections, nasopharyngitis, headache, hypertension, increased ALT, injection site reactions. (6)

To report SUSPECTED ADVERSE REACTIONS, contact Fresenius Kabi USA, LLC at 1-800-551-7176 or FDA at 1-800-FDA-1088 or www.fda.gov/medwatch

8 USE IN SPECIFIC POPULATIONS

- Pregnancy: Based on animal data, may cause fetal harm. (8.1)
- Lactation: Discontinue drug or nursing taking into consideration importance of drug to mother. (8.2)

FULL PRESCRIBING INFORMATION

WARNING: RISK OF SERIOUS INFECTIONS

Patients treated with tocilizumab products including TYENNE are at increased risk for developing serious infections that may lead to hospitalization or death [see Warnings and Precautions (5.1), Adverse Reactions (6.1)]. Most patients who developed these infections were taking concomitant immunosuppressants such as methotrexate or corticosteroids.

If a serious infection develops, interrupt TYENNE until the infection is controlled.

Reported infections include:

- Active tuberculosis, which may present with pulmonary or extrapulmonary disease. Patients, except those with COVID-19, should be tested for latent tuberculosis before TYENNE use and during therapy. Treatment for latent infection should be initiated prior to TYENNE use.
- Invasive fungal infections, including candidiasis, aspergillosis, and pneumocystis. Patients with invasive fungal infections may present with disseminated, rather than localized, disease.
- Bacterial, viral and other infections due to opportunistic pathogens.

The risks and benefits of treatment with TYENNE should be carefully considered prior to initiating therapy in patients with chronic or recurrent infection.

Patients should be closely monitored for the development of signs and symptoms of infection during and after treatment with TYENNE including the possible development of tuberculosis in patients who tested negative for latent tuberculosis infection prior to initiating therapy [see Warnings and Precautions (5.1)].

1 INDICATIONS AND USAGE

1.1 Rheumatoid Arthritis (RA)

TYENNE® (tocilizumab-aazg) is indicated for the treatment of adult patients with moderately to severely active rheumatoid arthritis who have had an inadequate response to one or more Disease-Modifying Anti-Rheumatic Drugs (DMARDs).

1.2 Giant Cell Arteritis (GCA)

TYENNE® (tocilizumab-aazg) is indicated for the treatment of giant cell arteritis (GCA) in adult patients.

1.3 Polyarticular Juvenile Idiopathic Arthritis (PJIA)

TYENNE® (tocilizumab-aazg) is indicated for the treatment of active polyarticular juvenile idiopathic arthritis in patients 2 years of age and older.

1.4 Systemic Juvenile Idiopathic Arthritis (SJIA)

TYENNE® (tocilizumab-aazg) is indicated for the treatment of active systemic juvenile idiopathic arthritis in patients 2 years of age and older.

1.5 Cytokine Release Syndrome (CRS)

TYENNE® (tocilizumab-aazg) is indicated for the treatment of chimeric antigen receptor (CAR) T cell-induced severe or life-threatening cytokine release syndrome in adults and pediatric patients 2 years of age and older.

1.6 Coronavirus Disease 2019 (COVID-19)

TYENNE® (tocilizumab-aazg) is indicated for the treatment of coronavirus disease 2019 (COVID-19) in hospitalized adult patients who are receiving systemic corticosteroids and require supplemental oxygen, noninvasive or invasive mechanical ventilation, or extracorporeal membrane oxygenation (ECMO).

2 DOSAGE AND ADMINISTRATION

2.1 General Considerations for Administration

Not Recommended for Concomitant Use with Biological DMARDs

Tocilizumab products have not been studied in combination with biological DMARDs such as TNF antagonists, IL-1R antagonists, anti-CD20 monoclonal antibodies and selective co-stimulation modulators because of the possibility of increased immunosuppression and increased risk of infection. Avoid using TYENNE with biological DMARDs.

Baseline Laboratory Evaluation Prior to Treatment

Obtain and assess baseline complete blood count (CBC) and liver function tests prior to treatment.

RA, GCA, PJIA and SJIA – It is recommended that TYENNE not be initiated in patients with an absolute neutrophil count (ANC) below 2,000 per mm^3, platelet count below 100,000 per mm^3, or ALT or AST above 1.5 times the upper limit of normal (ULN) [see Warnings and Precautions (5.3, 5.4)].

CRS – Patients with severe or life-threatening CRS frequently have cytopenias or elevated ALT or AST due to the lymphodepleting chemotherapy or the CRS. The decision to administer TYENNE should take into account the potential benefit of treating the CRS versus the risks of short-term treatment with TYENNE.

COVID-19 – It is recommended that TYENNE not be initiated in patients with an absolute neutrophil count (ANC) below 1,000 per mm^3, platelet count below 50,000 mm^3, or ALT or AST above 10 times ULN [see Warnings and Precautions (5.3, 5.4)].

2.2 Recommended Dosage for Rheumatoid Arthritis

TYENNE may be used as monotherapy or concomitantly with methotrexate or other non-biologic DMARDs as an intravenous infusion or as a subcutaneous injection.

Recommended Intravenous Dosage Regimen:

The recommended dosage of TYENNE for adult patients given as a 60-minute single intravenous drip infusion is 4 mg per kg every 4 weeks followed by an increase to 8 mg per kg every 4 weeks based on clinical response.

- Reduction of dose from 8 mg per kg to 4 mg per kg is recommended for management of certain dose-related laboratory changes including elevated liver enzymes, neutropenia, and thrombocytopenia [see Dosage and Administration (2.10), Warnings and Precautions (5.3, 5.4), and Adverse Reactions (6.1)].
- Doses exceeding 800 mg per infusion are not recommended in RA patients [see Clinical Pharmacology (12.3)].

Recommended Subcutaneous Dosage Regimen:

Patients less than 100 kg weight | 162 mg administered subcutaneously every other week, followed by an increase to every week based on clinical response
Patients at or above 100 kg weight | 162 mg administered subcutaneously every week

When transitioning from TYENNE intravenous therapy to subcutaneous administration administer the first subcutaneous dose instead of the next scheduled intravenous dose.

Interruption of dose or reduction in frequency of administration of subcutaneous dose from every week to every other week dosing is recommended for management of certain dose-related laboratory changes including elevated liver enzymes, neutropenia, and thrombocytopenia [see Dosage and Administration (2.10), Warnings and Precautions (5.3, 5.4), and Adverse Reactions (6.2)].

2.3 Recommended Dosage for Giant Cell Arteritis

Recommended Intravenous Dosage Regimen:

The recommended dosage of TYENNE for adult patients given as a 60-minute single intravenous drip infusion is 6 mg per kg every 4 weeks in combination with a tapering course of glucocorticoids.

TYENNE can be used alone following discontinuation of glucocorticoids.

- Interruption of dosing may be needed for management of dose-related laboratory abnormalities including elevated liver enzymes, neutropenia, and thrombocytopenia [see Dosage and Administration (2.10)].
- Doses exceeding 600 mg per infusion are not recommended in GCA patients [see Clinical Pharmacology (12.3)].

Recommended Subcutaneous Dosage Regimen:

The recommended dose of TYENNE for adult patients with GCA is 162 mg given once every week as a subcutaneous injection in combination with a tapering course of glucocorticoids.

A dose of 162 mg given once every other week as a subcutaneous injection in combination with a tapering course of glucocorticoids may be prescribed based on clinical considerations.

TYENNE can be used alone following discontinuation of glucocorticoids.

When transitioning from TYENNE intravenous therapy to subcutaneous administration, administer the first subcutaneous dose instead of the next scheduled intravenous dose.

Interruption of dose or reduction in frequency of administration of subcutaneous dose from every week to every other week dosing may be needed for management of dose-related laboratory abnormalities including elevated liver enzymes, neutropenia, and thrombocytopenia [see Dosage and Administration (2.10)].

2.4 Recommended Dosage for Polyarticular Juvenile Idiopathic Arthritis

TYENNE may be used as an intravenous infusion or as a subcutaneous injection alone or in combination with methotrexate. Do not change dose based solely on a single visit body weight measurement, as weight may fluctuate.

Recommended Intravenous Dosage Regimen:

The recommended dosage of TYENNE for PJIA patients given once every 4 weeks as a 60-minute single intravenous drip infusion is:

Recommended Intravenous PJIA Dosage Every 4 Weeks
Patients less than 30 kg weight | 10 mg per kg
Patients at or above 30 kg weight | 8 mg per kg

Recommended Subcutaneous Dosage Regimen:

Recommended Subcutaneous PJIA Dosage
Patients less than 30 kg weight | 162 mg once every 3 weeks
Patients at or above 30 kg weight | 162 mg once every 2 weeks

When transitioning from TYENNE intravenous therapy to subcutaneous administration, administer the first subcutaneous dose instead of the next scheduled intravenous dose.

Interruption of dosing may be needed for management of dose-related laboratory abnormalities including elevated liver enzymes, neutropenia, and thrombocytopenia [see Dosage and Administration (2.10)].

2.5 Recommended Dosage for Systemic Juvenile Idiopathic Arthritis

TYENNE may be used as an intravenous infusion or as a subcutaneous injection alone or in combination with methotrexate. Do not change a dose based solely on a single visit body weight measurement, as weight may fluctuate.

Recommended Intravenous Dosage Regimen:

The recommended dose of TYENNE for SJIA patients given once every 2 weeks as a 60-minute single intravenous drip infusion is:

Recommended Intravenous SJIA Dosage Every 2 Weeks
Patients less than 30 kg weight | 12 mg per kg
Patients at or above 30 kg weight | 8 mg per kg

Recommended Subcutaneous Dosage Regimen:

Recommended Subcutaneous SJIA Dosage
Patients less than 30 kg weight | 162 mg once every two weeks
Patients at or above 30 kg weight | 162 mg once every week

When transitioning from TYENNE intravenous therapy to subcutaneous administration, administer the first subcutaneous dose when the next scheduled intravenous dose is due.

Interruption of dosing may be needed for management of dose-related laboratory abnormalities including elevated liver enzymes, neutropenia, and thrombocytopenia [see Dosage and Administration (2.10)].

2.6 Recommended Dosage for Cytokine Release Syndrome (CRS)

Use only the intravenous route for treatment of CRS. The recommended dose of TYENNE for treatment of CRS given as a 60-minute intravenous infusion is:

Recommended Intravenous CRS Dosage
Patients less than 30 kg weight | 12 mg per kg
Patients at or above 30 kg weight | 8 mg per kg
Alone or in combination with corticosteroids

- If no clinical improvement in the signs and symptoms of CRS occurs after the first dose, up to 3 additional doses of TYENNE may be administered. The interval between consecutive doses should be at least 8 hours.
- Doses exceeding 800 mg per infusion are not recommended in CRS patients.
- Subcutaneous administration is not approved for CRS.

2.7 Coronavirus Disease 2019 (COVID-19)

Administer TYENNE by intravenous infusion only.

The recommended dosage of TYENNE for treatment of adult patients with COVID-19 is 8 mg per kg administered as a single 60-minute intravenous infusion. If clinical signs or symptoms worsen or do not improve after the first dose, one additional infusion of TYENNE may be administered at least 8 hours after the initial infusion.

- Doses exceeding 800 mg per infusion are not recommended in patients with COVID-19.
- Subcutaneous administration is not approved for COVID-19.

2.8 Preparation and Administration Instructions for Intravenous Infusion

TYENNE for intravenous infusion should be diluted by a healthcare professional using aseptic technique as follows:

- Use a sterile needle and syringe to prepare TYENNE.
- Patients less than 30 kg: use a 50 mL infusion bag or bottle of 0.9% or 0.45% Sodium Chloride Injection, USP, and then follow steps 1 and 2 below.
- Patients at or above 30 kg weight: use a 100 mL infusion bag or bottle, and then follow steps 1 and 2 below.
- Step 1. Withdraw a volume of 0.9% or 0.45% Sodium Chloride Injection, USP, equal to the volume of the TYENNE injection required for the patient's dose from the infusion bag or bottle [see Dosage and Administration (2.2, 2.4, 2.5, 2.6)].

For Intravenous Use: Volume of TYENNE Injection per kg of Body Weight
Dosage | Indication | Volume of TYENNE injection per kg of body weight
4 mg/kg | Adult RA | 0.2 mL/kg
6 mg/kg | Adult GCA | 0.3 mL/kg
8 mg/kg | Adult RA; Adult COVID-19; SJIA, PJIA and CRS (greater than or equal to 30 kg of body weight) | 0.4 mL/kg
10 mg/kg | PJIA (less than 30 kg of body weight) | 0.5 mL/kg
12 mg/kg | SJIA and CRS (less than 30 kg of body weight) | 0.6 mL/kg

- Step 2. Withdraw the amount of TYENNE for intravenous infusion from the vial(s) and add slowly into the 0.9% or 0.45% Sodium Chloride Injection, USP infusion bag or bottle. To mix the solution, gently invert the bag to avoid foaming.
- The prepared solution for infusion should be used immediately. If not used immediately, the diluted tocilizumab solutions may be refrigerated at 36°F to 46°F (2°C to 8°C) up to 24 hours, or stored at room temperature at or below 77°F (25°C) for up to 4 hours and should be protected from light. Administration of diluted TYENNE solution must be completed within this period of time.
- TYENNE solutions do not contain preservatives; therefore, unused product remaining in the vials should not be used.
- Allow the fully diluted TYENNE solution to reach room temperature prior to infusion.
- The infusion should be administered over 60 minutes and must be administered with an infusion set. Do not administer as an intravenous push or bolus.
- TYENNE should not be infused concomitantly in the same intravenous line with other drugs. No physical or biochemical compatibility studies have been conducted to evaluate the co-administration of TYENNE with other drugs.
- Parenteral drug products should be inspected visually for particulate matter and discoloration prior to administration, whenever solution and container permit. If particulates and discolorations are noted, the product should not be used.
- Fully diluted TYENNE solutions are compatible with polypropylene, polyethylene and polyvinyl chloride infusion bags and bottles, and glass infusion bottles.

2.9 Preparation and Administration Instructions for Subcutaneous Injection

- TYENNE for subcutaneous injection is not intended for intravenous drip infusion.
- Assess suitability of patient for subcutaneous home use and instruct patients to inform a healthcare professional before administering the next dose if they experience any symptoms of allergic reaction. Patients should seek immediate medical attention if they develop symptoms of serious allergic reactions. TYENNE subcutaneous injection is intended for use under the guidance of a healthcare practitioner. After proper training in subcutaneous injection technique, a patient may self-inject TYENNE or the patient's caregiver may administer TYENNE if a healthcare practitioner determines that it is appropriate. PJIA and SJIA patients may self-inject with the TYENNE prefilled syringe or autoinjector, or the patient's caregiver may administer TYENNE if both the healthcare practitioner and the parent/legal guardian determine it is appropriate [see Use in Specific Populations (8.4)].
  Patients, or patient caregivers, should be instructed to follow the directions provided in the Instructions for Use (IFU) for additional details on medication administration.
- Parenteral drug products should be inspected visually for particulate matter and discoloration prior to administration, whenever solution and container permit. Do not use TYENNE prefilled syringes (PFS) or prefilled autoinjectors exhibiting particulate matter, cloudiness, or discoloration. TYENNE for subcutaneous administration should be clear and colorless to pale yellow. Do not use if any part of the PFS or autoinjector appears to be damaged.
- Patients using TYENNE for subcutaneous administration should be instructed to inject the full amount in the syringe (0.9 mL) or full amount in the autoinjector (0.9 mL), which provides 162 mg of TYENNE, according to the directions provided in the IFU.
- Injection sites should be rotated with each injection and should never be given into moles, scars, or areas where the skin is tender, bruised, red, hard, or not intact.

2.10 Dosage Modifications due to Serious Infections or Laboratory Abnormalities

Serious Infections

Hold TYENNE treatment if a patient develops a serious infection until the infection is controlled.

Laboratory Abnormalities

Rheumatoid Arthritis and Giant Cell Arteritis

Liver Enzyme Abnormalities [see Warnings and Precautions (5.3, 5.4)]
Lab Value | Recommendation for RA | Recommendation for GCA
Greater than 1 to 3x ULN | Dose modify concomitant DMARDs if appropriate For persistent increases in this range:; - For patients receiving intravenous TYENNE, reduce dose to 4 mg per kg or hold TYENNE until ALT or AST have normalized - For patients receiving subcutaneous TYENNE, reduce injection frequency to every other week or hold dosing until ALT or AST have normalized. Resume TYENNE at every other week and increase frequency to every week as clinically appropriate | Dose modify immunomodulatory agents if appropriate For persistent increases in this range:; - For patients receiving Intravenous TYENNE, hold TYENNE until ALT or AST have normalized - For patients receiving subcutaneous TYENNE, reduce injection frequency to every other week or hold dosing until ALT or AST have normalized. Resume TYENNE at every other week and increase frequency to every week as clinically appropriate
Greater than 3 to 5x ULN (confirmed by repeat testing) | Hold TYENNE dosing until less than 3x ULN and follow recommendations above for greater than 1 to 3x ULN For persistent increases greater than 3x ULN, discontinue TYENNE | Hold TYENNE dosing until less than 3x ULN and follow recommendations above for greater than 1 to 3x ULN For persistent increases greater than 3x ULN, discontinue TYENNE
Greater than 5x ULN | Discontinue TYENNE | Discontinue TYENNE

Low Absolute Neutrophil Count (ANC) [see Warnings and Precautions (5.4)]
Lab Value (cells per mm^3) | Recommendation for RA | Recommendation for GCA
ANC greater than 1,000 | Maintain dose | Maintain dose
ANC 500 to 1,000 | Hold TYENNE dosing When ANC greater than 1,000 cells per mm^3:; - For patients receiving intravenous TYENNE, resume TYENNE at 4 mg per kg and increase to 8 mg per kg as clinically appropriate - For patients receiving subcutaneous TYENNE, resume TYENNE at every other week and increase frequency to every week as clinically appropriate | Hold TYENNE dosing When ANC greater than 1,000 cells per mm^3:; - For patients receiving intravenous TYENNE, resume TYENNE at 6 mg per kg - For patients receiving subcutaneous TYENNE, resume TYENNE at every other week and increase frequency to every week as clinically appropriate
ANC less than 500 | Discontinue TYENNE | Discontinue TYENNE

Low Platelet Count [see Warnings and Precautions (5.4)]
Lab Value (cells per mm^3) | Recommendation for RA | Recommendation for GCA
50,000 to 100,000 | Hold TYENNE dosing When platelet count is greater than 100,000 cells per mm^3:; - For patients receiving intravenous TYENNE, resume TYENNE at 4 mg per kg and increase to 8 mg per kg as clinically appropriate - For patients receiving subcutaneous TYENNE, resume TYENNE at every other week and increase frequency to every week as clinically appropriate | Hold TYENNE dosing When platelet count is greater than 100,000 cells per mm^3:; - For patients receiving intravenous TYENNE, resume TYENNE at 6 mg per kg - For patients receiving subcutaneous TYENNE, resume TYENNE at every other week and increase frequency to every week as clinically appropriate
Less than 50,000 | Discontinue TYENNE | Discontinue TYENNE

Polyarticular and Systemic Juvenile Idiopathic Arthritis

Dose reduction of tocilizumab products has not been studied in the PJIA and SJIA populations. Dose interruptions of TYENNE are recommended for liver enzyme abnormalities, low neutrophil counts, and low platelet counts in patients with PJIA and SJIA at levels similar to what is outlined above for patients with RA and GCA. If appropriate, dose modify or stop concomitant methotrexate and/or other medications and hold TYENNE dosing until the clinical situation has been evaluated. In PJIA and SJIA the decision to discontinue TYENNE for a laboratory abnormality should be based upon the medical assessment of the individual patient.

3 DOSAGE FORMS AND STRENGTHS

Intravenous Infusion

Injection: 80 mg/4 mL (20 mg/mL), 200 mg/10 mL (20 mg/mL), 400 mg/20 mL (20 mg/mL) as a clear and colorless to pale yellow solution in single-dose vials for further dilution prior to intravenous infusion.

Subcutaneous Injection

Injection: 162 mg/0.9 mL clear and colorless to pale yellow solution in a single-dose prefilled syringe or single-dose prefilled autoinjector.

4 CONTRAINDICATIONS

TYENNE is contraindicated in patients with known hypersensitivity to tocilizumab products [see Warnings and Precautions (5.6)].

5 WARNINGS AND PRECAUTIONS

5.1 Serious Infections

Serious and sometimes fatal infections due to bacterial, mycobacterial, invasive fungal, viral, protozoal, or other opportunistic pathogens have been reported in patients receiving immunosuppressive agents including tocilizumab products. The most common serious infections included pneumonia, urinary tract infection, cellulitis, herpes zoster, gastroenteritis, diverticulitis, sepsis and bacterial arthritis [see Adverse Reactions (6.1)]. Among opportunistic infections, tuberculosis, cryptococcus, aspergillosis, candidiasis, and pneumocystosis were reported with tocilizumab products. Other serious infections, not reported in clinical studies, may also occur (e.g., histoplasmosis, coccidioidomycosis, listeriosis). Patients have presented with disseminated rather than localized disease, and were often taking concomitant immunosuppressants such as methotrexate or corticosteroids which in addition to rheumatoid arthritis may predispose them to infections.

Do not administer TYENNE in patients with an active infection, including localized infections. The risks and benefits of treatment should be considered prior to initiating TYENNE in patients:

- with chronic or recurrent infection;
- who have been exposed to tuberculosis;
- with a history of serious or an opportunistic infection;
- who have resided or traveled in areas of endemic tuberculosis or endemic mycoses; or
- with underlying conditions that may predispose them to infection.

Closely monitor patients for the development of signs and symptoms of infection during and after treatment with TYENNE, as signs and symptoms of acute inflammation may be lessened due to suppression of the acute phase reactants [see Dosage and Administration (2.1), Adverse Reactions (6.1), and Patient Counseling Information (17)].

Hold TYENNE if a patient develops a serious infection, an opportunistic infection, or sepsis. A patient who develops a new infection during treatment with TYENNE should undergo a prompt and complete diagnostic workup appropriate for an immunocompromised patient, initiate appropriate antimicrobial therapy, and closely monitor the patient.

COVID-19

In patients with COVID-19, monitor for signs and symptoms of new infections during and after treatment with TYENNE. There is limited information regarding the use of tocilizumab products in patients with COVID-19 and concomitant active serious infections. The risks and benefits of treatment with TYENNE in COVID-19 patients with other concurrent infections should be considered.

Tuberculosis

Evaluate patients for tuberculosis risk factors and test for latent infection prior to initiating TYENNE. In patients with COVID-19, testing for latent infection is not necessary prior to initiating treatment with TYENNE.

Consider anti-tuberculosis therapy prior to initiation of TYENNE in patients with a past history of latent or active tuberculosis in whom an adequate course of treatment cannot be confirmed, and for patients with a negative test for latent tuberculosis but having risk factors for tuberculosis infection. Consultation with a physician with expertise in the treatment of tuberculosis is recommended to aid in the decision whether initiating anti-tuberculosis therapy is appropriate for an individual patient.

Closely monitor patients for the development of signs and symptoms of tuberculosis including patients who tested negative for latent tuberculosis infection prior to initiating therapy.

The incidence of tuberculosis in worldwide clinical development programs is 0.1%. Patients with latent tuberculosis should be treated with standard antimycobacterial therapy before initiating TYENNE.

Viral Reactivation

Viral reactivation has been reported with immunosuppressive biologic therapies and cases of herpes zoster exacerbation were observed in clinical studies with tocilizumab. No cases of Hepatitis B reactivation were observed in the trials; however patients who screened positive for hepatitis were excluded.

5.2 Gastrointestinal Perforations

Events of gastrointestinal perforation have been reported in clinical trials, primarily as complications of diverticulitis in patients treated with tocilizumab. Use TYENNE with caution in patients who may be at increased risk for gastrointestinal perforation. Promptly evaluate patients presenting with fever, new onset abdominal symptoms, and a change in bowel habits for early identification of gastrointestinal perforation [see Adverse Reactions (6.1)].

5.3 Hepatotoxicity

Serious cases of hepatic injury have been observed in patients taking intravenous or subcutaneous tocilizumab products. Some of these cases have resulted in liver transplant or death. Time to onset for cases ranged from months to years after treatment initiation with tocilizumab products. While most cases presented with marked elevations of transaminases (> 5 times ULN), some cases presented with signs or symptoms of liver dysfunction and only mildly elevated transaminases.

During randomized controlled studies, treatment with tocilizumab was associated with a higher incidence of transaminase elevations [see Adverse Reactions (6.1, 6.2, 6.5, 6.7)]. Increased frequency and magnitude of these elevations was observed when potentially hepatotoxic drugs (e.g., MTX) were used in combination with tocilizumab.

For RA and GCA patients, obtain a liver test panel (serum alanine aminotransferase [ALT], aspartate aminotransferase [AST], alkaline phosphatase, and total bilirubin) before initiating TYENNE, every 4 to 8 weeks after start of therapy for the first 6 months of treatment and every 3 months thereafter. It is not recommended to initiate TYENNE treatment in RA or GCA patients with elevated transaminases ALT or AST greater than 1.5x ULN. In patients who develop elevated ALT or AST greater than 5x ULN, discontinue TYENNE. For recommended modifications based upon increase in transaminases [see Dosage and Administration (2.10)].

Patients hospitalized with COVID-19 may have elevated ALT or AST levels. Multi-organ failure with involvement of the liver is recognized as a complication of severe COVID-19. The decision to administer TYENNE should balance the potential benefit of treating COVID-19 against the potential risks of acute treatment with TYENNE. It is not recommended to initiate TYENNE treatment in COVID-19 patients with elevated ALT or AST above 10 x ULN. Monitor ALT and AST during treatment.

Measure liver tests promptly in patients who report symptoms that may indicate liver injury, such as fatigue, anorexia, right upper abdominal discomfort, dark urine or jaundice. In this clinical context, if the patient is found to have abnormal liver tests (e.g., ALT greater than three times the upper limit of the reference range, serum total bilirubin greater than two times the upper limit of the reference range), TYENNE treatment should be interrupted and investigation done to establish the probable cause. TYENNE should only be restarted in patients with another explanation for the liver test abnormalities after normalization of the liver tests.

A similar pattern of liver enzyme elevation is noted with tocilizumab products treatment in the PJIA and SJIA populations. Monitor liver test panel at the time of the second administration and thereafter every 4 to 8 weeks for PJIA and every 2 to 4 weeks for SJIA.

5.4 Changes in Laboratory Parameters

Patients with Rheumatoid Arthritis, Giant Cell Arteritis and Coronavirus Disease 2019

Neutropenia

Treatment with tocilizumab products was associated with a higher incidence of neutropenia. Infections have been uncommonly reported in association with treatment-related neutropenia in long-term extension studies and postmarketing clinical experience.

- It is not recommended to initiate TYENNE treatment in RA and GCA patients with a low neutrophil count, i.e., absolute neutrophil count (ANC) less than 2000 per mm^3. In patients who develop an absolute neutrophil count less than 500 per mm^3 treatment is not recommended.
- Monitor neutrophils 4 to 8 weeks after start of therapy and every 3 months thereafter [see Clinical Pharmacology (12.2)]. For recommended modifications based on ANC results [ see Dosage and Administration (2.10)].
- It is not recommended to initiate TYENNE treatment in COVID-19 patients with an ANC less than 1000 per mm^3. Neutrophils should be monitored.

Thrombocytopenia

Treatment with tocilizumab products was associated with a reduction in platelet counts. Treatment-related reduction in platelets was not associated with serious bleeding events in clinical trials [see Adverse Reactions (6.1, 6.2)].

- It is not recommended to initiate TYENNE treatment in RA and GCA patients with a platelet count below 100,000 per mm^3. In patients who develop a platelet count less than 50,000 per mm^3 treatment is not recommended.
- Monitor platelets 4 to 8 weeks after start of therapy and every 3 months thereafter. For recommended modifications based on platelet counts [see Dosage and Administration (2.10)].
- In COVID-19 patients with a platelet count less than 50,000 per mm^3, treatment is not recommended. Platelets should be monitored.

Elevated Liver Enzymes

Refer to 5.3 Hepatotoxicity. For recommended modifications [see Dosage and Administration (2.10)].

Lipid Abnormalities

Treatment with tocilizumab products was associated with increases in lipid parameters such as total cholesterol, triglycerides, LDL cholesterol, and/or HDL cholesterol [see Adverse Reactions (6.1, 6.2)].

- Assess lipid parameters approximately 4 to 8 weeks following initiation of TYENNE therapy.
- Subsequently, manage patients according to clinical guidelines [e.g., National Cholesterol Educational Program (NCEP)] for the management of hyperlipidemia.

Patients with Polyarticular and Systemic Juvenile Idiopathic Arthritis

A similar pattern of liver enzyme elevation, low neutrophil count, low platelet count and lipid elevations is noted with tocilizumab products treatment in the PJIA and SJIA populations. Monitor neutrophils, platelets, ALT and AST at the time of the second administration and thereafter every 4 to 8 weeks for PJIA and every 2 to 4 weeks for SJIA. Monitor lipids as above for approved adult indications [see Dosage and Administration (2.10)].

5.5 Immunosuppression

The impact of treatment with tocilizumab products on the development of malignancies is not known but malignancies were observed in clinical studies [see Adverse Reactions (6.1)]. TYENNE is an immunosuppressant, and treatment with immunosuppressants may result in an increased risk of malignancies.

5.6 Hypersensitivity Reactions, Including Anaphylaxis

Hypersensitivity reactions, including anaphylaxis, have been reported in association with tocilizumab products and anaphylactic events with a fatal outcome have been reported with intravenous infusion of tocilizumab products. Anaphylaxis and other hypersensitivity reactions that required treatment discontinuation were reported in 0.1% (3 out of 2644) of patients in the 6-month controlled trials of intravenous tocilizumab, 0.2% (8 out of 4009) of patients in the intravenous all-exposure RA population, 0.7% (8 out of 1068) in the subcutaneous 6-month controlled RA trials, and in 0.7% (10 out of 1465) of patients in the subcutaneous all-exposure population. In the SJIA controlled trial with intravenous tocilizumab, 1 out of 112 patients (0.9%) experienced hypersensitivity reactions that required treatment discontinuation. In the PJIA controlled trial with intravenous tocilizumab, 0 out of 188 patients (0%) in the tocilizumab all-exposure population experienced hypersensitivity reactions that required treatment discontinuation. Reactions that required treatment discontinuation included generalized erythema, rash, and urticaria. Injection site reactions were categorized separately [see Adverse Reactions (6)].

In the postmarketing setting, events of hypersensitivity reactions, including anaphylaxis and death have occurred in patients treated with a range of doses of intravenous tocilizumab products, with or without concomitant therapies. Events have occurred in patients who received premedication. Hypersensitivity, including anaphylaxis events, have occurred both with and without previous hypersensitivity reactions and as early as the first infusion of tocilizumab products [see Adverse Reactions (6.11)]. In addition, serious cutaneous reactions, including Drug Reaction with Eosinophilia and Systemic Symptoms (DRESS), have been reported in patients with autoinflammatory conditions treated with tocilizumab products.

TYENNE for intravenous use should only be infused by a healthcare professional with appropriate medical support to manage anaphylaxis. For TYENNE subcutaneous injection, advise patients to seek immediate medical attention if they experience any symptoms of a hypersensitivity reaction. If a hypersensitivity reaction occurs, immediately discontinue TYENNE, treat promptly and monitor until signs and symptoms resolve.

5.7 Demyelinating Disorders

The impact of treatment with tocilizumab products on demyelinating disorders is not known, but multiple sclerosis and chronic inflammatory demyelinating polyneuropathy were reported rarely in RA clinical studies. Monitor patients for signs and symptoms potentially indicative of demyelinating disorders. Prescribers should exercise caution in considering the use of TYENNE in patients with preexisting or recent onset demyelinating disorders.

5.8 Active Hepatic Disease and Hepatic Impairment

Treatment with TYENNE is not recommended in patients with active hepatic disease or hepatic impairment [see Adverse Reactions (6.1), Use in Specific Populations (8.6)].

5.9 Vaccinations

Avoid use of live vaccines concurrently with TYENNE as clinical safety has not been established. No data are available on the secondary transmission of infection from persons receiving live vaccines to patients receiving tocilizumab products.

No data are available on the effectiveness of vaccination in patients receiving tocilizumab products. Because IL-6 inhibition may interfere with the normal immune response to new antigens, it is recommended that all patients, particularly pediatric or elderly patients, if possible, be brought up to date with all immunizations in agreement with current immunization guidelines prior to initiating TYENNE therapy. The interval between live vaccinations and initiation of TYENNE therapy should be in accordance with current vaccination guidelines regarding immunosuppressive agents.

6 ADVERSE REACTIONS

The following serious adverse reactions are described elsewhere in labeling:

- Serious Infections [see Warnings and Precautions (5.1)]
- Gastrointestinal Perforations [see Warnings and Precautions (5.2)]
- Laboratory Parameters [see Warnings and Precautions (5.4)]
- Immunosuppression [see Warnings and Precautions (5.5)]
- Hypersensitivity Reactions, Including Anaphylaxis [see Warnings and Precautions (5.6)]
- Demyelinating Disorders [see Warnings and Precautions (5.7)]
- Active Hepatic Disease and Hepatic Impairment [see Warnings and Precautions (5.8)]

Because clinical studies are conducted under widely varying conditions, adverse reaction rates observed in the clinical studies of a drug cannot be directly compared to rates in the clinical studies of another drug and may not predict the rates observed in a broader patient population in clinical practice.

6.1 Clinical Trials Experience in Rheumatoid Arthritis Patients Treated with Intravenous Tocilizumab (tocilizumab-IV)

The tocilizumab-IV data in rheumatoid arthritis (RA) includes 5 double-blind, controlled, multicenter studies. In these studies, patients received doses of tocilizumab-IV 8 mg per kg monotherapy (288 patients), tocilizumab-IV 8 mg per kg in combination with DMARDs (including methotrexate) (1582 patients), or tocilizumab-IV 4 mg per kg in combination with methotrexate (774 patients).

The all exposure population includes all patients in registration studies who received at least one dose of tocilizumab-IV. Of the 4009 patients in this population, 3577 received treatment for at least 6 months, 3309 for at least one year; 2954 received treatment for at least 2 years and 2189 for 3 years.

All patients in these studies had moderately to severely active rheumatoid arthritis. The study population had a mean age of 52 years, 82% were female and 74% were Caucasian.

The most common serious adverse reactions were serious infections [see Warnings and Precautions (5.1)]. The most commonly reported adverse reactions in controlled studies up to 24 weeks (occurring in at least 5% of patients treated with tocilizumab-IV monotherapy or in combination with DMARDs) were upper respiratory tract infections, nasopharyngitis, headache, hypertension and increased ALT.

The proportion of patients who discontinued treatment due to any adverse reactions during the double-blind, placebo-controlled studies was 5% for patients taking tocilizumab-IV and 3% for placebo-treated patients. The most common adverse reactions that required discontinuation of tocilizumab-IV were increased hepatic transaminase values (per protocol requirement) and serious infections.

Overall Infections

In the 24 week, controlled clinical studies, the rate of infections in the tocilizumab-IV monotherapy group was 119 events per 100 patient-years and was similar in the methotrexate monotherapy group. The rate of infections in the 4 mg per kg and 8 mg per kg tocilizumab-IV plus DMARD group was 133 and 127 events per 100 patient-years, respectively, compared to 112 events per 100 patient-years in the placebo plus DMARD group. The most commonly reported infections (5% to 8% of patients) were upper respiratory tract infections and nasopharyngitis.

The overall rate of infections with tocilizumab-IV in the all exposure population remained consistent with rates in the controlled periods of the studies.

Serious Infections

In the 24 week, controlled clinical studies, the rate of serious infections in the tocilizumab-IV monotherapy group was 3.6 per 100 patient-years compared to 1.5 per 100 patient-years in the methotrexate group. The rate of serious infections in the 4 mg per kg and 8 mg per kg tocilizumab-IV plus DMARD group was 4.4 and 5.3 events per 100 patient-years, respectively, compared to 3.9 events per 100 patient-years in the placebo plus DMARD group.

In the all-exposure population, the overall rate of serious infections remained consistent with rates in the controlled periods of the studies. The most common serious infections included pneumonia, urinary tract infection, cellulitis, herpes zoster, gastroenteritis, diverticulitis, sepsis and bacterial arthritis. Cases of opportunistic infections have been reported [see Warnings and Precautions (5.1)].

In the cardiovascular outcomes Study WA25204, the rate of serious infections in the tocilizumab 8 mg/kg IV every 4 weeks group, with or without DMARD, was 4.5 per 100 patient-years, and the rate in the etanercept 50 mg weekly SC group, with or without DMARD, was 3.2 per 100 patient-years [see Clinical Studies (14.1)].

Gastrointestinal Perforations

During the 24 week, controlled clinical trials, the overall rate of gastrointestinal perforation was 0.26 events per 100 patient-years with tocilizumab-IV therapy.

In the all-exposure population, the overall rate of gastrointestinal perforation remained consistent with rates in the controlled periods of the studies. Reports of gastrointestinal perforation were primarily reported as complications of diverticulitis including generalized purulent peritonitis, lower GI perforation, fistula and abscess. Most patients who developed gastrointestinal perforations were taking concomitant nonsteroidal anti-inflammatory medications (NSAIDs), corticosteroids, or methotrexate [see Warnings and Precautions (5.2)]. The relative contribution of these concomitant medications versus tocilizumab-IV to the development of GI perforations is not known.

Infusion Reactions

In the 24 week, controlled clinical studies, adverse events associated with the infusion (occurring during or within 24 hours of the start of infusion) were reported in 8% and 7% of patients in the 4 mg per kg and 8 mg per kg tocilizumab-IV plus DMARD group, respectively, compared to 5% of patients in the placebo plus DMARD group. The most frequently reported event on the 4 mg per kg and 8 mg per kg dose during the infusion was hypertension (1% for both doses), while the most frequently reported event occurring within 24 hours of finishing an infusion were headache (1% for both doses) and skin reactions (1% for both doses), including rash, pruritus and urticaria. These events were not treatment limiting.

Anaphylaxis

Hypersensitivity reactions requiring treatment discontinuation, including anaphylaxis, associated with tocilizumab-IV were reported in 0.1% (3 out of 2644) in the 24 week, controlled trials and in 0.2% (8 out of 4009) in the all-exposure population. These reactions were generally observed during the second to fourth infusion of tocilizumab-IV. Appropriate medical treatment should be available for immediate use in the event of a serious hypersensitivity reaction [see Warnings and Precautions 5.6)].

Laboratory Abnormalities

Neutropenia

In the 24 week, controlled clinical studies, decreases in neutrophil counts below 1000 per mm^3 occurred in 1.8% and 3.4% of patients in the 4 mg per kg and 8 mg per kg tocilizumab-IV plus DMARD group, respectively, compared to 0.1% of patients in the placebo plus DMARD group.

Approximately half of the instances of ANC below 1000 per mm^3 occurred within 8 weeks of starting therapy. Decreases in neutrophil counts below 500 per mm^3 occurred in 0.4% and 0.3% of patients in the 4 mg per kg and 8 mg per kg tocilizumab-IV plus DMARD, respectively, compared to 0.1% of patients in the placebo plus DMARD group. There was no clear relationship between decreases in neutrophils below 1000 per mm^3 and the occurrence of serious infections.

In the all-exposure population, the pattern and incidence of decreases in neutrophil counts remained consistent with what was seen in the 24 week controlled clinical studies [see Warnings and Precautions (5.4)].

Thrombocytopenia

In the 24 week, controlled clinical studies, decreases in platelet counts below 100,000 per mm^3 occurred in 1.3% and 1.7% of patients on 4 mg per kg and 8 mg per kg tocilizumab-IV plus DMARD, respectively, compared to 0.5% of patients on placebo plus DMARD, without associated bleeding events.

In the all-exposure population, the pattern and incidence of decreases in platelet counts remained consistent with what was seen in the 24 week controlled clinical studies [see Warnings and Precautions 5.4)].

Elevated Liver Enzymes

Liver enzyme abnormalities are summarized in Table 1. In patients experiencing liver enzyme elevation, modification of treatment regimen, such as reduction in the dose of concomitant DMARD, interruption of tocilizumab-IV, or reduction in tocilizumab-IV dose, resulted in decrease or normalization of liver enzymes [see Dosage and Administration (2.1)]. These elevations were not associated with clinically relevant increases in direct bilirubin, nor were they associated with clinical evidence of hepatitis or hepatic insufficiency [see Warnings and Precautions (5.3, 5.4)].

Table 1 Incidence of Liver Enzyme Abnormalities in the 24 Week Controlled Period of Studies I to V*
 | Tocilizumab 8 mg per kg MONOTHERAPY | Methotrexate | Tocilizumab 4 mg per kg + DMARDs | Tocilizumab 8 mg per kg + DMARDs | Placebo + DMARDs
 | N = 288 | N = 284 | N = 774 | N = 1582 | N = 1170
 | (%) | (%) | (%) | (%) | (%)
AST (U/L)
> ULN to 3x ULN | 22 | 26 | 34 | 41 | 17
> 3x ULN to 5x ULN | 0.3 | 2 | 1 | 2 | 0.3
> 5x ULN | 0.7 | 0.4 | 0.1 | 0.2 | < 0.1
ALT (U/L)
> ULN to 3x ULN | 36 | 33 | 45 | 48 | 23
> 3x ULN to 5x ULN | 1 | 4 | 5 | 5 | 1
> 5x ULN | 0.7 | 1 | 1.3 | 1.5 | 0.3
ULN = Upper Limit of Normal
*For a description of these studies, see Section 14, Clinical Studies.

In the all-exposure population, the elevations in ALT and AST remained consistent with what was seen in the 24 week, controlled clinical trials.

In Study WA25204, of the 1538 patients with moderate to severe RA [see Clinical Studies (14.1)] and treated with tocilizumab, elevations in ALT or AST >3 x ULN occurred in 5.3% and 2.2% patients, respectively. One serious event of drug induced hepatitis with hyperbilirubinemia was reported in association with tocilizumab.

Lipids

Elevations in lipid parameters (total cholesterol, LDL, HDL, triglycerides) were first assessed at 6 weeks following initiation of tocilizumab-IV in the controlled 24 week clinical trials.

Increases were observed at this time point and remained stable thereafter. Increases in triglycerides to levels above 500 mg per dL were rarely observed. Changes in other lipid parameters from baseline to week 24 were evaluated and are summarized below:

- Mean LDL increased by 13 mg per dL in the tocilizumab 4 mg per kg+DMARD arm, 20 mg per dL in the tocilizumab 8 mg per kg+DMARD, and 25 mg per dL in tocilizumab 8 mg per kg monotherapy.
- Mean HDL increased by 3 mg per dL in the tocilizumab 4 mg per kg+DMARD arm, 5 mg per dL in the tocilizumab 8 mg per kg+DMARD, and 4 mg per dL in tocilizumab 8 mg per kg monotherapy.
- Mean LDL/HDL ratio increased by an average of 0.14 in the tocilizumab 4 mg per kg+DMARD arm, 0.15 in the tocilizumab 8 mg per kg+DMARD, and 0.26 in tocilizumab 8 mg per kg monotherapy.
- ApoB/ApoA1 ratios were essentially unchanged in tocilizumab-treated patients.
- Elevated lipids responded to lipid lowering agents.

In the all-exposure population, the elevations in lipid parameters remained consistent with what was seen in the 24 week, controlled clinical trials.

Immunogenicity

The observed incidence of anti-drug antibodies is highly dependent on the sensitivity and specificity of the assay. Differences in assay methods preclude meaningful comparisons of the incidence of anti-drug antibodies in the studies described below with the incidence of anti-drug antibodies in other studies, including those of tocilizumab or of other tocilizumab products.

In the 24 week, controlled clinical studies, a total of 2876 patients have been tested for anti-tocilizumab antibodies. Forty-six patients (2%) developed positive anti-tocilizumab antibodies, of whom 5 had an associated, medically significant, hypersensitivity reaction leading to withdrawal. Thirty patients (1%) developed neutralizing antibodies.

Malignancies

During the 24 week, controlled period of the studies, 15 malignancies were diagnosed in patients receiving tocilizumab-IV, compared to 8 malignancies in patients in the control groups. Exposure-adjusted incidence was similar in the tocilizumab-IV groups (1.32 events per 100 patient-years) and in the placebo plus DMARD group (1.37 events per 100 patient-years).

In the all-exposure population, the rate of malignancies remained consistent with the rate observed in the 24 week, controlled period [see Warnings and Precautions (5.5)].

Other Adverse Reactions

Adverse reactions occurring in 2% or more of patients on 4 or 8 mg per kg tocilizumab-IV plus DMARD and at least 1% greater than that observed in patients on placebo plus DMARD are summarized inTable 2.

Table 2 Adverse Reactions Occurring in at Least 2% or More of Patients on 4 or 8 mg per kg Tocilizumab plus DMARD and at Least 1% Greater Than That Observed in Patients on Placebo plus DMARD
24 Week Phase 3 Controlled Study Population
 | Tocilizumab 8 mg per kg MONOTHERAPY | Methotrexate | Tocilizumab 4 mg per kg + DMARDs | Tocilizumab 8 mg per kg + DMARDs | Placebo + DMARDs
Preferred Term | N = 288 | N = 284 | N = 774 | N = 1582 | N = 1170
 | (%) | (%) | (%) | (%) | (%)
Upper Respiratory Tract Infection | 7 | 5 | 6 | 8 | 6
Nasopharyngitis | 7 | 6 | 4 | 6 | 4
Headache | 7 | 2 | 6 | 5 | 3
Hypertension | 6 | 2 | 4 | 4 | 3
ALT increased | 6 | 4 | 3 | 3 | 1
Dizziness | 3 | 1 | 2 | 3 | 2
Bronchitis | 3 | 2 | 4 | 3 | 3
Rash | 2 | 1 | 4 | 3 | 1
Mouth Ulceration | 2 | 2 | 1 | 2 | 1
Abdominal Pain Upper | 2 | 2 | 3 | 3 | 2
Gastritis | 1 | 2 | 1 | 2 | 1
Transaminase increased | 1 | 5 | 2 | 2 | 1

Other infrequent and medically relevant adverse reactions occurring at an incidence less than 2% in rheumatoid arthritis patients treated with tocilizumab-IV in controlled trials were:

Infections and Infestations: oral herpes simplex

Gastrointestinal disorders: stomatitis, gastric ulcer

Investigations: weight increased, total bilirubin increased

Blood and lymphatic system disorders: leukopenia

General disorders and administration site conditions: edema peripheral

Respiratory, thoracic, and mediastinal disorders: dyspnea, cough

Eye disorders: conjunctivitis

Renal disorders: nephrolithiasis

Endocrine disorders: hypothyroidism

6.2 Clinical Trials Experience in Rheumatoid Arthritis Patients Treated with Subcutaneous Tocilizumab (tocilizumab-SC)

The tocilizumab-SC data in rheumatoid arthritis (RA) includes 2 double-blind, controlled, multicenter studies. Study SC-I was a non-inferiority study that compared the efficacy and safety of tocilizumab 162 mg administered every week subcutaneously and 8 mg/kg intravenously every four weeks in 1262 adult subjects with rheumatoid arthritis. Study SC-II was a placebo-controlled superiority study that evaluated the safety and efficacy of tocilizumab 162 mg administered every other week subcutaneously or placebo in 656 patients. All patients in both studies received background non-biologic DMARDs.

The safety observed for tocilizumab-SC administered subcutaneously was consistent with the known safety profile of intravenous tocilizumab, with the exception of injection site reactions (ISRs), which were more common with tocilizumab-SC compared with placebo SC injections (IV arm).

Injection Site Reactions

In the 6-month control period, in SC-I, the frequency of ISRs was 10.1% (64/631) and 2.4% (15/631) for the weekly tocilizumab-SC and placebo SC (IV-arm) groups, respectively. In SC-II, the frequency of ISRs was 7.1% (31/437) and 4.1% (9/218) for the every other week tocilizumab-SC and placebo groups, respectively. These ISRs (including erythema, pruritus, pain and hematoma) were mild to moderate in severity. The majority resolved without any treatment and none necessitated drug discontinuation.

Immunogenicity

In the 6-month control period in SC-I, 0.8% (5/625) in the tocilizumab-SC arm and 0.8% (5/627) in the IV arm developed anti-tocilizumab antibodies; of these, all developed neutralizing antibodies. In SC-II, 1.6% (7/434) in the tocilizumab-SC arm compared with 1.4 % (3/217) in the placebo arm developed anti-tocilizumab antibodies; of these, 1.4% (6/434) in the tocilizumab-SC arm and 0.5% (1/217) in the placebo arm also developed neutralizing antibodies.

A total of 1454 (>99%) patients who received tocilizumab-SC in the all exposure group have been tested for anti- tocilizumab antibodies. Thirteen patients (0.9%) developed anti-tocilizumab antibodies, and, of these, 12 patients (0.8%) developed neutralizing antibodies.

The rate is consistent with previous intravenous experience. No correlation of antibody development to adverse events or loss of clinical response was observed.

Laboratory Abnormalities

Neutropenia

During routine laboratory monitoring in the 6-month controlled clinical trials, a decrease in neutrophil count below 1 × 10^9/L occurred in 2.9% and 3.7% of patients receiving tocilizumab-SC weekly and every other week, respectively.

There was no clear relationship between decreases in neutrophils below 1 x 10^9/L and the occurrence of serious infections.

Thrombocytopenia

During routine laboratory monitoring in the tocilizumab-SC 6-month controlled clinical trials, none of the patients had a decrease in platelet count to ≤ 50,000/mm^3.

Elevated Liver Enzymes

During routine laboratory monitoring in the 6-month controlled clinical trials, elevation in ALT or AST ≥3 x ULN occurred in 6.5% and 1.4% of patients, respectively, receiving tocilizumab-SC weekly and 3.4% and 0.7% receiving tocilizumab-SC every other week.

Lipid Parameters Elevations

During routine laboratory monitoring in the tocilizumab-SC 6-month clinical trials, 19% of patients dosed weekly and 19.6% of patients dosed every other week and 10.2% of patients on placebo experienced sustained elevations in total cholesterol > 6.2 mmol/l (240 mg/dL), with 9%, 10.4% and 5.1% experiencing a sustained increase in LDL to 4.1 mmol/l (160 mg/dL) receiving tocilizumab-SC weekly, every other week and placebo, respectively.

6.3 Clinical Trials Experience in Giant Cell Arteritis Patients Treated with Subcutaneous Tocilizumab (tocilizumab-SC)

The safety of subcutaneous tocilizumab has been studied in one Phase III study (WA28119) with 251 GCA patients. The total patient years duration in the tocilizumab-SC GCA all exposure population was 138.5 patient years during the 12-month double blind, placebo-controlled phase of the study. The overall safety profile observed in the tocilizumab-SC treatment groups was generally consistent with the known safety profile of tocilizumab. There was an overall higher incidence of infections in GCA patients relative to RA patients.

The rate of infection/serious infection events was 200.2/9.7 events per 100 patient years in the tocilizumab-SC weekly group and 160.2/4.4 events per 100 patient years in the tocilizumab-SC every other week group as compared to 156.0/4.2 events per 100 patient years in the placebo + 26 week prednisone taper and 210.2/12.5 events per 100 patient years in the placebo + 52 week taper groups.

6.4 Clinical Trials Experience in Giant Cell Arteritis Patients Treated With Intravenous Tocilizumab (tocilizumab-IV)

The safety of tocilizumab-IV was studied in an open label PK-PD and safety study in 24 patients with GCA who were in remission on tocilizumab-IV at time of enrollment. Patients received tocilizumab 7 mg/kg every 4 weeks for 20 weeks, followed by 6 mg/kg every 4 weeks for 20 weeks. The total patient years exposure to treatment was 17.5 years. The overall safety profile observed for tocilizumab administered intravenously in GCA patients was consistent with the known safety profile of tocilizumab.

6.5 Clinical Trials Experience in Polyarticular Juvenile Idiopathic Arthritis Patients Treated With Intravenous Tocilizumab (tocilizumab-IV)

The safety of tocilizumab-IV was studied in 188 pediatric patients 2 to 17 years of age with PJIA who had an inadequate clinical response or were intolerant to methotrexate. The total patient exposure in the tocilizumab-IV all exposure population (defined as patients who received at least one dose of tocilizumab-IV) was 184.4 patient years. At baseline, approximately half of the patients were taking oral corticosteroids and almost 80% were taking methotrexate. In general, the types of adverse drug reactions in patients with PJIA were consistent with those seen in RA and SJIA patients [see Adverse Reactions (6.1 and 6.7)].

Infections

The rate of infections in the tocilizumab-IV all exposure population was 163.7 per 100 patient years. The most common events observed were nasopharyngitis and upper respiratory tract infections. The rate of serious infections was numerically higher in patients weighing less than 30 kg treated with 10 mg/kg tocilizumab (12.2 per 100 patient years) compared to patients weighing at or above 30 kg, treated with 8 mg/kg tocilizumab (4.0 per 100 patient years).

The incidence of infections leading to dose interruptions was also numerically higher in patients weighing less than 30 kg treated with 10 mg/kg tocilizumab (21%) compared to patients weighing at or above 30 kg, treated with 8 mg/kg tocilizumab (8%).

Infusion Reactions

In PJIA patients, infusion-related reactions are defined as all events occurring during or within 24 hours of an infusion. In the tocilizumab-IV all exposure population, 11 patients (6%) experienced an event during the infusion, and 38 patients (20.2%) experienced an event within 24 hours of an infusion. The most common events occurring during infusion were headache, nausea and hypotension, and occurring within 24 hours of infusion were dizziness and hypotension. In general, the adverse drug reactions observed during or within 24 hours of an infusion were similar in nature to those seen in RA and SJIA patients [see Adverse Reactions (6.1 and 6.7)].

No clinically significant hypersensitivity reactions associated with tocilizumab and requiring treatment discontinuation were reported.

Immunogenicity

One patient, in the 10 mg/kg less than 30 kg group, developed positive anti-tocilizumab antibodies without developing a hypersensitivity reaction and subsequently withdrew from the study.

Laboratory Abnormalities

Neutropenia

During routine laboratory monitoring in the tocilizumab-IV all exposure population, a decrease in neutrophil counts below 1 × 10^9 per L occurred in 3.7% of patients.

There was no clear relationship between decreases in neutrophils below 1 x 10^9 per L and the occurrence of serious infections.

Thrombocytopenia

During routine laboratory monitoring in the tocilizumab-IV all exposure population, 1% of patients had a decrease in platelet count at or less than 50,000 per mm^3 without associated bleeding events.

Elevated Liver Enzymes

During routine laboratory monitoring in the tocilizumab-IV all exposure population, elevation in ALT or AST at or greater than 3 x ULN occurred in 4% and less than 1% of patients, respectively.

Lipids

During routine laboratory monitoring in the tocilizumab all exposure population, elevation in total cholesterol greater than 1.5-2 x ULN occurred in one patient (0.5%) and elevation in LDL greater than 1.5-2 x ULN occurred in one patient (0.5%).

6.6 Clinical Trials Experience in Polyarticular Juvenile Idiopathic Arthritis Patients Treated With Subcutaneous Tocilizumab (tocilizumab-SC)

The safety of tocilizumab-SC was studied in 52 pediatric patients 1 to 17 years of age with PJIA who had an inadequate clinical response or were intolerant to methotrexate. The total patient exposure in the PJIA tocilizumab-SC population (defined as patients who received at least one dose of tocilizumab-SC and accounting for treatment discontinuation) was 49.5 patient years.

In general, the safety observed for tocilizumab administered subcutaneously was consistent with the known safety profile of intravenous tocilizumab, with the exception of injection site reactions (ISRs), and neutropenia.

Injection Site Reactions

During the 1-year study, a frequency of 28.8% (15/52) ISRs was observed in tocilizumab-SC treated PJIA patients. These ISRs occurred in a greater proportion of patients at or above 30 kg (44.0%) compared with patients below 30 kg (14.8%). All ISRs were mild in severity and none of the ISRs required patient withdrawal from treatment or dose interruption. A higher frequency of ISRs was observed in tocilizumab-SC treated PJIA patients compared to what was seen in adult RA or GCA patients [see Adverse Reactions (6.2 and 6.3)].

Immunogenicity

Three patients, 1 patient below 30 kg and 2 patients at or above 30 kg, developed positive anti-tocilizumab antibodies with neutralizing potential without developing a serious or clinically significant hypersensitivity reaction. One patient subsequently withdrew from the study.

Neutropenia

During routine laboratory monitoring in the tocilizumab-SC all exposure population, a decrease in neutrophil counts below 1 × 10^9 per L occurred in 15.4% of patients, and was more frequently observed in the patients less than 30 kg (25.9%) compared to patients at or above 30 kg (4.0%). There was no clear relationship between decreases in neutrophils below 1 x 10^9 per L and the occurrence of serious infections.

6.7 Clinical Trials Experience in Systemic Juvenile Idiopathic Arthritis Patients Treated with Intravenous Tocilizumab (tocilizumab-IV)

The data described below reflect exposure to tocilizumab-IV in one randomized, double-blind, placebo-controlled trial of 112 pediatric patients with SJIA 2 to 17 years of age who had an inadequate clinical response to nonsteroidal anti-inflammatory drugs (NSAIDs) or corticosteroids due to toxicity or lack of efficacy. At baseline, approximately half of the patients were taking 0.3 mg/kg/day corticosteroids or more, and almost 70% were taking methotrexate. The trial included a 12 week controlled phase followed by an open-label extension. In the 12 week double-blind, controlled portion of the clinical study 75 patients received treatment with tocilizumab-IV (8 or 12 mg per kg based upon body weight). After 12 weeks or at the time of escape, due to disease worsening, patients were treated with tocilizumab-IV in the open-label extension phase.

The most common adverse events (at least 5%) seen in tocilizumab-IV treated patients in the 12 week controlled portion of the study were: upper respiratory tract infection, headache, nasopharyngitis and diarrhea.

Infections

In the 12 week controlled phase, the rate of all infections in the tocilizumab-IV group was 345 per 100 patient-years and 287 per 100 patient-years in the placebo group. In the open label extension over an average duration of 73 weeks of treatment, the overall rate of infections was 304 per 100 patient-years.

In the 12 week controlled phase, the rate of serious infections in the tocilizumab-IV group was 11.5 per 100 patient years. In the open label extension over an average duration of 73 weeks of treatment, the overall rate of serious infections was 11.4 per 100 patient years. The most commonly reported serious infections included pneumonia, gastroenteritis, varicella, and otitis media.

Macrophage Activation Syndrome

In the 12 week controlled study, no patient in any treatment group experienced macrophage activation syndrome (MAS) while on assigned treatment; 3 per 112 (3%) developed MAS during open-label treatment with tocilizumab-IV. One patient in the placebo group escaped to tocilizumab-IV 12 mg per kg at Week 2 due to severe disease activity, and ultimately developed MAS at Day 70. Two additional patients developed MAS during the long-term extension. All 3 patients had tocilizumab-IV dose interrupted (2 patients) or discontinued (1 patient) for the MAS event, received treatment, and the MAS resolved without sequelae. Based on a limited number of cases, the incidence of MAS does not appear to be elevated in the tocilizumab-IV SJIA clinical development experience; however no definitive conclusions can be made.

Infusion Reactions

Patients were not premedicated, however most patients were on concomitant corticosteroids as part of their background treatment for SJIA. Infusion related reactions were defined as all events occurring during or within 24 hours after an infusion. In the 12 week controlled phase, 4% of tocilizumab-IV and 0% of placebo treated patients experienced events occurring during infusion. One event (angioedema) was considered serious and life-threatening, and the patient was discontinued from study treatment.

Within 24 hours after infusion, 16% of patients in the tocilizumab-IV treatment group and 5% of patients in the placebo group experienced an event. In the tocilizumab-IV group the events included rash, urticaria, diarrhea, epigastric discomfort, arthralgia and headache. One of these events, urticaria, was considered serious.

Anaphylaxis

Anaphylaxis was reported in 1 out of 112 patients (less than 1%) treated with tocilizumab-IV during the controlled and open label extension study [see Warnings and Precautions (5.6)].

Immunogenicity

All 112 patients were tested for anti-tocilizumab antibodies at baseline. Two patients developed positive anti- tocilizumab antibodies: one of these patients experienced serious adverse events of urticaria and angioedema consistent with an anaphylactic reaction which led to withdrawal; the other patient developed macrophage activation syndrome while on escape therapy and was discontinued from the study.

Laboratory Abnormalities

Neutropenia

During routine monitoring in the 12 week controlled phase, a decrease in neutrophil below 1 × 10^9 per L occurred in 7% of patients in the tocilizumab-IV group, and in no patients in the placebo group. In the open label extension over an average duration of 73 weeks of treatment, a decreased neutrophil count occurred in 17% of the tocilizumab-IV group. There was no clear relationship between decrease in neutrophils below 1 x 10^9 per L and the occurrence of serious infections.

Thrombocytopenia

During routine monitoring in the 12 week controlled phase, 1% of patients in the tocilizumab-IV group and 3% in the placebo group had a decrease in platelet count to no more than 100,000 per mm^3.

In the open label extension over an average duration of 73 weeks of treatment, decreased platelet count occurred in 4% of patients in the tocilizumab-IV group, with no associated bleeding.

Elevated Liver Enzymes

During routine laboratory monitoring in the 12 week controlled phase, elevation in ALT or AST at or above 3x ULN occurred in 5% and 3% of patients, respectively in the tocilizumab-IV group and in 0% of placebo patients.

In the open label extension over an average duration of 73 weeks of treatment, the elevation in ALT or AST at or above 3x ULN occurred in 13% and 5% of tocilizumab-IV treated patients, respectively.

Lipids

During routine laboratory monitoring in the 12 week controlled phase, elevation in total cholesterol greater than 1.5x ULN – 2x ULN occurred in 1.5% of the tocilizumab-IV group and in 0% of placebo patients. Elevation in LDL greater than 1.5x ULN – 2x ULN occurred in 1.9% of patients in the tocilizumab-IV group and 0% of the placebo group.

In the open label extension study over an average duration of 73 weeks of treatment, the pattern and incidence of elevations in lipid parameters remained consistent with the 12 week controlled study data.

6.8 Clinical Trials Experience in Systemic Juvenile Idiopathic Arthritis Patients Treated with Subcutaneous Tocilizumab (tocilizumab-SC)

The safety profile of tocilizumab-SC was studied in 51 pediatric patients 1 to 17 years of age with SJIA who had an inadequate clinical response to NSAIDs and corticosteroids. In general, the safety observed for tocilizumab administered subcutaneously was consistent with the known safety profile of intravenous tocilizumab, with the exception of ISRs where a higher frequency was observed in tocilizumab-SC treated SJIA patients compared to PJIA patients and adult RA or GCA patients [see Adverse Reactions (6.2, 6.3 and 6.6)].

Injection Site Reactions (ISRs)

A total of 41.2% (21/51) SJIA patients experienced ISRs to tocilizumab-SC. The most common ISRs were erythema, pruritus, pain, and swelling at the injection site. The majority of ISRs reported were Grade 1 events and all ISRs reported were non-serious and none required patient withdrawal from treatment or dose interruption.

Immunogenicity

Forty-six of the 51 (90.2%) patients who were tested for anti-tocilizumab antibodies at baseline had at least one post-baseline screening assay result. No patient developed positive anti-tocilizumab antibodies post-baseline.

6.9 Clinical Trials Experience in Patients with Cytokine Release Syndrome Treated with Intravenous Tocilizumab (tocilizumab-IV)

In a retrospective analysis of pooled outcome data from multiple clinical trials 45 patients were treated with tocilizumab 8 mg/kg (12 mg/kg for patients less than 30 kg) with or without additional high-dose corticosteroids for severe or life-threatening CAR T-cell-induced CRS. A median of 1 dose of tocilizumab (range, 1-4 doses) was administered. No adverse reactions related to tocilizumab were reported [see Clinical Studies (14.10)].

6.10 Clinical Trials Experience in COVID-19 Patients Treated with Intravenous Tocilizumab (tocilizumab-IV)

The safety of tocilizumab in hospitalized COVID-19 patients was evaluated in a pooled safety population that includes patients enrolled in EMPACTA, COVACTA, AND REMDACTA. The analysis of adverse reactions included a total of 974 patients exposed to tocilizumab. Patients received a single, 60-minute infusion of intravenous tocilizumab 8 mg/kg (maximum dose of 800 mg). If clinical signs or symptoms worsened or did not improve, one additional dose of tocilizumab 8 mg/kg could be administered between 8- 24 hours after the initial dose.

Adverse reactions summarized in Table 3 occurred in at least 3% of tocilizumab-treated patients and more commonly than in patients on placebo in the pooled safety population.

Table 3 Adverse Reactions^1 Identified From the Pooled COVID-19 Safety Population
Adverse Reaction | Tocilizumab 8 mg per kg N = 974 (%) | Placebo N = 483 (%)
Hepatic Transaminases increased | 10% | 8%
Constipation | 9% | 8%
Urinary tract infection | 5% | 4%
Hypertension | 4% | 1%
Hypokalaemia | 4% | 3%
Anxiety | 4% | 2%
Diarrhea | 4% | 2%
Insomnia | 4% | 3%
Nausea | 3% | 2%
^1Patients are counted once for each category regardless of the number of reactions

In the pooled safety population, the rates of infection/serious infection events were 30%/19% in patients receiving tocilizumab versus 32%/23% receiving placebo.

Laboratory Abnormalities

In the pooled safety population of EMPACTA, COVACTA, and REMDACTA, neutrophil counts <1000 cells/mcl occurred in 3.4% of patients who received tocilizumab and 0.5% of patients who received placebo. Platelet counts <50,000 cells/mcl occurred in 3.2% of patients who received tocilizumab and 1.5% of patients who received placebo. ALT or AST at or above 5x ULN occurred in 11.7% of patients who received tocilizumab and 9.9% of patients who received placebo.

6.11 Postmarketing Experience

The following adverse reactions have been identified during post-approval use of tocilizumab products. Because these reactions are reported voluntarily from a population of uncertain size, it is not always possible to reliably estimate their frequency or establish a causal relationship to drug exposure.

- Hypersensitivity Reactions: Fatal anaphylaxis, Stevens-Johnson Syndrome, Drug Reaction with Eosinophilia and Systemic Symptoms (DRESS) [see Warnings and Precautions (5.6)]
- Pancreatitis
- Drug-induced liver injury, Hepatitis, Hepatic failure, Jaundice [see Warnings and Precautions (5.3)]

7 DRUG INTERACTIONS

7.1 Concomitant Drugs for Treatment of Adult Indications

In RA patients, population pharmacokinetic analyses did not detect any effect of methotrexate (MTX), non-steroidal anti-inflammatory drugs or corticosteroids on tocilizumab clearance. Concomitant administration of a single intravenous dose of 10 mg/kg tocilizumab with 10-25 mg MTX once weekly had no clinically significant effect on MTX exposure. Tocilizumab products have not been studied in combination with biological DMARDs such as TNF antagonists [see Dosage and Administration (2.2)].

In GCA patients, no effect of concomitant corticosteroid on tocilizumab exposure was observed.

7.2 Interactions with CYP450 Substrates

Cytochrome P450s in the liver are down-regulated by infection and inflammation stimuli including cytokines such as IL-6. Inhibition of IL-6 signaling in RA patients treated with tocilizumab products may restore CYP450 activities to higher levels than those in the absence of tocilizumab products leading to increased metabolism of drugs that are CYP450 substrates. In vitro studies showed that tocilizumab has the potential to affect expression of multiple CYP enzymes including CYP1A2, CYP2B6, CYP2C9, CYP2C19, CYP2D6 and CYP3A4. Its effect on CYP2C8 or transporters is unknown. In vivo studies with omeprazole, metabolized by CYP2C19 and CYP3A4, and simvastatin, metabolized by CYP3A4, showed up to a 28% and 57% decrease in exposure one week following a single dose of tocilizumab, respectively. The effect of tocilizumab products on CYP enzymes may be clinically relevant for CYP450 substrates with narrow therapeutic index, where the dose is individually adjusted.

Upon initiation or discontinuation of TYENNE, in patients being treated with these types of medicinal products, perform therapeutic monitoring of effect (e.g., warfarin) or drug concentration (e.g., cyclosporine or theophylline) and the individual dose of the medicinal product adjusted as needed. Exercise caution when coadministering TYENNE with CYP3A4 substrate drugs where decrease in effectiveness is undesirable, e.g., oral contraceptives, lovastatin, atorvastatin, etc. The effect of tocilizumab products on CYP450 enzyme activity may persist for several weeks after stopping therapy [see Clinical Pharmacology (12.3)].

7.3 Live Vaccines

Avoid use of live vaccines concurrently with TYENNE [see Warnings and Precautions (5.9)].

8 USE IN SPECIFIC POPULATIONS

8.1 Pregnancy

Risk Summary

The available data with tocilizumab products from a pregnancy exposure registry, retrospective cohort study, pharmacovigilance, and published literature are insufficient to draw conclusions about a drug-associated risk of major birth defects, miscarriage, or other adverse maternal or fetal outcomes. These studies had methodological limitations, including small sample size of tocilizumab exposed groups, missing exposure and outcomes information, and lack of adjustment for cofounders. Monoclonal antibodies, such as tocilizumab products, are actively transported across the placenta during the third trimester of pregnancy and may affect immune response in the in utero exposed infant [see Clinical Considerations]. In animal reproduction studies, intravenous administration of tocilizumab to Cynomolgus monkeys during organogenesis caused abortion/embryo-fetal death at doses 1.25 times and higher than the maximum recommended human dose by the intravenous route of 8 mg per kg every 2 to 4 weeks. The literature in animals suggests that inhibition of IL-6 signaling may interfere with cervical ripening and dilatation and myometrial contractile activity leading to potential delays of parturition [see Data]. Based on the animal data, there may be a potential risk to the fetus.

The estimated background risk of major birth defects and miscarriage for the indicated population is unknown. All pregnancies have a background risk of birth defect, loss or other adverse outcomes. In the U.S. general population, the estimated background risk of major birth defects and miscarriage in clinically recognized pregnancies is 2 to 4% and 15 to 20%, respectively.

Clinical Considerations

Fetal/Neonatal adverse reactions

Monoclonal antibodies are increasingly transported across the placenta as pregnancy progresses, with the largest amount transferred during the third trimester. Risks and benefits should be considered prior to administering live or live-attenuated vaccines to infants exposed to TYENNE in utero [see Warnings and Precautions 5.9)].

Disease-associated Maternal Risk

Published data suggest that the risk of adverse pregnancy outcomes in women with rheumatoid arthritis is associated with increased disease activity. Adverse pregnancy outcomes include preterm delivery (before 37 weeks of gestation), low birth weight (less than 2500 g) infants, and small for gestational age at birth.

Data

Animal Data

An embryo-fetal developmental toxicity study was performed in which pregnant Cynomolgus monkeys were treated intravenously with tocilizumab at daily doses of 2, 10, or 50 mg/ kg during organogenesis from gestation day (GD) 20-50. Although there was no evidence for a teratogenic/dysmorphogenic effect at any dose, tocilizumab produced an increase in the incidence of abortion/embryo-fetal death at doses 1.25 times and higher the MRHD by the intravenous route at maternal intravenous doses of 10 and 50 mg/ kg. Testing of a murine analogue of tocilizumab in mice did not yield any evidence of harm to offspring during the pre- and postnatal development phase when dosed at 50 mg/kg intravenously with treatment every three days from implantation (GD 6) until post-partum day 21 (weaning). There was no evidence for any functional impairment of the development and behavior, learning ability, immune competence and fertility of the offspring.

Parturition is associated with significant increases of IL-6 in the cervix and myometrium. The literature suggests that inhibition of IL-6 signaling may interfere with cervical ripening and dilatation and myometrial contractile activity leading to potential delays of parturition. For mice deficient in IL-6 (ll6-/- null mice), parturition was delayed relative to wild-type (ll6+/+) mice.

Administration of recombinant IL-6 to ll6-/- null mice restored the normal timing of delivery.

8.2 Lactation

Risk Summary

No information is available on the presence of tocilizumab products in human milk, the effects of the drug on the breastfed infant, or the effects of the drug on milk production. Maternal immunoglobulin G (IgG) is present in human milk. If tocilizumab products are transferred into human milk, the effects of local exposure in the gastrointestinal tract and potential limited systemic exposure in the infant to tocilizumab products are unknown.

The lack of clinical data during lactation precludes clear determination of the risk of tocilizumab products to an infant during lactation; therefore the developmental and health benefits of breastfeeding should be considered along with the mother's clinical need for TYENNE and the potential adverse effects on the breastfed child from TYENNE or from the underlying maternal condition.

8.4 Pediatric Use

TYENNE by intravenous use is indicated for the treatment of pediatric patients with:

- Active systemic juvenile idiopathic arthritis in patients 2 years of age and older
- Active polyarticular juvenile idiopathic arthritis in patients 2 years of age and older
- Severe or life-threatening CAR T cell-induced cytokine release syndrome (CRS) in patients 2 years of age and older.

TYENNE by subcutaneous use is indicated for the treatment of pediatric patients with:

- Active polyarticular juvenile idiopathic arthritis in patients 2 years of age and older
- Active systemic juvenile idiopathic arthritis in patients 2 years of age and older

The safety and effectiveness of TYENNE in pediatric patients with conditions other than PJIA, SJIA or CRS have not been established. The safety and effectiveness in pediatric patients below the age of 2 have not been established in PJIA, SJIA or CRS.

Systemic Juvenile Idiopathic Arthritis – Intravenous Use

A multicenter, open-label, single arm study to evaluate the PK, safety and exploratory PD and efficacy of tocilizumab over 12-weeks in SJIA patients (N=11) under 2 years of age was conducted. Patients received intravenous tocilizumab 12 mg/kg every two weeks. Concurrent use of stable background treatment with corticosteroids, MTX, and/or non-steroidal anti-inflammatory drugs was permitted.

Patients who completed the 12-week period could continue to the optional extension period (a total of 52-weeks or until the age of 2 years, whichever was longer).

The primary PK endpoints (Cmax, Ctrough and AUC2weeks) of tocilizumab at steady-state in this study were within the ranges of these parameters observed in patients with SJIA aged 2 to 17 years.

The safety and immunogenicity of tocilizumab for patien ts with SJIA under 2 years of age was assessed descriptively. SAEs, AEs leading to discontinuation, and infectious AEs were reported by 27.3%, 36.4%, and 81.8% of patients. Six patients (54.5%) experienced hypersensitivity reactions, defined as all adverse events occurring during or within 24 hours after an infusion considered related to tocilizumab. Three of these patients experienced serious hypersensitivity reactions and were withdrawn from the study. Three patients with hypersensitivity reactions (two with serious hypersensitivity reactions) developed treatment induced anti- tocilizumab antibodies after the event. There were no cases of MAS based on the protocol-specified criteria, but 2 cases of suspected MAS based on Ravelli criteria [Ravelli A, Minoia F, Davì S on behalf of the Paediatric Rheumatology International Trials Organisation, the Childhood Arthritis and Rheumatology Research Alliance, the Pediatric Rheumatology Collaborative Study Group, and the Histiocyte Society, et al. 2016 Classification Criteria for Macrophage Activation Syndrome Complicating Systemic Juvenile Idiopathic Arthritis. Annals of the Rheumatic Diseases 2016;75:481-489.] .

Cytokine Release Syndrome – Intravenous Use
In the retrospective analysis of pooled outcome data for patients treated with tocilizumab for CAR T cell-induced CRS, 25 patients were children (2 years up to 12 years of age), and 17 patients were adolescents (12 years up to 18 years of age). There were no differences between the pediatric patients and the adults for safety or efficacy.

8.5 Geriatric Use

Of the 2644 patients who received tocilizumab in Studies I to V [see Clinical Studies (14)], a total of 435 rheumatoid arthritis patients were 65 years of age and older, including 50 patients 75 years and older. Of the 1069 patients who received tocilizumab-SC in studies SC-I and SC-II there were 295 patients 65 years of age and older, including 41 patients 75 years and older. The frequency of serious infection among tocilizumab treated subjects 65 years of age and older was higher than those under the age of 65. As there is a higher incidence of infections in the elderly population in general, caution should be used when treating the elderly.

Clinical studies that included tocilizumab for CRS did not include sufficient numbers of patients aged 65 and over to determine whether they respond differently from younger patients.
In the EMPACTA, COVACTA, and REMDACTA studies, of the 974 COVID-19 patients in the tocilizumab arm, 375 (39%) were 65 years of age or older. No overall differences in safety or effectiveness of tocilizumab were observed between patients 65 years of age and older and those under the age of 65 years of age in these studies [see Adverse Reactions (6.1) and Clinical Studies (14.10)].

In the RECOVERY study, of the 2022 COVID-19 patients in the tocilizumab arm, 930 (46%) were 65 years of age or older. No overall differences in effectiveness of tocilizumab were observed between patients 65 years of age and older and those under the age 65 years of age in this study [see Clinical Studies (14.10)].

8.6 Hepatic Impairment

The safety and efficacy of tocilizumab products have not been studied in patients with hepatic impairment, including patients with positive HBV and HCV serology [see Warnings and Precautions (5.8)].

8.7 Renal Impairment

No dose adjustment is required in patients with mild or moderate renal impairment. Tocilizumab products have not been studied in patients with severe renal impairment [see Clinical Pharmacology (12.3)].

9 DRUG ABUSE AND DEPENDENCE

No studies on the potential for tocilizumab products to cause dependence have been performed. However, there is no evidence from the available data that tocilizumab products treatment results in dependence.

10 OVERDOSAGE

There are limited data available on overdoses with tocilizumab products. One case of accidental overdose was reported with intravenous tocilizumab in which a patient with multiple myeloma received a dose of 40 mg per kg. No adverse drug reactions were observed. No serious adverse drug reactions were observed in healthy volunteers who received single doses of up to 28 mg per kg, although all 5 patients at the highest dose of 28 mg per kg developed dose-limiting neutropenia.

In case of an overdose, it is recommended that the patient be monitored for signs and symptoms of adverse reactions. Patients who develop adverse reactions should receive appropriate symptomatic treatment.

11 DESCRIPTION

Tocilizumab-aazg is a recombinant humanized anti-human interleukin 6 (IL-6) receptor monoclonal antibody of the immunoglobulin IgG1κ (gamma 1, kappa) subclass with a typical H2L2 polypeptide structure. Each light chain and heavy chain consists of 214 and 448 amino acids (excluding the C-terminal lysine), respectively.

The four polypeptide chains are linked intra- and inter-molecularly by disulfide bonds. Tocilizumab-aazg has a molecular weight of approximately 148 kDa. The antibody is produced in mammalian (Chinese hamster ovary) cells.

Intravenous Infusion

TYENNE (tocilizumab-aazg) injection is a sterile, clear and colorless to pale yellow, histidine buffered preservative-free solution with a pH of approximately 6 for further dilution prior to intravenous infusion. Each single-dose vial is available at a concentration of 20 mg/mL containing 80 mg/4 mL, 200 mg/10 mL, or 400 mg/20 mL of TYENNE. Each mL of solution contains arginine (17.4 mg), histidine (3.1 mg), lactic acid (0.9 mg), polysorbate 80 (0.2 mg), sodium chloride (0.6 mg), and Water for Injection, USP. Hydrochloric acid and sodium hydroxide are added to adjust the pH.

Subcutaneous Injection

TYENNE (tocilizumab-aazg) injection is a sterile, clear, colorless to pale yellow, preservative-free, histidine buffered solution with a pH of approximately 6 for subcutaneous use. It is supplied in a ready-to-use, single-dose 0.9 mL prefilled syringe (PFS) with a needle safety device or in a ready-to-use, single-dose 0.9 mL autoinjector that delivers 162 mg tocilizumab-aazg, arginine (16.7 mg), histidine (2.0 mg), lactic acid (0.9 mg), polysorbate 80 (0.2 mg), sodium chloride (0.6 mg), and Water for Injection, USP. Hydrochloric acid and sodium hydroxide are added to adjust the pH.

12 CLINICAL PHARMACOLOGY

12.1 Mechanism of Action

Tocilizumab products bind to both soluble and membrane-bound IL-6 receptors (sIL-6R and mIL-6R), and have been shown to inhibit IL-6-mediated signaling through these receptors. IL-6 is a pleiotropic pro-inflammatory cytokine produced by a variety of cell types including T- and B-cells, lymphocytes, monocytes and fibroblasts. IL-6 has been shown to be involved in diverse physiological processes such as T-cell activation, induction of immunoglobulin secretion, initiation of hepatic acute phase protein synthesis, and stimulation of hematopoietic precursor cell proliferation and differentiation. IL-6 is also produced by synovial and endothelial cells leading to local production of IL-6 in joints affected by inflammatory processes such as rheumatoid arthritis.

12.2 Pharmacodynamics

In clinical studies in RA patients with the 4 mg per kg and 8 mg per kg intravenous doses or the 162 mg weekly and every other weekly subcutaneous doses of tocilizumab, decreases in levels of C-reactive protein (CRP) to within normal ranges were seen as early as week 2. Changes in pharmacodynamic parameters were observed (i.e., decreases in rheumatoid factor, erythrocyte sedimentation rate (ESR), serum amyloid A, fibrinogen and increases in hemoglobin) with doses, however the greatest improvements were observed with 8 mg per kg tocilizumab. Pharmacodynamic changes were also observed to occur after tocilizumab administration in GCA, PJIA, and SJIA patients (decreases in CRP, ESR, and increases in hemoglobin). The relationship between these pharmacodynamic findings and clinical efficacy is not known.

In healthy subjects administered tocilizumab in doses from 2 to 28 mg per kg intravenously and 81 to 162 mg subcutaneously, absolute neutrophil counts decreased to the nadir 3 to 5 days following tocilizumab administration. Thereafter, neutrophils recovered towards baseline in a dose dependent manner. Rheumatoid arthritis and GCA patients demonstrated a similar pattern of absolute neutrophil counts following tocilizumab administration [see Warnings and Precautions (5.4)].

12.3 Pharmacokinetics

PK of tocilizumab is characterized by nonlinear elimination which is a combination of linear clearance and Michaelis-Menten elimination. The nonlinear part of tocilizumab elimination leads to an increase in exposure that is more than dose-proportional. The pharmacokinetic parameters of tocilizumab do not change with time. Due to the dependence of total clearance on tocilizumab serum concentrations, the half-life of tocilizumab is also concentration-dependent and varies depending on the serum concentration level. Population pharmacokinetic analyses in any patient population tested so far indicate no relationship between apparent clearance and the presence of anti-drug antibodies.

Rheumatoid Arthritis – Intravenous and Subcutaneous Administration

The pharmacokinetics in healthy subjects and RA patients suggest that PK is similar between the two populations.

The population PK model was developed from an analysis dataset composed of an IV dataset of 1793 patients from Study I, Study III, Study IV, and Study V, and from an IV and SC dataset of 1759 patients from Studies SC-I and SC-II. Cmean is included in place of AUCtau, since for dosing regimens with different inter-dose intervals, the mean concentration over the dosing period characterizes the comparative exposure better than AUCtau.

At high serum concentrations, when total clearance of tocilizumab is dominated by linear clearance, a terminal half-life of approximately 21.5 days was derived from the population parameter estimates.

For doses of 4 mg/kg tocilizumab given every 4 weeks intravenously, the estimated median (range) Cmax, Ctrough, and Cmean of tocilizumab at steady state were 86.1 (44.8–202) mcg/mL, 0.1 (0.0–14.6) mcg/mL, and 18.0 (8.9– 50.7) mcg/mL, respectively. For doses of 8 mg/kg tocilizumab given every 4 weeks intravenously, the estimated median (range) Cmax, Ctrough, and Cmean of tocilizumab were 176 (75.4–557) mcg/mL, 13.4 (0.1–154) mcg/mL, and 54.0 (17–260) mcg/mL, respectively. Cmax increased dose-proportionally between doses of 4 and 8 mg/kg IV every 4 weeks, while a greater than dose-proportional increase was observed in Cmean and Ctrough. At steady-state, Cmean and Ctrough were 3.0 and 134 fold higher at 8 mg/kg as compared to 4 mg/kg, respectively.

The accumulation ratios for AUC and Cmax after multiple doses of 4 and 8 mg/kg IV Q4W are low, while the accumulation ratios for Ctrough are higher (2.62 and 2.47, respectively). For Cmax, greater than 90% of the steady-state value was reached after the 1st IV infusion. For AUCtau and Cmean, 90% of the steady-state value was reached after the 1st and 3rd infusion for 4 mg/kg and 8 mg/kg IV, while for Ctrough, approximately 90% of the steady-state value was reached after the 4th IV infusion after both doses.

For doses of 162 mg given every other week subcutaneously, the estimated median (range) steady-state Cmax, Ctrough, and Cmean of tocilizumab were 12.1 (0.4–49.3) mcg/mL, 4.1 (0.0–34.2) mcg/mL, and 9.2 (0.2– 43.6) mcg/mL, respectively.

For doses of 162 mg given every week subcutaneously, the estimated median (range) steady-state Cmax, Ctrough, and Cmean of tocilizumab were 49.8 (3–150) mcg/mL, 42.9 (1.3–144) mcg/mL, and 47.3 (2.4–147) mcg/mL, respectively. Exposures after the 162 mg SC QW regimen were greater by 5.1 (Cmean) to 10.5 fold (Ctrough) compared to the 162 mg SC Q2W regimen.

Accumulation ratios after multiple doses of either SC regimen were higher than after IV regimen with the highest ratios for Ctrough (6.02 and 6.30, for 162 mg SC Q2W and 162 mg SC QW, respectively). The higher accumulation for Ctrough was expected based on the nonlinear clearance contribution at lower concentrations. For Cmax, greater than 90% of the steady-state value was reached after the 5th SC and the 12th SC injection with the Q2W and QW regimens, respectively. For AUCtau and Cmean, 90% of the steady-state value was reached after the 6th and 12th injections for the 162 mg SC Q2W and QW regimens, respectively. For Ctrough, approximately 90% of the steady-state value was reached after the 6th and 12th injections for the 162 mg SC Q2W and QW regimens, respectively.

Population PK analysis identified body weight as a significant covariate impacting the pharmacokinetics of tocilizumab. When given IV on a mg/kg basis, individuals with body weight ≥ 100 kg are predicted to have mean steady-state exposures higher than mean values for the patient population. Therefore, tocilizumab doses exceeding 800 mg per infusion are not recommended in patients with RA [see Dosage and Administration (2.2)]. Due to the flat dosing employed for SC administration of tocilizumab, no modifications are necessary by this dosing route.

Giant Cell Arteritis – Subcutaneous and Intravenous Administration

The pharmacokinetics of tocilizumab S C in GCA patients was determined using a population pharmacokinetic analysis on a dataset composed of 149 GCA patients treated with 162 mg subcutaneously every week or with 162 mg subcutaneously every other week.

For the 162 mg every week dose, the estimated median (range) steady-state Cmax, Ctrough and Cmean of tocilizumab SC were 72.1 (12.2–151) mcg/mL, 67.2 (10.7–145) mcg/mL, and 70.6 (11.7–149) mcg/mL, respectively. The accumulation ratios for Cmean or AUCtau, Ctrough, and Cmax were 10.9, 9.6, and 8.9, respectively. Steady state was reached after 17 weeks. For the 162 mg every other week dose, the estimated median (range) steady-state Cmax, Ctrough, and Cmean of tocilizumab were 17.2 (1.1–56.2) mcg/mL, 7.7 (0.1–37.3) mcg/mL, and 13.7 (0.5– 49) mcg/mL, respectively. The accumulation ratios for Cmean or AUCtau, Ctrough, and Cmax were 2.8, 5.6, and 2.3 respectively. Steady-state was reached after 14 weeks.

The pharmacokinetics of tocilizumab IV in GCA patients was characterized by a non-compartmental pharmacokinetic analysis which included 22 patients treated with 6 mg/kg intravenously every 4 weeks for 20 weeks. The median (range) Cmax, Ctrough and Cmean of tocilizumab at steady state were 178 (115-320) mcg/mL, 22.7 (3.38-54.5) mcg/mL and 57.5 (32.9-110) mcg/mL, respectively. Steady state trough concentrations were within the range observed in GCA patients treated with 162 mg TCZ SC administered every week or every other week. Based on pharmacokinetic exposure and extrapolation between RA and GCA patients, when given IV on a mg/kg basis, tocilizumab doses exceeding 600 mg per infusion are not recommended in patients with GCA [see Dosage and Administration (2.3)].

Polyarticular Juvenile Idiopathic Arthritis – Intravenous and Subcutaneous Administration

The pharmacokinetics of tocilizumab (TCZ) in PJIA patients was characterized by a population pharmacokinetic analysis which included 188 patients who were treated with TCZ IV or 52 patients treated with TCZ SC.

For doses of 8 mg/kg tocilizumab (patients with a body weight at or above 30 kg) given every 4 weeks intravenously, the estimated median (range) Cmax, Ctrough, and Cmean of tocilizumab at steady state were 181 (114–331) mcg/mL, 3.28 (0.02–35.4) mcg/mL, and 38.6 (22.2–83.8) mcg/mL, respectively. For doses of 10 mg/kg tocilizumab (patients with a body weight less than 30 kg) given every 4 weeks intravenously, the estimated median (range) Cmax, Ctrough, and Cmean of tocilizumab were 167 (125–220) mcg/mL, 0.35 (0– 11.8) mcg/mL, and 30.8 (16.0–48.0) mcg/mL, respectively.

The accumulation ratios were 1.05 and 1.16 for AUC4weeks, and 1.43 and 2.22 for Ctrough for 10 mg/kg (BW less than 30 kg) and 8 mg/kg (BW at or above 30 kg) intravenous doses, respectively. No accumulation for Cmax was observed. Following 10 mg/kg and 8 mg/kg TCZ IV every 4 weeks doses in PJIA patients (aged 2 to 17 years), steady state concentrations (trough and average) were within the range of exposures in adult RA patients following 4 mg/kg and 8 mg/kg every 4 weeks, and steady state peak concentrations in PJIA patients were comparable to those following 8 mg/kg every 4 weeks in adult RA patients.

For doses of 162 mg tocilizumab (patients with a body weight at or above 30 kg) given every 2 weeks subcutaneously, the estimated median (range) Cmax, Ctrough, and Cmean of tocilizumab were 29.7 (7.56–50.3) mcg/mL, 12.7 (0.19–23.8) mcg/mL, and 23.0 (3.86–36.9) mcg/mL, respectively. For doses of 162 mg tocilizumab (patients with a body weight less than 30 kg) given every 3 weeks subcutaneously, the estimated median (range) Cmax, Ctrough, and Cmean of tocilizumab were 62.4 (39.4–121) mcg/mL, 13.4 (0.21–52.3) mcg/mL, and 35.7 (17.4–91.8) mcg/mL, respectively.

The accumulation ratios were 1.46 and 2.04 for AUC4weeks, 2.08 and 3.58 for Ctrough, and 1.32 and 1.72 for Cmax, for 162 mg given every 3 weeks (BW less than 30 kg) and 162 mg given every 2 weeks (BW at or above 30 kg) subcutaneous doses, respectively. Following subcutaneous dosing, steady state Ctrough was comparable for patients in the two body weight groups, while steady-state Cmax and Cmean were higher for patients in the less than 30 kg group compared to the group at or above 30 kg. All patients treated with TCZ SC had steady-state Ctrough at or higher than that achieved with TCZ IV across the spectrum of body weights. The average and trough concentrations in patients after subcutaneous dosing were within the range of those achieved in adult patients with RA following the subcutaneous administration of the recommended regimens.

Systemic Juvenile Idiopathic Arthritis – Intravenous and Subcutaneous Administration

The pharmacokinetics of tocilizumab (TCZ) in SJIA patients was characterized by a population pharmacokinetic analysis which included 89 patients who were treated with TCZ IV or 51 patients treated with TCZ SC.

For doses of 8 mg/kg tocilizumab (patients with a body weight at or above 30 kg) given every 2 weeks intravenously, the estimated median (range) Cmax, Ctrough, and Cmean of tocilizumab were 253 (120–404) mcg/mL, 70.7 (5.26–127) mcg/mL, and 117 (37.6–199) mcg/mL, respectively. For doses of 12 mg/kg tocilizumab (patients with a body weight less than 30 kg) given every 2 weeks intravenously, the estimated median (range) Cmax, Ctrough, and Cmean of tocilizumab were 274 (149–444) mcg/mL, 65.9 (19.0–135) mcg/mL, and 124 (60–194) mcg/mL, respectively.

The accumulation ratios were 1.95 and 2.01 for AUC4weeks, and 3.41 and 3.20 for Ctrough for 12 mg/kg (BW less than 30 kg) and 8 mg/kg (BW at or above 30 kg) intravenous doses, respectively. Accumulation data for Cmax were 1.37 and 1.42 for 12 mg/kg (BW less than 30 kg) and 8 mg/kg (BW at or above 30 kg) intravenous doses, respectively. Following every other week dosing with tocilizumab IV, steady state was reached by 8 weeks for both body weight groups. Mean estimated tocilizumab exposure parameters were similar between the two dose groups defined by body weight.

For doses of 162 mg tocilizumab (patients with a body weight at or above 30 kg) given every week subcutaneously, the estimated median (range) Cmax, Ctrough, and Cmean of tocilizumab were 89.8 (26.4–190) mcg/mL, 72.4 (19.5–158) mcg/mL, and 82.4 (23.9–169) mcg/mL, respectively. For doses of 162 mg tocilizumab (patients with a body weight less than 30 kg) given every 2 weeks subcutaneously, the estimated median (range) Cmax, Ctrough, and Cmean of tocilizumab were 127 (51.7–266) mcg/mL, 64.2 (16.6–136) mcg/mL, and 92.7 (38.5–199) mcg/mL, respectively.

The accumulation ratios were 2.27 and 4.28 for AUC4weeks, 3.21 and 4.39 for Ctrough, and 1.88 and 3.66 for Cmax, for 162 mg given every 2 weeks (BW less than 30 kg) and 162 mg given every week (BW at or above 30 kg) subcutaneous doses, respectively. Following subcutaneous dosing, steady state was reached by 12 weeks for both body weight groups. All patients treated with tocilizumab SC had steady-state Cmax lower than that achieved with tocilizumab IV across the spectrum of body weights. Trough and mean concentrations in patients after SC dosing were similar to those achieved with tocilizumab IV across body weights.

COVID-19 -Intravenous Administration

The pharmacokinetics of tocilizumab in COVID-19 patients was characterized by a population pharmacokinetic analysis of a dataset composed of 380 adult patients treated with tocilizumab 8 mg/kg intravenously (IV) in the COVACTA study [see Clinical Studies (14.10)] and another clinical study.

For one dose of 8 mg/kg tocilizumab IV, the estimated median (range) Cmax and Cday28 of tocilizumab were 151 (77.5-319) mcg/mL and 0.229 (0.00119-19.4) mcg/mL, respectively. For two doses of 8 mg/kg tocilizumab IV separated by at least 8 hours, the estimated median (range) Cmax and Cday28 of tocilizumab was 290 (152-604) mcg/mL and 7.04 (0.00474-54.8) mcg/mL, respectively. The weight-tiered dosing used in RECOVERY study, 800 mg for patients >90 kg, 600 mg for patients >65 and ≤90 kg, 400 mg for patients >40 and ≤65 kg, and 8mg/kg for patients ≤40 kg, is comparable to 8 mg/kg dosing and is expected to have similar exposure.

Absorption

Following subcutaneous dosing, the absorption half-life was around 4 days in RA and GCA patients. The bioavailability for the subcutaneous formulation was 80%.

Following subcutaneous dosing in PJIA patients, the absorption half-life was around 2 days, and the bioavailability for the subcutaneous formulation in PJIA patients was 96%.

Following subcutaneous dosing in SJIA patients, the absorption half-life was around 2 days, and the bioavailability for the SC formulation in SJIA patients was 95%.

In RA patients the median values of Tmax were 2.8 days after the tocilizumab every week dose and 4.7 days after the tocilizumab every other week dose.

In GCA patients, the median values of Tmax were 3 days after the tocilizumab every week dose and 4.5 days after the tocilizumab every other week dose.

Distribution

Following intravenous dosing, tocilizumab undergoes biphasic elimination from the circulation. In rheumatoid arthritis patients the central volume of distribution was 3.5 L and the peripheral volume of distribution was 2.9 L, resulting in a volume of distribution at steady state of 6.4 L.

In GCA patients, the central volume of distribution was 4.09 L, the peripheral volume of distribution was 3.37 L resulting in a volume of distribution at steady state of 7.46 L.

In pediatric patients with PJIA, the central volume of distribution was 1.98 L, the peripheral volume of distribution was 2.1 L, resulting in a volume of distribution at steady state of 4.08 L.

In pediatric patients with SJIA, the central volume of distribution was 1.87 L, the peripheral volume of distribution was 2.14 L resulting in a volume of distribution at steady state of 4.01 L.

In COVID-19 patients treated with one or two infusions of tocilizumab 8 mg/kg intravenously separated by 8 hours, the estimated central volume of distribution was 4.52 L, and the estimated peripheral volume of distribution was 4.23 L, resulting in a volume of distribution of 8.75 L.

Elimination

Tocilizumab is eliminated by a combination of linear clearance and nonlinear elimination. The concentration-dependent nonlinear elimination plays a major role at low tocilizumab concentrations. Once the nonlinear pathway is saturated, at higher tocilizumab concentrations, clearance is mainly determined by the linear clearance. The saturation of the nonlinear elimination leads to an increase in exposure that is more than dose-proportional. The pharmacokinetic parameters of tocilizumab do not change with time.

Population pharmacokinetic analyses in any patient population tested so far indicate no relationship between apparent clearance and the presence of anti-drug antibodies.

The linear clearance in the population pharmacokinetic analysis was estimated to be 12.5 mL per h in RA patients, 6.7 mL per h in GCA patients, 5.8 mL per h in pediatric patients with PJIA, and 5.7 mL per h in pediatric patients with SJIA. In COVID-19 patients, serum concentrations were below the limit of quantification after 35 days on average following one infusion of tocilizumab 8 mg/kg intravenously. The average linear clearance in the population pharmacokinetic analysis was estimated to be 17.6 mL per hour in patients with baseline ordinal scale category 3 (OS 3, patients requiring supplemental oxygen), 22.5 mL per hour in patients with baseline OS 4 (patients requiring high-flow oxygen or non-invasive ventilation), 29 mL per hour in patients with baseline OS 5 (patients requiring mechanical ventilation), and 35.4 mL per hour in patients with baseline OS 6 (patients requiring extracorporeal membrane oxygenation (ECMO) or mechanical ventilation and additional organ support).

Due to the dependence of total clearance on tocilizumab serum concentrations, the half-life of tocilizumab is also concentration-dependent and varies depending on the serum concentration level.

For intravenous administration in RA patients, the concentration-dependent apparent t1/2 is up to 11 days for 4 mg per kg and up to 13 days for 8 mg per kg every 4 weeks in patients with RA at steady-state. For subcutaneous administration in RA patients, the concentration-dependent apparent t1/2 is up to 13 days for 162 mg every week and 5 days for 162 mg every other week in patients with RA at steady-state.

In GCA patients at steady state, the effective t1/2 of tocilizumab varied between 18.3 and 18.9 days for 162 mg subcutaneously every week dosing regimen and between 4.2 and 7.9 days for 162 mg subcutaneously every other week dosing regimen. For intravenous administration in GCA patients, the TCZ concentration-dependent apparent t1/2 was 13.2 days following 6 mg/kg every 4 weeks.

The t1/2 of tocilizumab in children with PJIA is up to 17 days for the two body weight categories (8 mg/kg for body weight at or above 30 kg or 10 mg/kg for body weight below 30 kg) during a dosing interval at steady state. For subcutaneous administration, the t1/2 of tocilizumab in PJIA patients is up to 10 days for the two body weight categories (every other week regimen for body weight at or above 30 kg or every 3 week regimen for body weight less than 30 kg) during a dosing interval at steady state.

The t1/2 of tocilizumab intravenous in pediatric patients with SJIA is up to 16 days for the two body weight categories (8 mg/kg for body weight at or above 30 kg and 12 mg/kg for body weight below 30 kg every other week) during a dosing interval at steady-state. Following subcutaneous administration, the effective t1/2 of tocilizumab subcutaneous in SJIA patients is up to 14 days for both the body weight categories (162 mg every week for body weight at or above 30 kg and 162 mg every two weeks for body weight below 30 kg) during a dosing interval at steady state.

Specific Populations

Population pharmacokinetic analyses in adult rheumatoid arthritis patients and GCA patients showed that age, gender and race did not affect the pharmacokinetics of tocilizumab. Linear clearance was found to increase with body size. In RA patients, the body weight-based dose (8 mg per kg) resulted in approximately 86% higher exposure in patients who are greater than 100 kg in comparison to patients who are less than 60 kg. There was an inverse relationship between tocilizumab exposure and body weight for flat dose subcutaneous regimens.

In GCA patients treated with tocilizumab-SC, higher exposure was observed in patients with lower body weight. For the 162 mg every week subcutaneous dosing regimen, the steady-state Cmean was 51% higher in patients with body weight less than 60 kg compared to patients weighing between 60 to 100 kg. For the 162 mg every other week subcutaneous regimen, the steady-state Cmean was 129% higher in patients with body weight less than 60 kg compared to patients weighing between 60 to 100 kg. There is limited data for patients above 100 kg (n=7).

In COVID-19 patients, exposure following body-weight-based intravenous dosing (8 mg per kg tocilizumab up to 100 kg body weight with a maximum dose of 800 mg) was dependent on body weight and disease severity assessed by an ordinal scale (OS). Within an OS category, compared to patients with a mean body weight of 80 kg, exposure was 20% lower in patients weighing less than 60 kg. Exposure in patients weighing more than 100 kg was in the same range as exposure in patients with a mean body weight of 80 kg. For an 80 kg patient, exposure decreases as OS category increases; for each category increase, exposure decreases by 13%.

Patients with Hepatic Impairment

No formal study of the effect of hepatic impairment on the pharmacokinetics of tocilizumab was conducted.

Patients with Renal Impairment

No formal study of the effect of renal impairment on the pharmacokinetics of tocilizumab was conducted.

Most of the RA and GCA patients in the population pharmacokinetic analysis had normal renal function or mild renal impairment. Mild renal impairment (estimated creatinine clearance less than 80 mL per min and at or above 50 mL per min based on Cockcroft-Gault formula) did not impact the pharmacokinetics of tocilizumab.

Approximately one-third of the patients in the tocilizumab-SC GCA clinical trial had moderate renal impairment at baseline (estimated creatinine clearance of 30-59 mL/min). No impact on tocilizumab exposure was noted in these patients.

No dose adjustment is required in patients with mild or moderate renal impairment.

Drug Interaction Studies

In vitro data suggested that IL-6 reduced mRNA expression for several CYP450 isoenzymes including CYP1A2, CYP2B6, CYP2C9, CYP2C19, CYP2D6 and CYP3A4, and this reduced expression was reversed by co-incubation with tocilizumab at clinically relevant concentrations. Accordingly, inhibition of IL-6 signaling in RA patients treated with tocilizumab may restore CYP450 activities to higher levels than those in the absence of tocilizumab leading to increased metabolism of drugs that are CYP450 substrates. Its effect on CYP2C8 or transporters (e.g., P-gp) is unknown. This is clinically relevant for CYP450 substrates with a narrow therapeutic index, where the dose is individually adjusted. Upon initiation of TYENNE, in patients being treated with these types of medicinal products, therapeutic monitoring of the effect (e.g., warfarin) or drug concentration (e.g., cyclosporine or theophylline) should be performed and the individual dose of the medicinal product adjusted as needed.

Caution should be exercised when TYENNE is coadministered with drugs where decrease in effectiveness is undesirable, e.g., oral contraceptives (CYP3A4 substrates) [see Drug Interactions (7.2)].

Simvastatin

Simvastatin is a CYP3A4 and OATP1B1 substrate. In 12 RA patients not treated with tocilizumab, receiving 40 mg simvastatin, exposures of simvastatin and its metabolite, simvastatin acid, was 4- to 10-fold and 2-fold higher, respectively, than the exposures observed in healthy subjects. One week following administration of a single infusion of tocilizumab (10 mg per kg), exposure of simvastatin and simvastatin acid decreased by 57% and 39%, respectively, to exposures that were similar or slightly higher than those observed in healthy subjects. Exposures of simvastatin and simvastatin acid increased upon withdrawal of tocilizumab in RA patients. Selection of a particular dose of simvastatin in RA patients should take into account the potentially lower exposures that may result after initiation of TYENNE (due to normalization of CYP3A4) or higher exposures after discontinuation of TYENNE.

Omeprazole

Omeprazole is a CYP2C19 and CYP3A4 substrate. In RA patients receiving 10 mg omeprazole, exposure to omeprazole was approximately 2 fold higher than that observed in healthy subjects. In RA patients receiving 10 mg omeprazole, before and one week after tocilizumab infusion (8 mg per kg), the omeprazole AUCinf decreased by 12% for poor (N=5) and intermediate metabolizers (N=5) and by 28% for extensive metabolizers (N=8) and were slightly higher than those observed in healthy subjects.

Dextromethorphan

Dextromethorphan is a CYP2D6 and CYP3A4 substrate. In 13 RA patients receiving 30 mg dextromethorphan, exposure to dextromethorphan was comparable to that in healthy subjects. However, exposure to its metabolite, dextrorphan (a CYP3A4 substrate), was a fraction of that observed in healthy subjects. One week following administration of a single infusion of tocilizumab (8 mg per kg), dextromethorphan exposure was decreased by approximately 5%. However, a larger decrease (29%) in dextrorphan levels was noted after tocilizumab infusion.

13 NONCLINICAL TOXICOLOGY

13.1 Carcinogenesis, Mutagenesis, Impairment of Fertility

No long-term animal studies have been performed to establish the carcinogenicity potential of tocilizumab products. Literature indicates that the IL-6 pathway can mediate anti-tumor responses by promoting increased immune cell surveillance of the tumor microenvironment. However, available published evidence also supports that IL-6 signaling through the IL-6 receptor may be involved in pathways that lead to tumorigenesis. The malignancy risk in humans from an antibody that disrupts signaling through the IL-6 receptor, such as tocilizumab, is presently unknown.

Fertility and reproductive performance were unaffected in male and female mice that received a murine analogue of tocilizumab administered by the intravenous route at a dose of 50 mg/kg every three days.

14 CLINICAL STUDIES

14.1 Rheumatoid Arthritis – Intravenous Administration

The efficacy and safety of intravenously administered tocilizumab was assessed in five randomized, double-blind, multicenter studies in patients greater than 18 years with active rheumatoid arthritis diagnosed according to American College of Rheumatology (ACR) criteria. Patients had at least 8 tender and 6 swollen joints at baseline. Tocilizumab was given intravenously every 4 weeks as monotherapy (Study I), in combination with methotrexate (MTX) (Studies II and III) or other disease-modifying anti-rheumatic drugs (DMARDs) (Study IV) in patients with an inadequate response to those drugs, or in combination with MTX in patients with an inadequate response to TNF antagonists (Study V).

Study I (NCT00109408) evaluated patients with moderate to severe active rheumatoid arthritis who had not been treated with MTX within 24 weeks prior to randomization, or who had not discontinued previous methotrexate treatment as a result of clinically important toxic effects or lack of response. In this study, 67% of patients were MTX-naïve, and over 40% of patients had rheumatoid arthritis less than 2 years. Patients received tocilizumab 8 mg per kg monotherapy or MTX alone (dose titrated over 8 weeks from 7.5 mg to a maximum of 20 mg weekly). The primary endpoint was the proportion of tocilizumab patients who achieved an ACR 20 response at Week 24.

Study II (NCT00106535) was a 104-week study with an optional 156-week extension phase that evaluated patients with moderate to severe active rheumatoid arthritis who had an inadequate clinical response to MTX. Patients received tocilizumab 8 mg per kg, tocilizumab 4 mg per kg, or placebo every four weeks, in combination with MTX (10 to 25 mg weekly). Upon completion of 52-weeks, patients received open-label treatment with tocilizumab 8 mg per kg through 104 weeks or they had the option to continue their double-blind treatment if they maintained a greater than 70% improvement in swollen/tender joint count. Two pre-specified interim analyses at week 24 and week 52 were conducted. The primary endpoint at week 24 was the proportion of patients who achieved an ACR 20 response. At weeks 52 and 104, the primary endpoints were change from baseline in modified total Sharp-Genant score and the area under the curve (AUC) of the change from baseline in HAQ-DI score.

Study III (NCT00106548) evaluated patients with moderate to severe active rheumatoid arthritis who had an inadequate clinical response to MTX. Patients received tocilizumab 8 mg per kg, tocilizumab 4 mg per kg, or placebo every four weeks, in combination with MTX (10 to 25 mg weekly). The primary endpoint was the proportion of patients who achieved an ACR 20 response at week 24.

Study IV (NCT00106574) evaluated patients who had an inadequate response to their existing therapy, including one or more DMARDs. Patients received tocilizumab 8 mg per kg or placebo every four weeks, in combination with the stable DMARDs. The primary endpoint was the proportion of patients who achieved an ACR 20 response at week 24.

Study V (NCT00106522) evaluated patients with moderate to severe active rheumatoid arthritis who had an inadequate clinical response or were intolerant to one or more TNF antagonist therapies. The TNF antagonist therapy was discontinued prior to randomization. Patients received tocilizumab 8 mg per kg, tocilizumab 4 mg per kg, or placebo every four weeks, in combination with MTX (10 to 25 mg weekly). The primary endpoint was the proportion of patients who achieved an ACR 20 response at week 24.

Clinical Response

The percentages of intravenous tocilizumab-treated patients achieving ACR 20, 50 and 70 responses are shown in Table 4. In all intravenous studies, patients treated with 8 mg per kg tocilizumab had higher ACR 20, ACR 50, and ACR 70 response rates versus MTX- or placebo-treated patients at week 24.

During the 24 week controlled portions of Studies I to V, patients treated with tocilizumab at a dose of 4 mg per kg in patients with inadequate response to DMARDs or TNF antagonist therapy had lower response rates compared to patients treated with tocilizumab 8 mg per kg.

Table 4 Clinical Response at Weeks 24 and 52 in Active and Placebo Controlled Trials of Intravenous Tocilizumab (Percent of Patients)
Percent of Patients
 | Study I |  | Study II |  |  | Study III |  |  | Study IV |  | Study V
Response Rate | MTX | Tocilizumab 8 mg per kg | Placebo + MTX | Tocilizumab 4 mg per kg + MTX | Tocilizumab 8 mg per kg + MTX | Placebo + MTX | Tocilizumab 4 mg per kg + MTX | Tocilizumab 8 mg per kg + MTX | Placebo + DMARDs | Tocilizumab 8 mg per kg + DMARDs | Placebo + MTX | Tocilizumab 4 mg per kg + MTX | Tocilizumab 8 mg per kg + MTX
Response Rate | N=284 | N=286 | N=393 | N=399 | N=398 | N=204 | N=213 | N=205 | N=413 | N=803 | N=158 | N=161 | N=170
Response Rate |  | (95% CI)a |  | (95% CI)a | (95% CI)a |  | (95% CI)a | (95% CI)a |  | (95% CI)a |  | (95% CI)a | (95% CI)a
ACR 20
Week 24 | 53% | 70% | 27% | 51% | 56% | 27% | 48% | 59% | 24% | 61% | 10% | 30% | 50%
 |  | (0.11, 0.27) |  | (0.17, 0.29) | (0.23, 0.35) |  | (0.15, 0.32) | (0.23, 0.41) |  | (0.30, 0.40) |  | (0.15, 0.36) | (0.36, 0.56)
Week 52 | N/A | N/A | 25% | 47% | 56% | N/A | N/A | N/A | N/A | N/A | N/A | N/A | N/A
 |  |  |  | (0.15, 0.28) | (0.25, 0.38)
ACR 50
Week 24 | 34% | 44% | 10% | 25% | 32% | 11% | 32% | 44% | 9% | 38% | 4% | 17% | 29%
 |  | (0.04, 0.20) |  | (0.09, 0.20) | (0.16, 0.28) |  | (0.13, 0.29) | (0.25, 0.41) |  | (0.23, 0.33) |  | (0.05, 0.25) | (0.21, 0.41)
Week 52 | N/A | N/A | 10% | 29% | 36% | N/A | N/A | N/A | N/A | N/A | N/A | N/A | N/A
 |  |  |  | (0.14, 0.25) | (0.21, 0.32)
ACR 70
Week 24 | 15% | 28% | 2% | 11% | 13% | 2% | 12% | 22% | 3% | 21% | 1% | 5% | 12%
 |  | (0.07, 0.22) |  | (0.03, 0.13) | (0.05, 0.15) |  | (0.04, 0.18) | (0.12, 0.27) |  | (0.13, 0.21) |  | (-0.06, 0.14) | (0.03, 0.22)
Week 52 | N/A | N/A | 4% | 16% | 20% | N/A | N/A | N/A | N/A | N/A
 |  |  |  | (0.08, 0.17) | (0.12, 0.21) |  |  |  |  |  | N/A | N/A | N/A
Major Clinical Responses b
Week 52 | N/A | N/A | 1% | 4% | 7% | N/A | N/A | N/A | N/A | N/A | N/A | N/A | N/A
 |  |  |  | (0.01, 0.06) | (0.03, 0.09)
a CI: 95% confidence interval of the weighted difference to placebo adjusted for site (and disease duration for Study I only)
b Major clinical response is defined as achieving an ACR 70 response for a continuous 24 week period

In study II, a greater proportion of patients treated with 4 mg per kg and 8 mg per kg tocilizumab + MTX achieved a low level of disease activity as measured by a DAS 28-ESR less than 2.6 compared with placebo+ MTX treated patients at week 52. The proportion of tocilizumab-treated patients achieving DAS 28-ESR less than 2.6, and the number of residual active joints in these responders in Study II are shown in Table 5.

Table 5 Proportion of Patients with DAS28-ESR Less Than 2.6 with Number of Residual Active Joints in Trials of Intravenous Tocilizumab
Study II
 | Placebo + MTX N = 393 | Tocilizumab 4 mg per kg + MTX N = 399 | Tocilizumab 8 mg per kg + MTX N = 398
DAS28-ESR less than 2.6
Proportion of responders at week 52 (n) 95% confidence interval | 3% (12) | 18% (70) 0.10, 0.19 | 32% (127) 0.24, 0.34
Of responders, proportion with 0 active joints (n) | 33% (4) | 27% (19) | 21% (27)
Of responders, proportion with 1 active joint (n) | 8% (1) | 19% (13) | 13% (16)
Of responders, proportion with 2 active joints (n) | 25% (3) | 13% (9) | 20% (25)
Of responders, proportion with 3 or more active joints (n) | 33% (4) | 41% (29) | 47% (59)
*n denotes numerator of all the percentage. Denominator is the intent-to-treat population. Not all patients received DAS28 assessments at Week 52.

The results of the components of the ACR response criteria for Studies III and V are shown in Table 6. Similar results to Study III were observed in Studies I, II and IV.

Table 6 Components of ACR Response at Week 24 in Trials of Intravenous Tocilizumab
 | Study III |  |  |  |  |  | Study V
 | Tocilizumab 4 mg per kg + MTX N=213 |  | Tocilizumab 8 mg per kg + MTX N=205 |  | Placebo + MTX N=204 |  | Tocilizumab 4 mg per kg + MTX N=161 |  | Tocilizumab 8 mg per kg + MTX N=170 |  | Placebo + MTX N=158
Component (mean) | Baseline | Week 24a | Baseline | Week 24 a | Baseline | Week 24 | Baseline | Week 24 a | Baseline | Week 24 a | Baseline | Week 24
Number of | 33 | 19 | 32 | 14.5 | 33 | 25 | 31 | 21 | 32 | 17 | 30 | 30
tender joints | 33 | -7.0 | 32 | -9.6 | 33 | 25 | 31 | -10.8 | 32 | -15.1 | 30 | 30
(0-68) | 33 | (-10.0, -4.1) | 32 | (-12.6, -6.7) | 33 | 25 | 31 | (-14.6, -7.1) | 32 | (-18.8, -11.4) | 30 | 30
Number of | 20 | 10 | 19.5 | 8 | 21 | 15 | 19.5 | 13 | 19 | 11 | 19 | 18
swollen | 20 | -4.2 | 19.5 | -6.2 | 21 | 15 | 19.5 | -6.2 | 19 | -7.2 | 19 | 18
joints (0-66) | 20 | (-6.1, -2.3) | 19.5 | (-8.1, -4.2) | 21 | 15 | 19.5 | (-9.0, -3.5) | 19 | (-9.9, -4.5) | 19 | 18
Pain b | 61 | 33 -11.0 | 60 | 30 -15.8 | 57 | 43 | 63.5 | 43 -12.4 | 65 | 33 -23.9 | 64 | 48
Pain b | 61 | (-17.0, -5.0) | 60 | (-21.7, -9.9) | 57 | 43 | 63.5 | (-22.1, -2.1) | 65 | (-33.7, -14.1) | 64 | 48
Patient | 66 | 34 | 65 | 31 | 64 | 45 | 70 | 46 | 70 | 36 | 71 | 51
global | 66 | -10.9 | 65 | -14.9 | 64 | 45 | 70 | -10.0 | 70 | -17.4 | 71 | 51
Assessment b | 66 | (-17.1, -4.8) | 65 | (-20.9, -8.9) | 64 | 45 | 70 | (-20.3, 0.3) | 70 | (-27.8, -7.0) | 71 | 51
Physician | 64 | 26 | 64 | 23 | 64 | 32 | 66.5 | 39 | 66 | 28 | 67.5 | 43
global | 64 | -5.6 | 64 | -9.0 | 64 | 32 | 66.5 | -10.5 | 66 | -18.2 | 67.5 | 43
Assessment b | 64 | (-10.5, -0.8) | 64 | (-13.8, -4.2) | 64 | 32 | 66.5 | (-18.6, -2.5) | 66 | (-26.3, -10.0) | 67.5 | 43
Disability | 1.64 | 1.01 | 1.55 | 0.96 | 1.55 | 1.21 | 1.67 | 1.39 | 1.75 | 1.34 | 1.70 | 1.58
index | 1.64 | -0.18 | 1.55 | -0.21 | 1.55 | 1.21 | 1.67 | -0.25 | 1.75 | -0.34 | 1.70 | 1.58
(HAQ)c | 1.64 | (-0.34, -0.02) | 1.55 | (-0.37, -0.05) | 1.55 | 1.21 | 1.67 | (-0.42, -0.09) | 1.75 | (-0.51, -0.17) | 1.70 | 1.58
CRP (mg per | 2.79 | 1.17; -1.30 | 2.61 | 0.25 -2.156 | 2.36 | 1.89 | 3.11 | 1.77; -1.34 | 2.80 | 0.28; -2.52 | 3.705 | 3.06
dL) | 2.79 | 1.17; -1.30 | 2.61 | 0.25 -2.156 | 2.36 | 1.89 | 3.11 | 1.77; -1.34 | 2.80 | 0.28; -2.52 | 3.705 | 3.06
dL) | (-2.0, -0.59) | 1.17; -1.30 | (-2.86, -1.46) | 0.25 -2.156 | (-2.5, -0.15) | 1.89 | 3.11 | 1.77; -1.34 | (-3.72, -1.32) | 0.28; -2.52 | 3.705 | 3.06
a Data shown is mean at week 24, difference in adjusted mean change from baseline compared with placebo + MTX at week 24 and 95% confidence interval for that difference
b Visual analog scale: 0 = best, 100 = worst
c Health Assessment Questionnaire: 0 = best, 3 = worst; 20 questions; 8 categories: dressing and grooming, arising, eating, walking, hygiene, reach, grip, and activities

The percent of ACR 20 responders by visit for Study III is shown in Figure 1. Similar response curves were observed in studies I, II, IV, and V.

Figure 1 Percent of ACR 20 Responders by Visit for Study III (Inadequate Response to MTX)*

*The same patients may not have responded at each timepoint.

Radiographic Response

In Study II, structural joint damage was assessed radiographically and expressed as change in total Sharp-Genant score and its components, the erosion score and joint space narrowing score. Radiographs of hands/wrists and forefeet were obtained at baseline, 24 weeks, 52 weeks, and 104 weeks and scored by readers unaware of treatments group and visit number. The results from baseline to week 52 are shown in Table 7. Tocilizumab 4 mg per kg slowed (less than 75% inhibition compared to the control group) and tocilizumab 8 mg per kg inhibited (at least 75% inhibition compared to the control group) the progression of structural damage compared to placebo plus MTX at week 52.

Table 7 Mean Radiographic Change from Baseline to Week 52 in Study II
 | Placebo + MTX | Tocilizumab 4 mg per kg + MTX | Tocilizumab 8 mg per kg + MTX
 | N=294 | N=343 | N=353
Week 52*
Total Sharp-Genant Score, Mean (SD) | 1.17 (3.14) | 0.33 (1.30) | 0.25 (0.98)
Adjusted Mean difference** (95%CI) |  | -0.83 (-1.13, -0.52) | -0.90 (-1.20, -0.59)
Erosion Score, Mean (SD) | 0.76 (2.14) | 0.20 (0.83) | 0.15 (0.77)
Adjusted Mean difference** (95%CI) |  | -0.55 (-0.76, -0.34) | -0.60 (-0.80, -0.39)
Joint Space Narrowing Score, Mean (SD) | 0.41 (1.71) | 0.13 (0.72) | 0.10 (0.49)
Adjusted Mean difference** (95%CI) |  | -0.28 (-0.44, -0.11) | -0.30 (-0.46, -0.14)
* Week 52 analysis employs linearly extrapolated data for patients after escape, withdrawal, or loss to follow up.
** Difference between the adjusted means (tocilizumab + MTX – Placebo + MTX) SD = standard deviation

The mean change from baseline to week 104 in Total Sharp-Genant Score for the tocilizumab 4 mg per kg groups was 0.47 (SD = 1.47) and for the 8 mg per kg groups was 0.34 (SD = 1.24). By the week 104, most patients in the control (placebo + MTX) group had crossed over to active treatment, and results are therefore not included for comparison. Patients in the active groups may have crossed over to the alternate active dose group, and results are reported per original randomized dose group.

In the placebo group, 66% of patients experienced no radiographic progression (Total Sharp-Genant Score change ≤ 0) at week 52 compared to 78% and 83% in the tocilizumab 4 mg per kg and 8 mg per kg, respectively. Following 104 weeks of treatment, 75% and 83% of patients initially randomized to tocilizumab 4 mg per kg and 8 mg per kg, respectively, experienced no progression of structural damage compared to 66% of placebo treated patients.

Health Related Outcomes

In Study II, physical function and disability were assessed using the Health Assessment Questionnaire Disability Index (HAQ-DI). Both dosing groups of tocilizumab demonstrated a greater improvement compared to the placebo group in the AUC of change from baseline in the HAQ-DI through week 52. The mean change from baseline to week 52 in HAQ-DI was 0.6, 0.5, and 0.4 for tocilizumab 8 mg per kg, tocilizumab 4 mg per kg, and placebo treatment groups, respectively. Sixty-three percent (63%) and sixty percent (60%) of patients in the tocilizumab 8 mg per kg and tocilizumab 4 mg per kg treatment groups, respectively, achieved a clinically relevant improvement in HAQ-DI (change from baseline of ≥ 0.3 units) at week 52 compared to 53% in the placebo treatment group.

Other Health-Related Outcomes

General health status was assessed by the Short Form Health Survey (SF-36) in Studies I – V. Patients receiving tocilizumab demonstrated greater improvement from baseline compared to placebo in the Physical Component Summary (PCS), Mental Component Summary (MCS), and in all 8 domains of the SF-36.

Cardiovascular Outcomes

Study WA25204 (NCT01331837) was a randomized, open-label (sponsor-blinded), 2-arm parallel-group, multicenter, non-inferiority, cardiovascular (CV) outcomes trial in patients with a diagnosis of moderate to severe RA. This CV safety study was designed to exclude a moderate increase in CV risk in patients treated with tocilizumab compared with a TNF inhibitor standard of care (etanercept).

The study included 3,080 seropositive RA patients with active disease and an inadequate response to non- biologic disease-modifying anti-rheumatic drugs, who were aged ≥50 years with at least one additional CV risk factor beyond RA. Patients were randomized 1:1 to IV tocilizumab 8 mg/kg Q4W or SC etanercept 50 mg QW and followed for an average of 3.2 years. The primary endpoint was the comparison of the time-to-first occurrence of any component of a composite of major adverse CV events (MACE; non-fatal myocardial infarction, non-fatal stroke, or CV death), with the final intent-to-treat analysis based on a total of 161 confirmed CV events (83/1538 [5.4%] for tocilizumab; 78/1542 [5.1%] for etanercept) reviewed by an independent and blinded adjudication committee.

Non-inferiority of tocilizumab to etanercept for cardiovascular risk was determined by excluding >80% relative increase in the risk of MACE. The estimated hazard ratio (HR) for the risk of MACE comparing tocilizumab to etanercept was 1.05; 95% CI (0.77, 1.43).

14.2 Rheumatoid Arthritis – Subcutaneous Administration

The efficacy and safety of subcutaneously administered tocilizumab was assessed in two double-blind, controlled, multicenter studies in patients with active RA. One study, SC-I (NCT01194414), was a non-inferiority study that compared the efficacy and safety of tocilizumab 162 mg administered every week subcutaneously to 8 mg per kg intravenously every four weeks. The second study, SC-II (NCT01232569), was a placebo-controlled superiority study that evaluated the safety and efficacy of tocilizumab 162 mg administered every other week subcutaneously to placebo. Both SC-I and SC-II required patients to be >18 years of age with moderate to severe active rheumatoid arthritis diagnosed according to ACR criteria who had at least 4 tender and 4 swollen joints at baseline (SC-I) or at least 8 tender and 6 swollen joints at baseline (SC-II), and an inadequate response to their existing DMARD therapy, where approximately 20% also had a history of inadequate response to at least one TNF inhibitor. All patients in both SC studies received background non-biologic DMARD(s).

In SC-I, 1262 patients were randomized 1:1 to receive tocilizumab-SC 162 mg every week or intravenous tocilizumab 8 mg/kg every four weeks in combination with DMARD(s). In SC-II, 656 patients were randomized 2:1 to tocilizumab-SC 162 mg every other week or placebo, in combination with DMARD(s). The primary endpoint in both studies was the proportion of patients who achieved an ACR20 response at Week 24.

The clinical response to 24 weeks of tocilizumab-SC therapy is shown in Table 8. In SC-I, the primary outcome measure was ACR20 at Week 24. The pre-specified non-inferiority margin was a treatment difference of 12%. The study demonstrated non-inferiority of tocilizumab with respect to ACR20 at Week 24; ACR50, ACR70, and DAS28 responses are also shown in Table 8. In SC-II, a greater portion of patients treated with tocilizumab 162 mg subcutaneously every other week achieved ACR20, ACR50, and ACR70 responses compared to placebo-treated patients (Table 8). Further, a greater proportion of patients treated with tocilizumab 162 mg subcutaneously every other week achieved a low level of disease activity as measured by a DAS28-ESR less than 2.6 at Week 24 compared to those treated with placebo (Table 8).

Table 8 Clinical Response at Week 24 in Trials of Subcutaneous Tocilizumab (Percent of Patients)
 | SC-Ia |  | SC-IIb
 | TCZ SC 162 mg every week + DMARD | TCZ IV 8mg/kg + DMARD | TCZ SC 162 mg every other week + DMARD | Placebo + DMARD
 | N=558 | N=537 | N=437 | N=219
ACR20
Week 24 | 69% | 73.4% | 61% | 32%
Weighted difference (95% CI) | -4% (-9.2, 1.2) |  | 30% (22.0, 37.0)
ACR50
Week 24 | 47% | 49% | 40% | 12%
Weighted difference (95% CI) | -2% (-7.5, 4.0) |  | 28% (21.5, 34.4)
ACR70
Week 24 | 24% | 28% | 20% | 5%
Weighted difference (95% CI) | -4% (-9.0, 1.3) |  | 15% (9.8, 19.9)
Change in DAS28 [Adjusted mean]
Week 24 | -3.5 | -3.5 | -3.1 | -1.7
Adjusted mean difference (95% CI) | 0 (-0.2, 0.1) |  | -1.4 (-1.7; -1.1)
DAS28 < 2.6
Week 24 | 38.4% | 36.9% | 32.0% | 4.0%
Weighted difference (95% CI) | 0.9 (-5.0, 6.8) |  | 28.6 (22.0, 35.2)
TCZ = tocilizumab
a Per Protocol Population
b Intent To Treat Population

The results of the components of the ACR response criteria and the percent of ACR20 responders by visit for tocilizumab-SC in Studies SC-I and SC-II were consistent with those observed for tocilizumab-IV.

Radiographic Response

In study SC-II, the progression of structural joint damage was assessed radiographically and expressed as a change from baseline in the van der Heijde modified total Sharp score (mTSS). At week 24, significantly less radiographic progression was observed in patients receiving tocilizumab-SC every other week plus DMARD(s) compared to placebo plus DMARD(s); mean change from baseline in mTSS of 0.62 vs. 1.23, respectively, with an adjusted mean difference of -0.60 (-1.1, -0.1). These results are consistent with those observed in patients treated with intravenous tocilizumab.

Health Related Outcomes

In studies SC-I and SC-II, the mean decrease from baseline to week 24 in HAQ-DI was 0.6, 0.6, 0.4 and 0.3, and the proportion of patients who achieved a clinically relevant improvement in HAQ-DI (change from baseline of ≥ 0.3 units) was 65%, 67%, 58% and 47%, for the subcutaneous every week, intravenous 8 mg/kg, subcutaneous every other week, and placebo treatment groups, respectively.

Other Health-Related Outcomes

General health status was assessed by the SF-36 in Studies SC-I and SC-II. In Study SC-II, patients receiving tocilizumab every other week demonstrated greater improvement from baseline compared to placebo in the PCS, MCS, and in all 8 domains of the SF-36. In Study SC-I, improvements in these scores were similar between tocilizumab-SC every week and tocilizumab-IV 8 mg/kg.

14.3 Giant Cell Arteritis – Subcutaneous Administration

The efficacy and safety of subcutaneously administered tocilizumab was assessed in a single, randomized, double-blind, multicenter study in patients with active GCA. In Study WA28119 (NCT01791153), 251 screened patients with new-onset or relapsing GCA were randomized to one of four treatment arms. Two subcutaneous doses of tocilizumab (162 mg every week and 162 mg every other week) were compared to two different placebo control groups (pre-specified prednisone-taper regimen over 26 weeks and 52 weeks) randomized 2:1:1:1. The study consisted of a 52-week blinded period, followed by a 104-week open-label extension.

All patients received background glucocorticoid (prednisone) therapy. Each of the tocilizumab-treated groups and one of the placebo-treated groups followed a pre-specified prednisone-taper regimen with the aim to reach 0 mg by 26 weeks, while the second placebo-treated group followed a pre-specified prednisone-taper regimen with the aim to reach 0 mg by 52 weeks designed to be more in keeping with standard practice.

The primary efficacy endpoint was the proportion of patients achieving sustained remission from Week 12 through Week 52. Sustained remission was defined by a patient attaining a sustained (1) absence of GCA signs and symptoms from Week 12 through Week 52, (2) normalization of erythrocyte sedimentation rate (ESR) (to < 30 mm/hr without an elevation to ≥ 30 mm/hr attributable to GCA) from Week 12 through Week 52, (3) normalization of C-reactive protein (CRP) (to < 1 mg/dL, with an absence of successive elevations to ≥ 1mg/dL) from Week 12 through Week 52, and (4) successful adherence to the prednisone taper defined by not more than 100 mg of excess prednisone from Week 12 through Week 52. Tocilizumab 162 mg weekly and 162 mg every other week + 26 weeks prednisone taper both showed superiority in achieving sustained remission from Week 12 through Week 52 compared with placebo + 26 weeks prednisone taper (Table 9). Both tocilizumab treatment arms also showed superiority compared to the placebo + 52 weeks prednisone taper (Table 9).

Table 9 Efficacy Results from Study WA28119
 | PBO + 26 weeks prednisone taper N=50 | PBO + 52 weeks prednisone taper N=51 | TCZ 162mg SC QW + 26 weeks prednisone taper N=100 | TCZ 162 mg SC Q2W + 26 weeks prednisone taper N=49
Sustained remission a
Responders, n (%) | 7 (14.0%) | 9 (17.6%) | 56 (56.0%) | 26 (53.1%)
Unadjusted difference in proportions vs PBO + 26 weeks taper (99.5% CI) | N/A | N/A | 42.0% (18.0, 66.0) | 39.1% (12.5, 65.7)
Unadjusted difference in proportions vs PBO + 52 weeks taper (99.5% CI) | N/A | N/A | 38.4% (14.4, 62.3) | 35.4% (8.6, 62.2)
Components of Sustained Remission
Sustained absence of GCA signs and symptomsb, n (%) Sustained ESR<30 mm/hrc, n (%) Sustained CRP normalizationd, n (%) Successful prednisone taperinge, n (%) | 20 (40.0%) 20 (40.0%) 17 (34.0%) 10 (20.0%) | 23 (45.1%) 22 (43.1%) 13 (25.5%) 20 (39.2%) | 69 (69.0%) 83 (83.0%) 72 (72.0%) 60 (60.0%) | 28 (57.1%) 37 (75.5%) 34 (69.4%) 28 (57.1%)
a Sustained remission was achieved by a patient meeting all of the following components: absence of GCA signs and symptomsb, normalization of ESRc, normalization of CRPd and adherence to the prednisone taper regimene.
b Patients who did not have any signs or symptoms of GCA recorded from Week 12 up to Week 52.
c Patients who did not have an elevated ESR ≥30 mm/hr which was classified as attributed to GCA from Week 12 up to Week 52.
d Patients who did not have two or more consecutive CRP records of ≥ 1mg/dL from Week 12 up to Week 52.
e Patients who did not enter escape therapy and received ≤ 100mg of additional concomitant prednisone from Week 12 up to Week 52.

Patients not completing the study to week 52 were classified as non-responders in the primary and key secondary analysis: PBO+26: 6 (12.0%), PBO+52: 5 (9.8%), TCZ QW: 15 (15.0%), TCZ Q2W: 9 (18.4%).

CRP = C-reactive protein

ESR = erythrocyte sedimentation rate

PBO = placebo

Q2W = every other week dose

QW = every week dose

TCZ = tocilizumab

The estimated annual cumulative prednisone dose was lower in the two tocilizumab dose groups (medians of 1887 mg and 2207 mg on tocilizumab QW and Q2W, respectively) relative to the placebo arms (medians of 3804 mg and 3902 mg on placebo + 26 weeks prednisone and placebo + 52 weeks prednisone taper, respectively).

14.4 Giant Cell Arteritis – Intravenous Administration

Intravenously administered tocilizumab in patients with GCA was assessed in WP41152 (NCT03923738), an open-label PK-PD and safety study to determine the appropriate intravenous dose of tocilizumab that achieved comparable PK-PD profiles to the tocilizumab-SC regimen.

At enrollment, all patients (n=24) were in remission on tocilizumab-IV. In Period 1, all patients received open label tocilizumab-IV 7 mg/kg every 4 weeks for 20 weeks. Patients who completed Period 1 and remained in remission (n=22) were eligible to enter Period 2, and received open-label tocilizumab-IV 6 mg/kg every 4 weeks for 20 weeks.

The efficacy of intravenous tocilizumab 6 mg/kg in adult patients with GCA is based on pharmacokinetic exposure and extrapolation to the efficacy established for subcutaneous tocilizumab in patients with GCA [see Clinical Pharmacology (12.3) and Clinical Studies (14.3)].

14.5 Polyarticular Juvenile Idiopathic Arthritis – Intravenous Administration

The efficacy of tocilizumab was assessed in a three-part study, WA19977 (NCT00988221), including an open- label extension in children 2 to 17 years of age with active polyarticular juvenile idiopathic arthritis (PJIA), who had an inadequate response to methotrexate or inability to tolerate methotrexate. Patients had at least 6 months of active disease (mean disease duration of 4.2 ± 3.7 years), with at least five joints with active arthritis (swollen or limitation of movement accompanied by pain and/or tenderness) and/or at least 3 active joints having limitation of motion (mean, 20 ± 14 active joints). The patients treated had subtypes of JIA that at disease onset included Rheumatoid Factor Positive or Negative Polyarticular JIA, or Extended Oligoarticular JIA. Treatment with a stable dose of methotrexate was permitted but was not required during the study. Concurrent use of disease modifying antirheumatic drugs (DMARDs), other than methotrexate, or other biologics (e.g., TNF antagonists or T cell costimulation modulator) were not permitted in the study.

Part I consisted of a 16-week active tocilizumab treatment lead-in period (n=188) followed by Part II, a 24-week randomized double-blind placebo-controlled withdrawal period, followed by Part III, a 64-week open-label period. Eligible patients weighing at or above 30 kg received tocilizumab at 8 mg/kg intravenously once every four weeks. Patients weighing less than 30 kg were randomized 1:1 to receive either tocilizumab 8 mg/kg or 10 mg/kg intravenously every four weeks. At the conclusion of the open-label Part I, 91% of patients taking background MTX in addition to tocilizumab and 83% of patients on tocilizumab monotherapy achieved an ACR 30 response at week 16 compared to baseline and entered the blinded withdrawal period (Part II) of the study.

The proportions of patients with JIA ACR 50/70 responses in Part I were 84.0%, and 64%, respectively for patients taking background MTX in addition to tocilizumab and 80% and 55% respectively for patients on tocilizumab monotherapy.

In Part II, patients (ITT, n=163) were randomized to tocilizumab (same dose received in Part I) or placebo in a 1:1 ratio that was stratified by concurrent methotrexate use and concurrent corticosteroid use. Each patient continued in Part II of the study until Week 40 or until the patient satisfied JIA ACR 30 flare criteria (relative to Week 16) and qualified for escape.

The primary endpoint was the proportion of patients with a JIA ACR 30 flare at week 40 relative to week 16. JIA ACR 30 flare was defined as 3 or more of the 6 core outcome variables worsening by at least 30% with no more than 1 of the remaining variables improving by more than 30% relative to Week 16.

Tocilizumab treated patients experienced significantly fewer disease flares compared to placebo-treated patients (26% [21/82] versus 48% [39/81]; adjusted difference in proportions -21%, 95% CI: -35%, -8%).

During the withdrawal phase (Part II), more patients treated with tocilizumab showed JIA ACR 30/50/70 responses at Week 40 compared to patients withdrawn to placebo.

14.6 Polyarticular Juvenile Idiopathic Arthritis – Subcutaneous Administration

Subcutaneously administered tocilizumab in pediatric patients with polyarticular juvenile idiopathic arthritis (PJIA) was assessed in WA28117 (NCT01904279), a 52-week, open-label, multicenter, PK-PD and safety study to determine the appropriate subcutaneous dose of tocilizumab that achieved comparable PK/PD profiles to the tocilizumab-IV regimen. PJIA patients aged 1 to 17 years with an inadequate response or inability to tolerate MTX, including patients with well-controlled disease on treatment with tocilizumab-IV and tocilizumab-naïve patients with active disease, were treated with subcutaneous tocilizumab based on body weight.

Patients weighing at or above 30 kg (n = 25) were treated with 162 mg of tocilizumab-SC every 2 weeks and patients weighing less than 30 kg (n = 27) received 162 mg of tocilizumab-SC every 3 weeks for 52 weeks. Of these 52 patients, 37 (71%) were naïve to tocilizumab and 15 (29%) had been receiving tocilizumab-IV and switched to tocilizumab-SC at baseline.

The efficacy of subcutaneous tocilizumab in children 2 to 17 years of age is based on pharmacokinetic exposure and extrapolation of the established efficacy of intravenous tocilizumab in polyarticular JIA patients and subcutaneous tocilizumab in patients with RA [see Clinical Pharmacology (12.3) and Clinical Studies (14.2 and 14.6)].

14.7 Systemic Juvenile Idiopathic Arthritis - Intravenous Administration

The efficacy of tocilizumab for the treatment of active SJIA was assessed in WA18221 (NCT00642460), a 12-week randomized, double blind, placebo-controlled, parallel group, 2-arm study. Patients treated with or without MTX, were randomized (tocilizumab:placebo = 2:1) to one of two treatment groups: 75 patients received tocilizumab infusions every two weeks at either 8 mg per kg for patients at or above 30 kg or 12 mg per kg for patients less than 30 kg and 37 were randomized to receive placebo infusions every two weeks. Corticosteroid tapering could occur from week six for patients who achieved a JIA ACR 70 response. After 12 weeks or at the time of escape, due to disease worsening, patients were treated with tocilizumab in the open-label extension phase at weight appropriate dosing.

The primary endpoint was the proportion of patients with at least 30% improvement in JIA ACR core set (JIA ACR 30 response) at Week 12 and absence of fever (no temperature at or above 37.5°C in the preceding 7 days). JIA ACR (American College of Rheumatology) responses are defined as the percentage improvement (e.g., 30%, 50%, 70%) in 3 of any 6 core outcome variables compared to baseline, with worsening in no more than 1 of the remaining variables by 30% or more.

Core outcome variables consist of physician global assessment, parent per patient global assessment, number of joints with active arthritis, number of joints with limitation of movement, erythrocyte sedimentation rate (ESR), and functional ability (childhood health assessment questionnaire-CHAQ).

Primary endpoint result and JIA ACR response rates at Week 12 are shown in Table 10.

Table 10 Efficacy Findings at Week 12
 | Tocilizumab N=75 | Placebo N=37
Primary Endpoint: JIA ACR 30 response + absence of fever
Responders | 85% | 24%
Weighted difference (95% CI) | 62 (45, 78) | -
JIA ACR Response Rates at Week 12
JIA ACR 30
Responders Weighted difference a (95% CI) b | 91% 67 (51, 83) | 24% -
JIA ACR 50
Responders Weighted difference a (95% CI) b | 85% 74 (58, 90) | 11% -
JIA ACR 70
Responders Weighted difference a (95% CI) b | 71% 63 (46, 80) | 8% -
aThe weighted difference is the difference between the tocilizumab and Placebo response rates, adjusted for the stratification factors (weight, disease duration, background oral corticosteroid dose and background methotrexate use).
b CI: confidence interval of the weighted difference.

The treatment effect of tocilizumab was consistent across all components of the JIA ACR response core variables. JIA ACR scores and absence of fever responses in the open label extension were consistent with the controlled portion of the study (data available through 44 weeks).

Systemic Features

Of patients with fever or rash at baseline, those treated with tocilizumab had fewer systemic features; 35 out of 41 (85%) became fever free (no temperature recording at or above 37.5°C in the preceding 14 days) compared to 5 out of 24 (21%) of placebo-treated patients, and 14 out of 22 (64%) became free of rash compared to 2 out of 18 (11%) of placebo-treated patients. Responses were consistent in the open label extension (data available through 44 weeks).

Corticosteroid Tapering

Of the patients receiving oral corticosteroids at baseline, 8 out of 31 (26%) placebo and 48 out of 70 (69%), tocilizumab patients achieved a JIA ACR 70 response at week 6 or 8 enabling corticosteroid dose reduction. Seventeen (24%) tocilizumab patients versus 1 (3%) placebo patient were able to reduce the dose of corticosteroid by at least 20% without experiencing a subsequent JIA ACR 30 flare or occurrence of systemic symptoms to week 12. In the open label portion of the study, by week 44, there were 44 out of 103 (43%) tocilizumab patients off oral corticosteroids. Of these 44 patients 50% were off corticosteroids 18 weeks or more.

Health Related Outcomes

Physical function and disability were assessed using the Childhood Health Assessment Questionnaire Disability Index (CHAQ-DI). Seventy-seven percent (58 out of 75) of patients in the tocilizumab treatment group achieved a minimal clinically important improvement in CHAQ-DI (change from baseline of ≥ 0.13 units) at week 12 compared to 19% (7 out of 37) in the placebo treatment group.

14.8 Systemic Juvenile Idiopathic Arthritis - Subcutaneous Administration

Subcutaneously administered tocilizumab in pediatric patients with systemic juvenile idiopathic arthritis (SJIA) was assessed in WA28118 (NCT01904292), a 52-week, open-label, multicenter, PK-PD and safety study to determine the appropriate subcutaneous dose of tocilizumab that achieved comparable PK/PD profiles to the tocilizumab-IV regimen.

Eligible patients received tocilizumab subcutaneously dosed according to body weight, with patients weighing at or above 30 kg (n = 26) dosed with 162 mg of tocilizumab every week and patients weighing below 30 kg (n = 25) dosed with 162 mg of tocilizumab every 10 days (n=8) or every 2 weeks (n=17) for 52 weeks. Of these 51 patients, 26 (51%) were naïve to subcutaneous tocilizumab and 25 (49%) had been receiving tocilizumab intravenously and switched to subcutaneous tocilizumab at baseline.

The efficacy of subcutaneous tocilizumab in children 2 to 17 years of age is based on pharmacokinetic exposure and extrapolation of the established efficacy of intravenous tocilizumab in systemic JIA patients [see Clinical Pharmacology (12.3) and Clinical Studies (14.8)].

14.9 Cytokine Release Syndrome – Intravenous Administration

The efficacy of tocilizumab for the treatment of CRS was assessed in a retrospective analysis of pooled outcome data from clinical trials of CAR T-cell therapies for hematological malignancies. Evaluable patients had been treated with tocilizumab 8 mg/kg (12 mg/kg for patients < 30 kg) with or without additional high-dose corticosteroids for severe or life-threatening CRS; only the first episode of CRS was included in the analysis. The study population included 24 males and 21 females (total 45 patients) of median age 12 years (range, 3–23 years); 82% were Caucasian. The median time from start of CRS to first dose of tocilizumab was 4 days (range, 0-18 days). Resolution of CRS was defined as lack of fever and off vasopressors for at least 24 hours. Patients were considered responders if CRS resolved within 14 days of the first dose of tocilizumab, if no more than 2 doses of tocilizumab were needed, and if no drugs other than tocilizumab and corticosteroids were used for treatment. Thirty-one patients (69%; 95% CI: 53%–82%) achieved a response. Achievement of resolution of CRS within 14 days was confirmed in a second study using an independent cohort that included 15 patients (range: 9–75 years old) with CAR T cell-induced CRS.

14.10 COVID-19 – Intravenous Administration

The efficacy of tocilizumab for the treatment of COVID-19 was based on RECOVERY (NCT04381936), a randomized, controlled, open-label, platform study, and supported by the results from EMPACTA (NCT04372186), a randomized, double-blind, placebo-controlled study. Results of two other randomized, double-blind, placebo-controlled studies, COVACTA (NCT04320615) and REMDACTA (NCT04409262), which evaluated the efficacy of tocilizumab for the treatment of COVID-19 are also summarized.

RECOVERY (Randomised Evaluation of COVID-19 Therapy) Collaborative Group Study in Hospitalized Adults Diagnosed with COVID-19

RECOVERY was a randomized, controlled, open-label, multicenter platform study conducted in the United Kingdom to evaluate the efficacy and safety of potential treatments in hospitalized adult patients with severe COVID-19 pneumonia. Eligible patients for the tocilizumab portion of the study had clinically suspected or laboratory-confirmed SARS-CoV-2 infection and no medical contraindications to any of the treatments and had clinical evidence of progressive COVID-19 (defined as oxygen saturation <92% on room air or receiving oxygen therapy, and CRP ≥75 mg/L). Patients were then randomized to receive either standard of care (SoC) or intravenous tocilizumab at a weight-tiered dosing comparable to the recommended dosage [see Clinical Pharmacology (12.3)] in addition to SoC.

Efficacy analyses were performed in the intent-to-treat (ITT) population comprising 4116 adult patients who were randomized to the tocilizumab + SoC arm (n=2022) or to the SoC arm (n=2094). The mean age of participants was 64 years (range: 20 to 101), and patients were 67% male, 76% White, 11% Asian, 3% Black or African American, and 1% mixed race. At baseline, 0.2% of patients were not on supplemental oxygen, 45% of patients required low flow oxygen, 41% of patients required non-invasive ventilation or high-flow oxygen, and 14% of patients required invasive mechanical ventilation; 82% of patients were reported to be receiving systemic corticosteroids. The primary efficacy endpoint was time to death through Day 28. The results for the overall population and the subgroups of patients who were or were not receiving systemic corticosteroids at time of randomization are summarized in Table 11.

Table 11 Mortality through Day 28 in RECOVERY
 | Tocilizumab +SoC N=2022 n (%)^1 | SoC N=2094 n (%)^1 | Hazard Ratio (95% CI) | Risk Difference (95% CI)
Mortality | 621 (30.7%) | 729 (34.9%) | 0.85 (0.76, 0.94) p= 0.00281 | -4.1% (-7.0, -1.3)
By baseline receipt of corticosteroid use
Mortality for patients receiving systemic corticosteroids at randomization^2 | 482/1664 (29.0%) | 600/1721 (34.9%) | 0.79 (0.70, 0.89) | -5.9% (-9.1, -2.8)
Mortality for patients not receiving systemic corticosteroids at randomization^2 | 139/357 (39.0%) | 127/367 (34.6%) | 1.16 (0.91, 1.48) | 4.4% (-2.6, 11.5)
^1 P-value reflects that the RECOVERY trial primary analysis results were statistically significant at the two-sided significance level of 𝛼 = 0.05.
^2 Probabilities of dying by Day 28 were estimated by the Kaplan-Meier method.

EMPACTA

EMPACTA was a randomized, double-blind, placebo-controlled, multicenter study to evaluate intravenous tocilizumab 8 mg/kg in combination with SoC in hospitalized, non-ventilated adult patients with COVID-19 pneumonia. Eligible patients were at least 18 years of age, had confirmed SARS-CoV-2 infection by a positive reverse-transcriptase polymerase chain reaction (RT-PCR) result, had pneumonia confirmed by radiography, and had SpO2 < 94% on ambient air.

Of the 389 patients randomized, efficacy analyses were performed in the modified intent-to-treat (mITT) population comprising 377 patients who were randomized and received study medication (249 in the tocilizumab arm; 128 in the placebo arm). The mean age of participants was 56 years (range: 20 to 95); 59% of patients were male, 56% were of Hispanic or Latino ethnicity, 53% were White, 20% were American Indian/Alaska Native, 15% were Black/African American and 2% were Asian. At baseline, 9% patients were not on supplemental oxygen, 64% patients required low flow oxygen, 27% patients required high-flow oxygen, and 73% were on corticosteroids.

The primary efficacy endpoint evaluated time to progression to mechanical ventilation or death through Day 28. The hazard ratio comparing tocilizumab to placebo was 0.56 (95% CI, 0.33 to 0.97), a statistically significant result (log-rank, p-value = 0.036). The cumulative proportion of patients who required mechanical ventilation or died by Day 28 was 12.0% (95% CI, 8.5% to 16.9%) in the tocilizumab arm and 19.3% (95% CI, 13.3% to 27.4%) in the placebo arm.

Mortality at Day 28 was 10.4% in the tocilizumab arm versus 8.6% in the placebo arm (weighted difference (tocilizumab arm - placebo arm): 2.0% [95% CI, -5.2% to 7.8%]).

COVACTA

COVACTA was a randomized, double-blind, placebo-controlled, multicenter study to evaluate intravenous tocilizumab 8 mg/kg in combination with SoC for the treatment of adult patients hospitalized with severe COVID-19 pneumonia. The study randomized 452 patients who were at least 18 years of age with confirmed SARS-CoV2 infection by a positive RT-PCR result, had pneumonia confirmed by radiography, and had oxygen saturation of 93% or lower on ambient air or a ratio of arterial oxygen partial pressure to fractional inspired oxygen of 300 mmHg or less. At baseline, 3% of patients were not on supplemental oxygen, 28% were on low flow oxygen, 30% were on non-invasive ventilation or high flow oxygen, 38% were on invasive mechanical ventilation, and 22% were on corticosteroids. The primary efficacy endpoint was clinical status on Day 28 assessed on a 7-category ordinal scale that ranged from “discharged” to “death.” There were no statistically significant differences observed in the distributions of clinical status on the 7-category ordinal scale at Day 28 when comparing the tocilizumab arm to the placebo arm.

Mortality at Day 28 was 19.7% in the tocilizumab arm versus 19.4% in the placebo arm (weighted difference (tocilizumab arm - placebo arm): 0.3% [95% CI, -7.6 to 8.2]).

REMDACTA

REMDACTA was a randomized, double-blind, placebo-controlled, multicenter study to evaluate intravenous tocilizumab 8 mg/kg in combination with intravenous remdesivir (RDV) 200 mg on Day 1 followed by 100 mg once daily for a total of 10 days in hospitalized patients with severe COVID-19 pneumonia. The study randomized 649 adult patients with SARS-CoV-2 infection confirmed by a positive polymerase chain reaction (PCR) result, pneumonia confirmed by radiography, and who required supplemental oxygen > 6 L/min to maintain SpO2 >93%. At baseline, 7% of patients were on low flow oxygen, 80% were on non-invasive ventilation or high flow oxygen, 14% were on invasive mechanical ventilation, and 84% were on corticosteroids.

The primary efficacy endpoint was time from randomization to hospital discharge or ‘ready for discharge’ up to Day 28. There was no statistically significant difference between the treatment arms with respect to time to hospital discharge or “ready for discharge” through Day 28.

Mortality at Day 28 was 18.1% in the tocilizumab + RDV arm versus 19.5% in the placebo +RDV arm (weighted difference (tocilizumab arm - placebo arm): -1.3% [95% CI, -7.8% to 5.2%]).

Mortality Across Studies in Patients Receiving Baseline Corticosteroids

A study-level meta-analysis was conducted on EMPACTA, COVACTA, REMDACTA and RECOVERY studies. For each of the four studies, the risk difference through Day 28 was estimated by the Kaplan-Meier method in the subgroup of patients receiving baseline corticosteroids, summarized in Figure 2. Patients from the RECOVERY trial represent 78.8% of the total sample size in this meta-analysis. The combined risk difference showed that tocilizumab treatment (n=2261) resulted in a 4.61% absolute reduction in the risk of death at Day 28 (risk difference=-4.6%; 95% CI: -7.3% to -1.9%) compared to SoC (n=2034).

Figure 2 Risk Differences Through Day 28 for Baseline Corticosteroid Use Subpopulation in RECOVERY, EMPACTA, COVACTA and REMDACTA studies

16 HOW SUPPLIED/STORAGE AND HANDLING

How Supplied:

TYENNE (tocilizumab-aazg) injection is a preservative-free, sterile clear and colorless to pale yellow solution. The following packaging configurations are available:

For Intravenous Infusion

TYENNE Single-Dose Vial

Each TYENNE carton contains one vial. Each vial is supplied as 80 mg/4 mL (20 mg/mL) (NDC 65219-590-04), 200 mg/10 mL (20 mg/mL) (NDC 65219-592-10), and 400 mg/20 mL (20 mg/mL) (NDC 65219-594-20) TYENNE solution for further dilution prior to intravenous infusion. The vial stopper is not made with natural rubber latex.

For Subcutaneous Injection

TYENNE Prefilled Syringe

Each TYENNE carton contains a single-dose prefilled syringe delivering 162 mg/0.9 mL of TYENNE. The syringe plunger stopper and needle cover are not made with natural rubber latex. The NDC number is 65219-586-04.

TYENNE Autoinjector

Each TYENNE carton contains a single-dose autoinjector delivering 162 mg/0.9 mL of TYENNE. The syringe plunger stopper and needle cover are not made with natural rubber latex. The NDC number is 65219-584-01.

Storage and Handling: Do not use beyond expiration date on the container, package, prefilled syringe, or autoinjector. TYENNE must be refrigerated at 36°F to 46°F (2ºC to 8ºC). Do not freeze. A single prefilled syringe (or autoinjector) may be stored at room temperature at or below 77°F (25°C) for a single period of up to 14 days. Protect the vials, syringes and autoinjectors from light by storage in the original package until time of use, and keep syringes and autoinjectors dry. Do not shake.

17 PATIENT COUNSELING INFORMATION

Advise the patient to read the FDA-approved patient labeling (Medication Guide and Instructions for Use).

- Serious Infections

Inform patients that TYENNE may lower their resistance to infections [see Warnings and Precautions (5.1)]. Instruct the patient of the importance of contacting their doctor immediately when symptoms suggesting infection appear in order to assure rapid evaluation and appropriate treatment.

- Gastrointestinal Perforation

Inform patients that some patients who have been treated with TYENNE have had serious side effects in the stomach and intestines [see Warnings and Precautions (5.2)]. Instruct the patient of the importance of contacting their doctor immediately when symptoms of fever, severe, persistent abdominal pain, and change in bowel habits appear to assure rapid evaluation and appropriate treatment.

- Hypersensitivity and Serious Allergic Reactions

Inform patients that some patients who have been treated with TYENNE have developed serious allergic reactions, including anaphylaxis, as well as serious skin reactions [see Warnings and Precautions (5.6)]. Advise patients to stop taking TYENNE and seek immediate medical attention if they experience any symptom of serious allergic reactions (including rash, hives, and swelling of the face, lips, tongue, and throat that may cause difficulty in breathing or swallowing).

Instruction on Injection Technique

Assess patient suitability for home use for subcutaneous injection. Perform the first injection under the supervision of a qualified healthcare professional. If a patient or caregiver is to administer subcutaneous TYENNE, instruct him/her in injection techniques and assess his/her ability to inject subcutaneously to ensure proper administration of subcutaneous TYENNE and the suitability for home use [See Instructions for Use].

Prior to use, remove the prefilled syringe (PFS) or autoinjector from the refrigerator and allow to sit at room temperature outside of the carton for 30 minutes (PFS) or 45 minutes (autoinjector), out of the reach of children.

Do not warm TYENNE in any other way.

Advise patients to consult their healthcare provider if the full dose is not received.

A puncture-resistant container for disposal of needles, syringes and autoinjectors should be used and should be kept out of the reach of children. Instruct patients or caregivers in the technique as well as proper needle, syringe and autoinjector disposal, and caution against reuse of these items.

Pregnancy

Inform female patients of reproductive potential that TYENNE may cause fetal harm and to inform their prescriber of a known or suspected pregnancy [see Use in Specific Populations (8.1)].

TYENNE (tocilizumab-aazg)

Manufactured by:
Fresenius Kabi USA, LLC
Lake Zurich, IL 60047, U.S.A.

U.S. License Number: 2146

Medication Guide
TYENNE® (tye en')
(tocilizumab-aazg)
injection for intravenous use
TYENNE® (tye en')
(tocilizumab-aazg)
injection for subcutaneous use

What is the most important information I should know about TYENNE?
TYENNE can cause serious side effects including:

1. Serious Infections. TYENNE is a medicine that affects your immune system. TYENNE can lower the ability of your immune system to fight infections. Some people have serious infections while taking TYENNE, including tuberculosis (TB), and infections caused by bacteria, fungi, or viruses that can spread throughout the body. Some people have died from these infections. Your healthcare provider should assess you for TB before starting TYENNE (except if you have COVID-19).

If you have COVID-19, your healthcare provider should monitor you for signs and symptoms of new infections during and after treatment with TYENNE.

Your healthcare provider should monitor you closely for signs and symptoms of TB during and after treatment with
TYENNE

- You should not start taking TYENNE if you have any kind of infection unless your healthcare provider says it is okay.

Before starting TYENNE, tell your healthcare provider if you:

- think you have an infection or have symptoms of an infection, with or without a fever, such as:

  - sweating or chills
  - shortness of breath
  - warm, red, or painful skin or sores on your body

  - feel very tired
  - muscle aches
  - blood in phlegm
  - diarrhea or stomach pain

  - cough
  - weight loss
  - burning when you urinate more often than normal

- are being treated for an infection.
- get a lot of infections or have infections that keep coming back.
- have diabetes, HIV, or a weak immune system. People with these conditions have a higher chance for infections.
- have TB or have been in close contact with someone with TB.
- live or have lived or have traveled to certain parts of the country (such as the Ohio and Mississippi River valleys and the Southwest) where there is an increased chance for getting certain kinds of fungal infections (histoplasmosis, coccidiomycosis, or blastomycosis). These infections may happen or become more severe if you use TYENNE. Ask your healthcare provider if you do not know if you have lived in an area where these infections are common.
- have or have had hepatitis B.

After starting TYENNE, call your healthcare provider right away if you have any symptoms of an infection. TYENNE can make you more likely to get infections or make worse any infection that you have.

2. Tears (perforation) of the stomach or intestines.
  1. Tell your healthcare provider if you have had diverticulitis (inflammation in parts of the large intestine) or ulcers in your stomach or intestines. Some people taking TYENNE get tears in their stomach or intestine. This happens most often in people who also take nonsteroidal anti-inflammatory drugs (NSAIDs), corticosteroids, or methotrexate.
  2. Tell your healthcare provider right away if you have fever and stomach-area pain that does not go away, and a change in your bowel habits.
3. Liver problems (Hepatotoxicity): Some people have experienced serious life-threatening liver problems, which required a liver transplant or led to death. Your healthcare provider may tell you to stop taking TYENNE if you develop new or worse liver problems during treatment with TYENNE. Tell your healthcare provider right away if you have any of the following symptoms:

  - feeling tired (fatigue)
  - lack of appetite for several days or longer (anorexia)
  - yellowing of your skin or the whites of your eyes (jaundice)
  - abdominal swelling and pain on the right side of your stomach-area
  - light colored stools

  - Weakness
  - nausea and vomiting
  - confusion
  - dark “tea-colored” urine

4. Changes in certain laboratory test results. Your healthcare provider should do blood tests before you start receiving TYENNE. If you have rheumatoid arthritis (RA) or giant cell arteritis (GCA) your healthcare provider should do blood tests every 4 to 8 weeks after you start receiving TYENNE for the first 6 months and then every 3 months after that. If you have polyarticular juvenile idiopathic arthritis (PJIA) you will have blood tests done every 4 to 8 weeks during treatment. If you have systemic juvenile idiopathic arthritis (SJIA) you will have blood tests done every 2 to 4 weeks during treatment. These blood tests are to check for the following side effects of TYENNE:
  1. low neutrophil count. Neutrophils are white blood cells that help the body fight off bacterial infections.
  2. low platelet count. Platelets are blood cells that help with blood clotting and stop bleeding.
  3. increase in certain liver function tests.
  4. increase in blood cholesterol levels. You may also have changes in other laboratory tests, such as your blood cholesterol levels. Your healthcare provider should do blood tests to check your cholesterol levels 4 to 8 weeks after you start receiving TYENNE.

Your healthcare provider will determine how often you will have follow-up blood tests. Make sure you get all your follow-up blood tests done as ordered by your healthcare provider.
You should not receive TYENNE if your neutrophil or platelet counts are too low, or your liver function tests are too high.
Your healthcare provider may stop your TYENNE treatment for a period of time or change your dose of medicine if needed because of changes in these blood test results.

5. Cancer. TYENNE may increase your risk of certain cancers by changing the way your immune system works. Tell your healthcare provider if you have ever had any type of cancer.

See “What are the possible side effects with TYENNE?” for more information about side effects.

What is TYENNE?
TYENNE is a prescription medicine called an Interleukin-6 (IL-6) receptor antagonist. TYENNE is used:

- To treat adults with moderately to severely active rheumatoid arthritis (RA), after at least one other medicine called a Disease-Modifying Anti-Rheumatic Drug (DMARD) has been used and did not work well.
- To treat adults with giant cell arteritis (GCA).
- To treat people with active PJIA ages 2 and above.
- To treat people with active SJIA ages 2 and above.
- To treat people age 2 years and above who experience severe or life-threatening Cytokine Release Syndrome (CRS) following chimeric antigen receptor (CAR) T cell treatment.
- To treat hospitalized adults with coronavirus disease 2019 (COVID-19) receiving systemic corticosteroids and requiring supplemental oxygen or mechanical ventilation.
- TYENNE is not approved for subcutaneous use in people with CRS or COVID-19.

It is not known if TYENNE is safe and effective in children with PJIA or SJIA or CRS under 2 years of age or in children with conditions other than PJIA or SJIA or CRS.

Do not take TYENNE: if you are allergic to tocilizumab products, or any of the ingredients in TYENNE. See the end of this Medication Guide for a complete list of ingredients in TYENNE.

Before you receive TYENNE, tell your healthcare provider about all of your medical conditions, including if you:

- have an infection. See “What is the most important information I should know about TYENNE?”
- have liver problems.
- have any stomach-area (abdominal) pain or been diagnosed with diverticulitis or ulcers in your stomach or intestines.
- have had a reaction to tocilizumab or any of the ingredients in TYENNE before.
- have or had a condition that affects your nervous system, such as multiple sclerosis.
- have recently received or are scheduled to receive a vaccine:
  - All vaccines should be brought up-to-date before starting TYENNE, unless urgent treatment initiation is required.
  - People who take TYENNE should not receive live vaccines.
  - People taking TYENNE can receive non-live vaccines.
- plan to have surgery or a medical procedure.
- are pregnant or plan to become pregnant or are pregnant. TYENNE may harm your unborn baby. Tell your healthcare provider if you become pregnant or think you may be pregnant during treatment with TYENNE.
- are breastfeeding or plan to breastfeed. It is not known if TYENNE passes into your breast milk. Talk to your healthcare provider about the best way to feed your baby if you take TYENNE.

Tell your healthcare provider about all of the medicines you take, including prescription, over-the-counter medicines, vitamins, and herbal supplements. TYENNE and other medicines may affect each other causing side effects.
Especially tell your healthcare provider if you take:

- any other medicines to treat your RA. You should not take etanercept (Enbrel), adalimumab (Humira), infliximab (Remicade), rituximab (Rituxan), abatacept (Orencia), anakinra (Kineret), certolizumab (Cimzia), or golimumab (Simponi) while you are taking TYENNE. Taking TYENNE with these medicines may increase your risk of infection.
- medicines that affect the way certain liver enzymes work. Ask your healthcare provider if you are not sure if your medicine is one of these.

Know the medicines you take. Keep a list of them to show to your healthcare provider and pharmacist when you get a new medicine.

How will I receive TYENNE?
Into a vein (IV or intravenous infusion) for Rheumatoid Arthritis, Giant Cell Arteritis, PJIA, SJIA, CRS, or COVID-19:

- If your healthcare provider prescribes TYENNE as an IV infusion, you will receive TYENNE from a healthcare provider through a needle placed in a vein in your arm. The infusion will take about 1 hour to give you the full dose of medicine.
- For rheumatoid arthritis, giant cell arteritis or PJIA you will receive a dose of TYENNE about every 4 weeks.
- For SJIA you will receive a dose of TYENNE about every 2 weeks.
- For CRS you will receive a single dose of TYENNE, and if needed, additional doses.
- For COVID-19, you will receive a single dose of TYENNE, and if needed one additional dose.
- While taking TYENNE, you may continue to use other medicines that help treat your rheumatoid arthritis, PJIA, SJIA or COVID-19 such as methotrexate, non-steroidal anti-inflammatory drugs (NSAIDs) and prescription steroids, as instructed by your healthcare provider.
- Keep all of your follow-up appointments and get your blood tests as ordered by your healthcare provider.

Under the skin (SC or subcutaneous injection) for Rheumatoid Arthritis, Giant Cell Arteritis, PJIA or SJIA:

- See the Instructions for Use at the end of this Medication Guide for instructions about the right way to prepare and give your TYENNE injections at home.
- TYENNE is available as a single-dose prefilled syringe or single-dose prefilled autoinjector.
- You may also receive TYENNE as an injection under your skin (subcutaneous). If your healthcare provider decides that you or a caregiver can give your injections of TYENNE at home, you or your caregiver should receive training on the right way to prepare and inject TYENNE. Do not try to inject TYENNE until you have been shown the right way to give the injections by your healthcare provider.
- For PJIA or SJIA, you may self-inject with the prefilled syringe or prefilled autoinjector, or your caregiver can give you TYENNE, if both your healthcare provider and parent/legal guardian find it appropriate.
- Your healthcare provider will tell you how much TYENNE to use and when to use it.

What are the possible side effects with TYENNE?
TYENNE can cause serious side effects, including:

- See “What is the most important information I should know about TYENNE?”
- Hepatitis B infection in people who carry the virus in their blood. If you are a carrier of the hepatitis B virus (a virus that affects the liver), the virus may become active while you use TYENNE. Your healthcare provider may do blood tests before you start treatment with TYENNE and while you are using TYENNE. Tell your healthcare provider if you have any of the following symptoms of a possible hepatitis B infection:

  - feel very tired
  - vomiting
  - chills
  - dark urine

  - skin or eyes look yellow
  - clay-colored bowel movements
  - stomach discomfort
  - skin rash

  - little or no appetite
  - fevers
  - muscle aches

- Serious Allergic Reactions: Serious: Allergic Reactions. Serious allergic reactions, including death, can happen with TYENNE. These reactions can happen with any infusion or injection of TYENNE, even if they did not occur with an earlier infusion or injection. Stop taking TYENNE, contact your healthcare provider, and get emergency help right away if you have any of the following signs of a serious allergic reaction:
  - swelling of your face, lips, mouth, or tongue
  - trouble breathing
  - wheezing
  - severe itching
  - skin rash, hives, redness, or swelling outside of the injection site are
  - dizziness or fainting
  - fast heartbeat or pounding in your chest (tachycardia)
  - sweating
- Nervous system problems. While rare, Multiple Sclerosis has been diagnosed in people who take TYENNE. It is not known what effect TYENNE may have on some nervous system disorders.

The most common side effects of TYENNE include:

- upper respiratory tract infections (common cold, sinus infections)
- headache
- increased blood pressure (hypertension)
- injection site reactions

Tell your healthcare provider about any side effect that bothers you or does not go away. These are not all the possible side effects of TYENNE. For more information, ask your healthcare provider or pharmacist.

Call your doctor for medical advice about side effects. You may report side effects to FDA at 1-800-FDA-1088.
You may also report side effects to Fresenius Kabi USA, LLC at 1-800-551-7176.
General information about the safe and effective use of TYENNE.
Medicines are sometimes prescribed for purposes other than those listed in a Medication Guide. Do not give TYENNE to other people, even if they have the same symptoms that you have. It may harm them. You can ask your pharmacist or healthcare provider for information about TYENNE that is written for health professionals.
For more information go to www.TYENNE.com or you can enroll in a patient support program by calling 1-833-522-4227 or visiting the patient support program website: www.kabicare.com.

What are the ingredients in TYENNE?
Active ingredient: tocilizumab-aazg.
Inactive ingredients of Intravenous and Subcutaneous TYENNE: arginine, histidine, hydrochloric acid, lactic acid, polysorbate 80, sodium chloride, sodium hydroxide and Water for Injection.
TYENNE is a registered trademark of Fresenius Kabi
Manufactured by: Fresenius Kabi USA LLC, Lake Zurich, IL 60047, U.S.A
U.S License Number 2146

This Medication Guide has been approved by the U.S. Food and Drug Administration Revised: 02/2025

INSTRUCTIONS FOR USE

Read and follow the Instructions for Use that come with your TYENNE autoinjector before you start using it and each time you get a refill. There may be new information. This information does not replace talking to your healthcare provider about your medical condition or treatment.

If you have any questions about using your TYENNE autoinjector, please call your healthcare provider or Company at 1-833-522-4227.

Important information

- Read the Medication Guide that comes with your autoinjector for important information you need to know before using it.
- Before you use the autoinjector for the first time, make sure your healthcare provider shows you the right way to use it.
- Do not try to take apart the TYENNE autoinjector at any time.
- Always inject TYENNE the way your healthcare provider taught you to.

Using the TYENNE autoinjector

- The autoinjector is for self-injection or administration with the help of a caregiver.
- The autoinjector is for use at home.
- When injecting TYENNE, children may self-inject if both the healthcare provider and caregiver find it appropriate.
- Do not reuse the autoinjector. The autoinjector is for single-dose (1-time) use only.
- Do not share your autoinjector with another person. You may give another person an infection or get an infection from them.
- Do not remove the autoinjector clear cap until you are ready to inject.
- Do not use the autoinjector if it shows any signs of damage or if it has been dropped.

Storing TYENNE autoinjectors

- Store TYENNE in the refrigerator between 36°F to 46°F (2°C to 8°C).
- Store unused autoinjectors in the original carton to protect from light.
- Do not freeze TYENNE. Do not use TYENNE if frozen. Throw away (dispose of) in a sharps disposal container.
- Do not expose TYENNE to heat or direct sunlight.
- Keep the autoinjector out of the reach of children.
- TYENNE may be stored at room temperature at or below 77°F (25°C) in the original carton for up to 14 days. Throw away (dispose of) TYENNE in a sharp disposal container if it has been out of the refrigerator more than 14 days. After being stored at room temperature, do not place it back in the refrigerator.
  See the Medication Guide for more information.

Traveling with TYENNE autoinjector

- When travelling on an airplane, always check with your airline and your healthcare provider about bringing injectable medicine with you. Always carry TYENNE in your carry-on luggage because the airplane luggage area can be very cold and TYENNE could freeze.

Your TYENNE autoinjector

Before Use

After Use

1.1. Prepare a clean, flat surface, such as a table or countertop, in a well-lit area.

1.2. Gather the following supplies (not included) (see Figure A):

- A sterile cotton ball or gauze
- An alcohol pad
- An FDA-cleared sharps disposal container (see Step 8, “Throw away your autoinjector”).

1.3. Remove the carton containing the autoinjector from the refrigerator.

1.4. Check the expiration date on the carton to make sure the date has not passed (see Figure B). Do not use the autoinjector if the expiration date has passed.
1.5. Check to make sure that the carton is properly sealed and is not damaged. Do not use the Autoinjector if the carton looks like it has already been opened or damaged.

1.6. Remove the tray from the carton.

1.7. Let the tray with the autoinjector sit on the prepared surface for 45 minutes before use to allow the medicine in the autoinjector to reach room temperature (see Figure C).

Note: Not doing so could cause your injection to feel uncomfortable and it could take longer to inject.
Do not warm in any other way, such as in a microwave, hot water, or direct sunlight.

1.8. Turn the tray upside down to remove the single-dose autoinjector (see Figure D).

Do not remove the clear cap of the autoinjector until you are ready to inject to avoid injury.

2.1 Check the autoinjector to make sure it is not cracked or damaged (see Figure E).

Do not use if the autoinjector shows signs of damage or if it has been dropped.

2.2 Check the autoinjector label to make sure that:

- The name on the autoinjector says TYENNE
- The expiration date (EXP) on the autoinjector has not passed (see Figure F)

Do not use the autoinjector if the name on the label is not TYENNE or the expiration date on the label has passed.

2.3 Look at the medicine in the viewing window.
Make sure it is clear and colorless to pale yellow and does not contain flakes or particles (see Figure G).

Note: Air bubbles in the medicine are normal.

Do not inject if the liquid is cloudy, discolored, or has lumps or particles in it because it may not be safe to use.

3.1 Wash your hands well with soap and water, then dry them with a clean towel (see Figure H).

4.1 If you are giving yourself the injection, you can use:

- The front of your upper thigh
- The belly (abdomen), except within 2 in (5 cm) around the belly button (navel)

If a caregiver is giving the injection, they can use the outer area of the upper arm (see Figure I).

Note: Choose a different site for each injection to reduce redness, irritation, or other skin problems.

Do not inject into skin that is sore (tender), bruised, red, hard, scaly, or has lesions, moles, scars, or stretch marks or tattoos.
Do not use the autoinjector through clothing.

5.1 Wipe the skin where you want to inject with an alcohol pad to clean it (see Figure J). Let the skin dry.
Do not blow on or touch the site after cleaning.

6.1 When you are ready to inject, hold the autoinjector in one hand with the clear cap on top, pointing straight up.
Using your other hand, firmly pull the clear cap straight off without twisting (see Figure K).

Note: Use the autoinjector within 3 minutes after removing the cap to avoid contamination.

Do not try to recap the needle at any time, even at the end of the injection.

Do not touch the needle cover (the orange part located at the tip of the autoinjector) because this might cause an accidental needle stick.

6.2 Throw away the clear cap in a sharps disposal container.

6.3 Rotate the autoinjector so that the orange needle cover points downwards.

6.4 Position your hand on the autoinjector so that you can see the window.

6.5 Place the needle cover flat against your skin at a 90-degree angle (see Figure L).
Note: To make sure you inject under the skin (into fatty tissue), do not hold the autoinjector at an angle.

Do not pinch your skin.

To make sure you inject the full dose, read all of the steps from 6.6 to 6.9 before you start:

6.6 In a single motion, push and hold the autoinjector firmly against your skin until you hear a first click. This means the injection has started (see Figure M).
The orange plunger rod will move through the window during the injection.

6.7 Hold the autoinjector in place until you hear a second click. This may take up to 10 seconds. (see Figure N).
6.8 Wait and slowly count to 5 after you hear the second click. Continue to hold the autoinjector in place to make sure you inject a full dose (see Figure O). Do not lift the autoinjector until you are sure 5 seconds has passed, and the injection is complete.

6.9 While holding the autoinjector in place, check the window to make sure the orange plunger rod has fully appeared in the viewing window, and has stopped moving (see Figure P).

7.1 When the injection is complete, lift the autoinjector straight away from your skin (see Figure Q).

Note: The needle cover will slide down and cover the needle.

Do not recap the autoinjector.

7.2 Check the window to make sure the orange plunger rod came all the way down (see Figure R).

Note: If the orange plunger rod did not come all the way down or you believe you did not get a full injection, call your healthcare provider.
Do not try to repeat the injection with a new autoinjector.

7.3 If you see blood on the injection site, press gauze or a cotton ball against on the skin until the bleeding stops (see Figure S).

Do not rub the injection site.

8.1 Put your used autoinjector in an FDA-cleared sharps disposal container right away after use (see Figure T).

Do not throw away (dispose of) your autoinjector in your household trash.
If you do not have a FDA-cleared sharps disposal container, you can use a household container that is:

- made of a heavy-duty plastic,
- can be closed with a tight-fitting, puncture-resistant lid, without sharps being able to come out,
- upright and stable during use,
- leak-resistant, and
- properly labeled to warn of hazardous waste inside the container.

When your sharps disposal container is almost full, you will need to follow your community guidelines for the right way to dispose of your sharps disposal container. There may be state or local laws about how you should throw away used needles and syringes.

For more information about safe sharps disposal, and for specific information about sharps disposal in the state that you live in, go to the FDA's website at http://www.fda.gov/safesharpsdisposal

Do not throw away (dispose of) your used sharps disposal container in your household trash unless your community guidelines permit this.

Do not recycle your used sharps disposal container.

Always keep the sharps disposal container out of reach of children.

9.1 Write the date, time, and specific part of your body where you injected yourself (see Figure U).
It may also be helpful to write any questions or concerns about the injection, so you can ask your healthcare provider.

Manufactured by:
Fresenius Kabi USA, LLC
Lake Zurich, Illinois 60047
U.S. License No. 2146

This Instructions for Use has been approved by the U.S. Food and Drug Administration Revised: 02/2025

Read and follow the Instructions for Use that come with your TYENNE prefilled syringe before you start using it and each time you get a refill. There may be new information. This does not replace talking to your healthcare provider about your medical condition or treatment.

If you have any questions about using your TYENNE prefilled syringe, please call your healthcare provider or Company at 1-833-522-4227.

Important Information

- Read the Medication Guide that comes with your TYENNE prefilled syringe for important information you need to know before using it.
- Before you use the prefilled syringe for the first time, make sure your healthcare provider shows you the right way to use it.
- Do not remove the needle cap until you are ready to inject TYENNE.
- Do not try to take apart the prefilled syringe at any time.
- Always inject TYENNE the way your healthcare provider taught you.

Using TYENNE prefilled syringe

- The prefilled syringe is for self-injection or administration with the help of a caregiver.
- Do not use the prefilled syringe if the carton is open or damaged.
- Do not use the prefilled syringe if it has been dropped on a hard surface.
  The prefilled syringe may be broken even if you cannot see the break.

Storing TYENNE prefilled syringes

- Store TYENNE in the refrigerator between 36°F to 46°F (2°C to 8°C).
- Store unused prefilled syringes in the original carton to protect from light.
- Keep the prefilled syringes out of the reach of children.
- Do not freeze TYENNE. Do not use TYENNE if frozen. Throw away (dispose of) in a sharps disposal container.
- Do not expose TYENNE to heat or direct sunlight.
- If needed, for example when traveling, TYENNE may be stored at room temperature at or below 77°F (25°C) in the original carton for up to 14 days. Throw away (dispose of) TYENNE in a sharps disposal container if it has been out of the refrigerator for more than 14 days. After being stored at room temperature, do not place it back in the refrigerator.

See the Medication Guide for more information.

Your TYENNE prefilled syringe (see Figure A)

Do not try to activate the clear needle guard before injecting.

Do not insert your fingers into the opening of the clear needle guard because the needle could injure you.

1.1 Find a comfortable space with a clean, flat working surface.

1.2 Supplies needed for your TYENNE prefilled syringe injection (see Figure B):

- TYENNE prefilled syringe
- An alcohol pad
- A sterile cotton ball or gauze
- Puncture-resistant container or sharps container for safe disposal of used syringe (see Step 7 “Throw away used prefilled syringe”)

1.3 Take the box containing the syringe out of the refrigerator and open the box (see Figure C).

1.4 Remove the plastic tray out of the box and let it warm up for 30 minutes to reach room temperature (see Figure D). If the syringe does not reach room temperature, this could cause your injection to feel uncomfortable and make it difficult to push the plunger in.

- Do not speed up the warming process in any way, such as in a microwave or placing the syringe in hot water.
- Prepare and check your records of previous injection sites. This will help you choose the appropriate injection site for this injection (see Step 8 “Record your injection”).

Remove TYENNE prefilled syringe from the plastic tray

- Place two fingers on either side, in the middle of the clear needle guard.
- Pull the prefilled syringe straight up and out of the tray (see Figure E).
- Do not pick up the prefilled syringe by the plunger or the needle cap. Doing so could damage the prefilled syringe or activate the clear needle guard.

2.1 Check the expiration date on the TYENNE prefilled syringe (see Figure F).

Do not use it if the expiration date has passed because it may not be safe to use. If the expiration date has passed, safely dispose of the syringe in a sharps container and get a new one.

2.2 Check the name on the prefilled syringe says TYENNE (see Figure F).

2.3 Check the liquid in the TYENNE prefilled syringe. It should be clear and colorless to pale yellow (see Figure G).

Do not inject TYENNE if the liquid is cloudy, discolored or has lumps or particles in it because it may not be safe to use. Safely dispose of the syringe in a sharps container and get a new one.

2.4 Check the prefilled syringe to make sure that:

- The prefilled syringe, the clear needle guard, and the needle cap are not cracked or damaged (see Figure H).
- The needle cap is securely attached (see Figure I).
- The needle guard spring is not extended (see Figure J).
- Do not use the syringe if it shows any sign of damage. If damaged, call your healthcare provider or pharmacist right away and throw away the syringe in your sharps disposal container (see Step 7 “Throw away used prefilled syringe”).

Wash your hands well with soap and water (see Figure K).

4.1 Choose an injection site

- The front of the thighs and your belly (abdomen) except for 2-inch area around your navel are the recommended injection sites (see Figure L).
- The outer area of the upper arms may also be used only if the injection is being given by a caregiver. Do not attempt to use the upper arm area by yourself (see Figure M).

4.2 Rotate injection site

- Choose a different injection site for each new injection.
- Do not inject into moles, scars, bruises, or areas where the skin is tender, red, hard or not intact.

5.1 Clean the injection site

- Wipe the injection site with an alcohol pad in a circular motion and let it air dry to reduce the chance of getting an infection. Do not touch the injection site again before giving the injection.
- Do not fan or blow on the clean area.

6.1 Remove the needle cap.

Hold the TYENNE prefilled syringe by the clear needle guard with 1 hand and pull the needle cap straight off with your other hand (see Figure N).
3. Do not hold the plunger while you remove the needle cap. If you cannot remove the needle cap, you should ask a caregiver for help or contact your healthcare provider.
4. Throw away the needle cap in your sharps container.
5. There may be a small air bubble in the TYENNE prefilled syringe. You do not need to remove it.
6. You may see drops of liquid at the end of the needle. This is normal and will not affect your dose.
7. Do not touch the needle or let it touch any surfaces.
8. Do not use the prefilled syringe if it is dropped.
9. If it is not used within 5 minutes of needle cap removal, the syringe should be disposed of in the puncture resistant container or sharps container and a new syringe should be used.
10. Never reattach the needle cap after removal.

6.2 Pinch the skin

- Hold the TYENNE prefilled syringe in 1 hand between the thumb and index finger (see Figure O).
- Do not pull back on the plunger of the syringe.
- Use your other hand and gently pinch the area of skin firmly (see Figure P). Pinching the skin is important to make sure that you inject under the skin (into fatty tissue) but not any deeper (into muscle). Injection into muscle could cause the injection to feel uncomfortable.

6.3 Insert the needle

- Use a quick, dart-like motion to insert the needle all the way into the pinched skin at an angle between 45° to 90° (see Figure Q). It is important to use the correct angle to make sure the medicine is delivered under the skin (into fatty tissue), or the injection could be painful, and the medicine may not work.
- Keep the syringe in position.
- Do not hold or push on the plunger while inserting the needle into the skin.

6.4 Inject

- Slowly inject all of the medicine by gently pushing the plunger all the way down (see Figure R).
- You must press the plunger all the way down to get the full dose of medicine until you cannot press any more (see Figure S).
- Do not pull the needle out of the skin when the plunger is pushed all the way down.

6.5 Finish Injection

- After the plunger is pushed all the way down, hold the syringe firmly without moving it, at the same angle as inserted.
- Slowly release your thumb off the plunger. The plunger will move up. The safety system will remove the needle from the skin and cover the needle (see Figure T).
- Release the pinched skin

Important: Call your healthcare provider right away if you did not inject the full dose. Injecting an incorrect amount of medicine could affect your treatment.

Do not reuse a syringe even if all of the medicine was not injected.

Do not try to recap the needle as it could lead to needle stick injury.

6.6 After the injection

- There may be a little bleeding at the injection site. You can press a cotton ball or gauze on the injection site.
- Do not rub the injection site.
- If needed, you may cover the injection site with a small bandage.

- The TYENNE prefilled syringe should not be reused.
- Do not put the needle cap back on the needle
- If your injection is given by another person, this person must also be careful when removing the syringe and disposing of the syringe to prevent accidental needle stick injury and passing injection.

How do I throw away used syringes?

Put your used syringe in an FDA-cleared sharps disposal container right away after use (see Figure U). Do not throw away (dispose of) loose needles and syringes in your household trash.

- If you do not have an FDA-cleared sharps disposal container, you may use a household container that is:
  - made of a heavy-duty plastic,
  - can be closed with a tight-fitting, puncture-resistant lid, without sharps being able to come out,
  - upright and stable during use,
  - leak-resistant and
  - properly labeled to warn of hazardous waste inside the container.
    - When your sharps disposal container is almost full, you will need to follow your community guidelines for the right way to dispose of your sharps disposal container. There may be state or local laws about how you should throw away used syringes. For more information about safe sharps disposal, and for specific information about sharps disposal in the state you live in, go to the FDA's website at: http://www.fda.gov/safesharpsdisposal
    - Do not throw away (dispose of) your used sharps disposal container in your household trash unless your community guidelines permit this. Do not recycle your used sharps disposal container.

Keep TYENNE prefilled syringes and disposal container out of the reach of children.

Write the date, time, and specific part of your body where you injected yourself (see Figure V).

It may also be helpful to write any questions or concerns about the injection, so you can ask your healthcare provider.

Manufactured by:
Fresenius Kabi USA, LLC
Lake Zurich, Illinois 60047

U.S. License No. 2146

This Instructions for Use has been approved by the U.S. Food and Drug Administration Revised: 02/2025

Principal Display Panel – 0.9 mL Prefilled syringe – Primary Label

NDC 65219-586-04 Rx only

Tyenne®
(tocilizumab-aazg)
Injection

162 mg / 0.9 mL

For Subcutaneous
Use Only

Fresenius Kabi USA, LLC

Principal Display Panel – 0.9 mL Prefilled syringe - Carton

NDC 65219-586-04 Rx only

Tyenne®
tocilizumab-aazg

Injection

162 mg / 0.9 mL

For Subcutaneous Use Only

1 single-dose prefilled syringe 0.9 mL

Carton contains:
1 single-dose prefilled syringe - Discard Unused Portion
1 Prescribing Information
1 Medication Guide
1 Instruction for Use

Dispense the enclosed
Medication Guide to each patient

Sterile Solution - No Preservative

Refrigerate Immediately

Principal Display Panel – 0.9 mL Autoinjector – Primary Label

NDC 65219-584-01 Rx only

Tyenne®
(tocilizumab-aazg)
Injection

162 mg / 0.9 mL

For Subcutaneous Use Only

Fresenius Kabi USA, LLC

Principal Display Panel – 0.9 mL Autoinjector - Carton

NDC 65219-584-01 Rx only

Tyenne®
tocilizumab-aazg

Injection

162 mg / 0.9 mL

For Subcutaneous Use Only

1 single-dose autoinjector 0.9 mL

Carton contains:
1 single-dose autoinjector - Discard Unused Portion
1 Prescribing Information
1 Medication Guide
1 Instruction for Use

Dispense the enclosed Medication Guide to each patient

Refrigerate Immediately
Sterile Solution - No Preservative